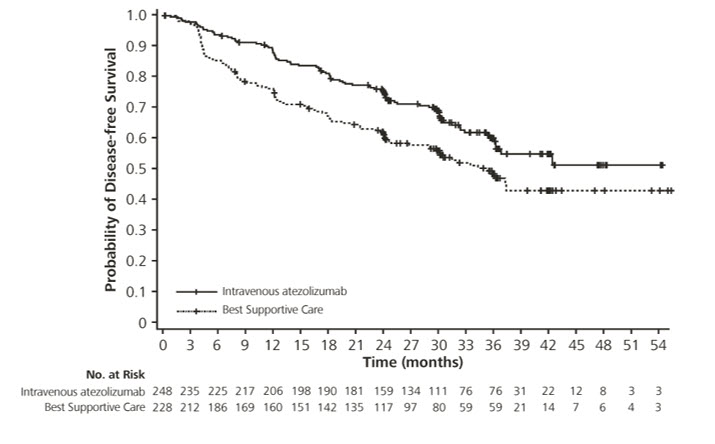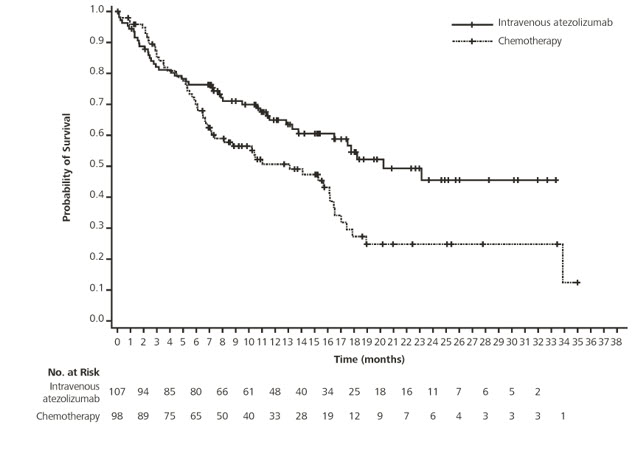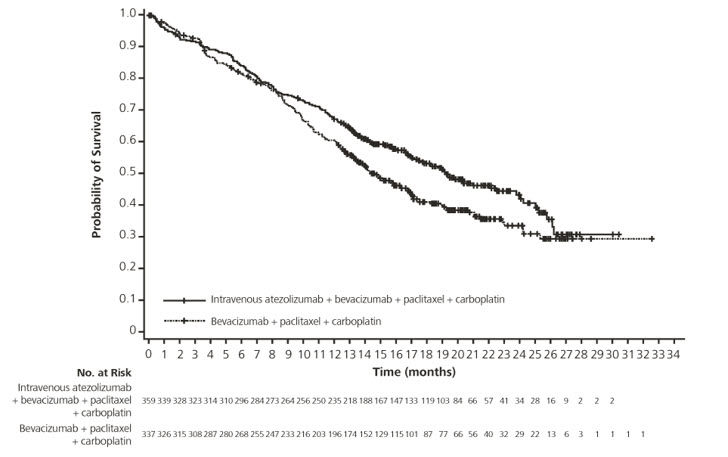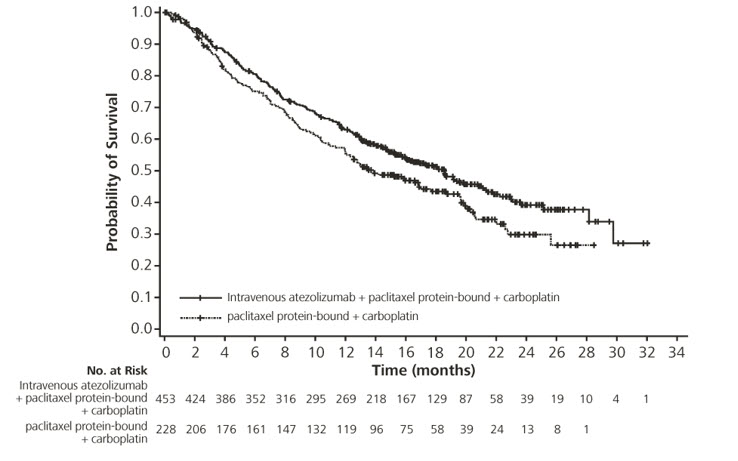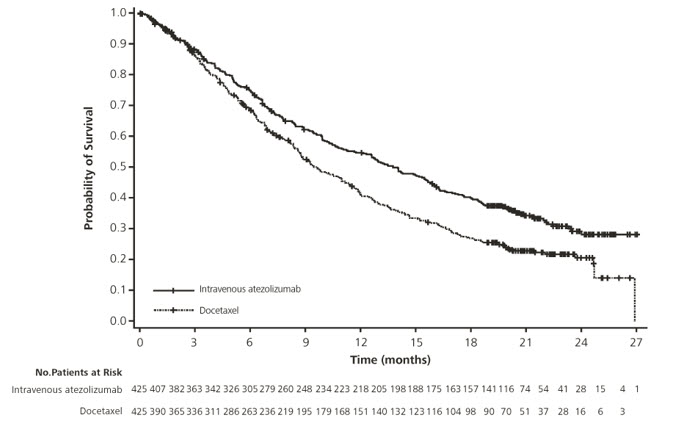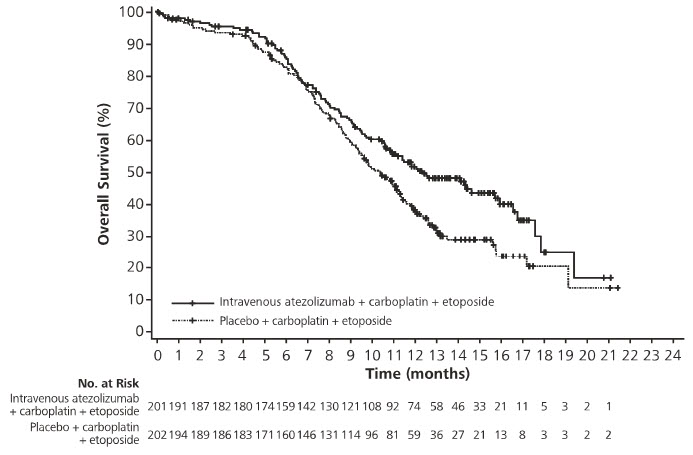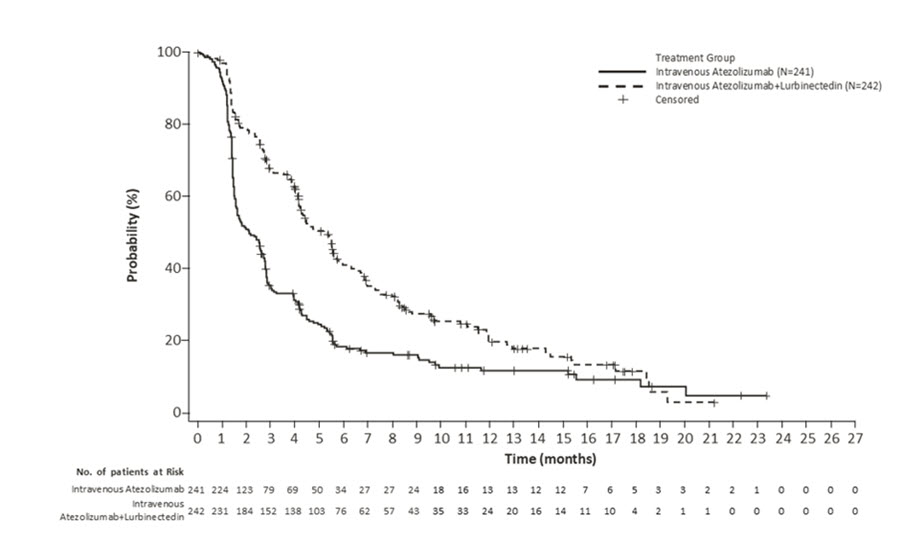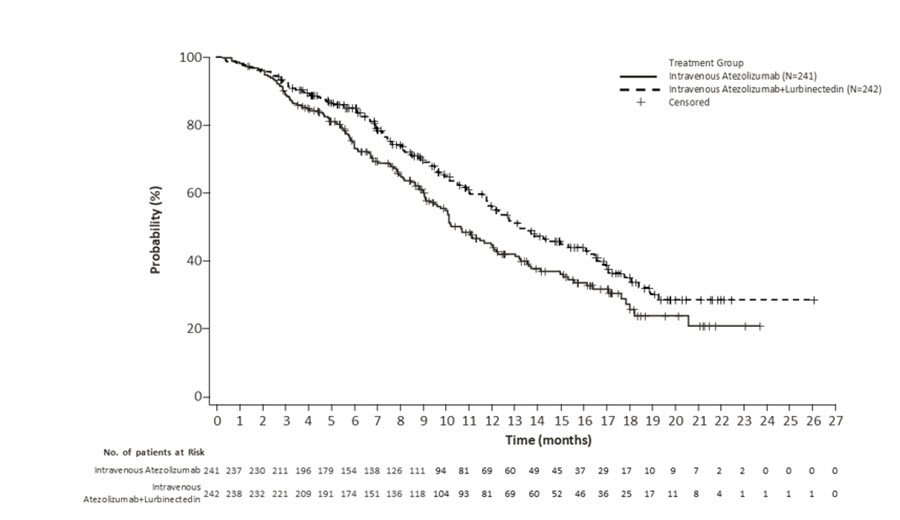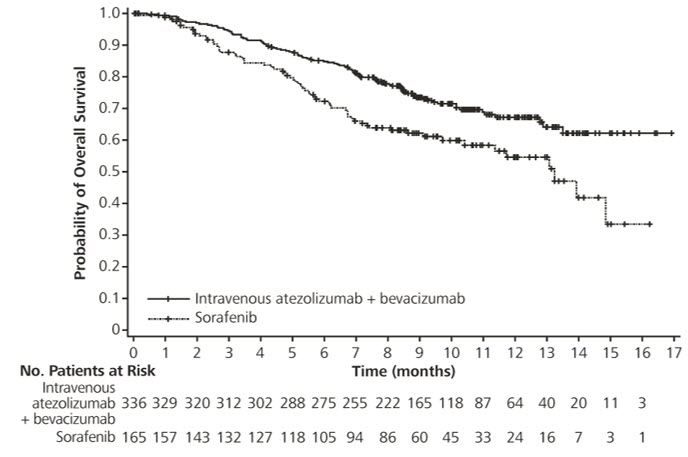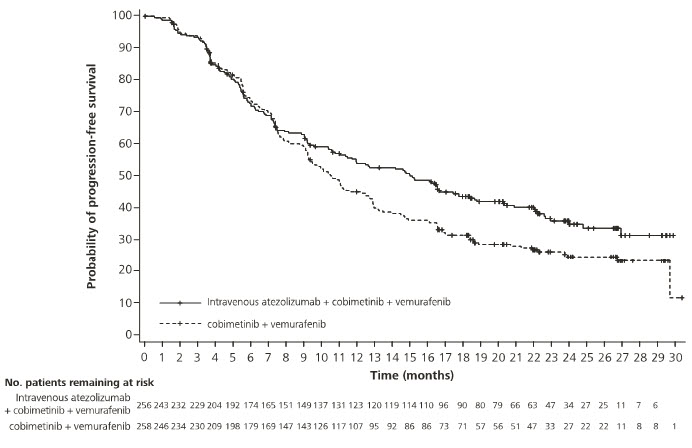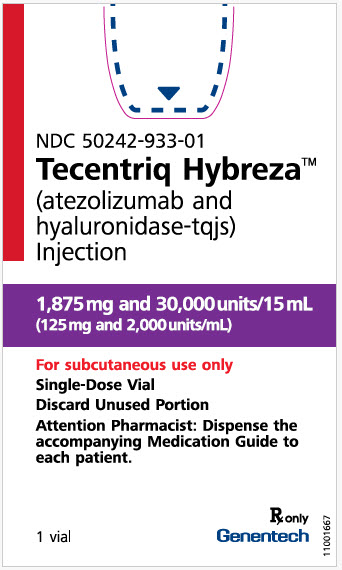 DRUG LABEL: Tecentriq Hybreza
NDC: 50242-933 | Form: INJECTION
Manufacturer: Genentech, Inc.
Category: prescription | Type: HUMAN PRESCRIPTION DRUG LABEL
Date: 20251203

ACTIVE INGREDIENTS: ATEZOLIZUMAB 1875 mg/15 mL; HYALURONIDASE (HUMAN RECOMBINANT) 30000 U/15 mL
INACTIVE INGREDIENTS: HISTIDINE 46.5 mg/15 mL; SUCROSE 1232 mg/15 mL; POLYSORBATE 20 9 mg/15 mL; METHIONINE 22.4 mg/15 mL; ACETIC ACID; WATER

HIGHLIGHTS OF PRESCRIBING INFORMATION

These highlights do not include all the information needed to use TECENTRIQ HYBREZA safely and effectively. See full prescribing information for TECENTRIQ HYBREZA.
TECENTRIQ HYBREZA® (atezolizumab and hyaluronidase-tqjs) injection, for subcutaneous use
Initial U.S. Approval: 2024

RECENT MAJOR CHANGES

Indications and Usage (1.2, 1.5) | 11/2025
Dosage and Administration, Important Dosage and Administration Information (2.2, 2.3) | 11/2025
Warnings and Precautions (5.2) | 8/2025

1 INDICATIONS AND USAGE

TECENTRIQ HYBREZA is a combination of atezolizumab, a programmed death-ligand 1 (PD-L1) blocking antibody, and hyaluronidase, an endoglycosidase indicated:

Non-Small Cell Lung Cancer (NSCLC)

- as adjuvant treatment following resection and platinum-based chemotherapy for adult patients with Stage II to IIIA NSCLC whose tumors have PD-L1 expression on ≥ 1% of tumor cells, as determined by an FDA-approved test. (1.1)
- for the first-line treatment of adult patients with metastatic NSCLC whose tumors have high PD-L1 expression (PD-L1 stained ≥ 50% of tumor cells [TC ≥ 50%] or PD-L1 stained tumor-infiltrating immune cells [IC] covering ≥ 10% of the tumor area [IC ≥ 10%]), as determined by an FDA-approved test, with no EGFR or ALK genomic tumor aberrations. (1.1)
- in combination with bevacizumab, paclitaxel, and carboplatin, for the first-line treatment of adult patients with metastatic non-squamous NSCLC with no EGFR or ALK genomic tumor aberrations. (1.1)
- in combination with paclitaxel protein-bound and carboplatin for the first-line treatment of adult patients with metastatic non-squamous NSCLC with no EGFR or ALK genomic tumor aberrations. (1.1)
- for the treatment of adult patients with metastatic NSCLC who have disease progression during or following platinum-containing chemotherapy. Patients with EGFR or ALK genomic tumor aberrations should have disease progression on FDA-approved therapy for NSCLC harboring these aberrations prior to receiving TECENTRIQ HYBREZA. (1.1)

Small Cell Lung Cancer (SCLC)

- in combination with carboplatin and etoposide, for the first-line treatment of adult patients with extensive-stage small cell lung cancer (ES-SCLC). (1.2)
- in combination with lurbinectedin, for the maintenance treatment of adult patients with ES-SCLC whose disease has not progressed after first-line induction therapy with TECENTRIQ HYBREZA or intravenous atezolizumab, and carboplatin plus etoposide. (1.2)

Hepatocellular Carcinoma (HCC)

- in combination with bevacizumab for the treatment of adult patients with unresectable or metastatic HCC who have not received prior systemic therapy. (1.3)

Melanoma

- in combination with cobimetinib and vemurafenib for the treatment of adult patients with BRAF V600 mutation-positive unresectable or metastatic melanoma as determined by an FDA-approved test. (1.4)

Alveolar Soft Part Sarcoma (ASPS)

- for the treatment of adult patients and pediatric patients (12 years of age and older who weigh 40 kg or greater) with unresectable or metastatic ASPS. (1.5)

2 DOSAGE AND ADMINISTRATION

- TECENTRIQ HYBREZA has different recommended dosage and administration than intravenous atezolizumab products. (2.2)
- TECENTRIQ HYBREZA is for subcutaneous use in the thigh only. (2.2)
- Do not administer TECENTRIQ HYBREZA intravenously. (2.2)
- The recommended dosage for adult patients and pediatric patients (12 years and older who weigh 40 kg or greater) is: TECENTRIQ HYBREZA 15 mL (1,875 mg atezolizumab and 30,000 units hyaluronidase) subcutaneously into the thigh over approximately 7 minutes every 3 weeks. (2.2)
- TECENTRIQ HYBREZA must be administered by a healthcare professional. (2.2)

NSCLC Dosage

- In the adjuvant setting, administer TECENTRIQ HYBREZA following resection and up to 4 cycles of platinum-based chemotherapy every 3 weeks for up to 1 year. (2.2)
- In the metastatic setting, administer TECENTRIQ HYBREZA every 3 weeks. (2.2)
- When administering with chemotherapy with or without bevacizumab, administer TECENTRIQ HYBREZA prior to chemotherapy and bevacizumab when given on the same day. (2.2)

SCLC Dosage

Administer TECENTRIQ HYBREZA every 3 weeks. Administer TECENTRIQ HYBREZA prior to chemotherapy when given on the same day. (2.2)

HCC Dosage

- Administer TECENTRIQ HYBREZA every 3 weeks.
- Administer TECENTRIQ HYBREZA prior to bevacizumab when given on the same day. Bevacizumab is administered intravenously at 15 mg/kg every 3 weeks. (2.2)

Melanoma Dosage

- Following completion of a 28-day cycle of cobimetinib and vemurafenib, administer TECENTRIQ HYBREZA every 3 weeks with cobimetinib 60 mg orally once daily (21 days on /7 days off) and vemurafenib 720 mg orally twice daily. (2.2)

ASPS Dosage

- Administer TECENTRIQ HYBREZA every 3 weeks. (2.2)

3 DOSAGE FORMS AND STRENGTHS

Injection: 1,875 mg atezolizumab and 30,000 units hyaluronidase per 15 mL (125 mg/2,000 units per mL) solution in a single-dose vial. (3)

4 CONTRAINDICATIONS

TECENTRIQ HYBREZA is contraindicated in patients with known hypersensitivity to hyaluronidase or any of its excipients. (4)

5 WARNINGS AND PRECAUTIONS

- Immune-Mediated Adverse Reactions
  - Immune-mediated adverse reactions, which may be severe or fatal, can occur in any organ system or tissue, including the following: immune-mediated pneumonitis, immune-mediated colitis, immune-mediated hepatitis, immune-mediated endocrinopathies, immune-mediated dermatologic adverse reactions, immune-mediated nephritis and renal dysfunction, and solid organ transplant rejection. (5.1)
  - Monitor for early identification and management. Evaluate liver enzymes, creatinine, and thyroid function at baseline and periodically during treatment.
  - Withhold or permanently discontinue based on severity and type of reaction.
- Infusion-Related Reactions: Pause or slow the rate of injection, or permanently discontinue based on severity of the reaction. (5.2)
- Complications of Allogeneic HSCT: Fatal and other serious complications can occur in patients who receive allogeneic HSCT before or after being treated with a PD-1/PD-L1 blocking antibody. Follow patients closely for evidence of transplant-related complications and intervene promptly. (5.3)
- Embryo-Fetal Toxicity: Can cause fetal harm. Advise females of reproductive potential of the potential risk to a fetus and use of effective contraception. (5.4, 8.1, 8.3)

6 ADVERSE REACTIONS

- Most common adverse reactions (AR) (≥ 10%) with TECENTRIQ HYBREZA as monotherapy in patients with NSCLC were fatigue, musculoskeletal pain, cough, dyspnea, and decreased appetite. (6.1)
- Safety of TECENTRIQ HYBREZA for the approved NSCLC, EC-SCLC, HCC, melanoma and ASPS indications is based on safety of intravenous atezolizumab in these populations. Most common AR with intravenous atezolizumab are presented below by indication and regimen (6.1):

Most common AR (≥ 20%) as monotherapy were:
  - First-line NSCLC: fatigue/asthenia.
  - Metastatic NSCLC: fatigue/asthenia, cough, decreased appetite, dyspnea, and myalgia/pain.
  - ASPS: musculoskeletal pain, fatigue, rash, cough, headache, nausea, hypertension, vomiting, constipation, dyspnea, dizziness, hemorrhage, diarrhea, insomnia, abdominal pain hypothyroidism, pyrexia, anxiety, arrhythmia and decreased appetite.
Most common AR (≥ 20%) in combination with other antineoplastic drugs were:
  - NSCLC (with bevacizumab, paclitaxel, and carboplatin): neuropathy fatigue/asthenia, alopecia, myalgia, nausea, diarrhea, constipation, decreased appetite, arthralgia, hypertension, rash, cough.
  - Non-squamous NSCLC (with paclitaxel protein-bound and carboplatin): fatigue/asthenia, nausea, diarrhea, myalgia/pain, constipation, neuropathy, alopecia, dyspnea, decreased appetite, cough, vomiting and rash.
  - SCLC (with chemotherapy): fatigue/asthenia, nausea, alopecia, decreased appetite, constipation and vomiting.
  - HCC (with bevacizumab): hypertension, fatigue and proteinuria.
  - Melanoma (with cobimetinib and vemurafenib): rash, musculoskeletal pain, fatigue, hepatotoxicity, pyrexia, nausea, pruritus, edema, stomatitis, hypothyroidism, and photosensitivity reaction.

To report SUSPECTED ADVERSE REACTIONS, contact Genentech at 1-888-835-2555 or FDA at 1-800-FDA-1088 or www.fda.gov/medwatch.

8 USE IN SPECIFIC POPULATIONS

Lactation: Advise not to breastfeed. (8.2)

FULL PRESCRIBING INFORMATION

1 INDICATIONS AND USAGE

1.1 Non-Small Cell Lung Cancer

- TECENTRIQ HYBREZA, as monotherapy, is indicated as adjuvant treatment following resection and platinum-based chemotherapy for adult patients with stage II to IIIA [see Clinical Studies (14.1)] non-small cell lung cancer (NSCLC) whose tumors have PD-L1 expression on ≥ 1% of tumor cells, as determined by an FDA-approved test [see Dosage and Administration (2.1)].
- TECENTRIQ HYBREZA, as monotherapy, is indicated for the first-line treatment of adult patients with metastatic non-small cell lung cancer (NSCLC) whose tumors have high PD-L1 expression (PD-L1 stained ≥ 50% of tumor cells [TC ≥ 50%] or PD-L1 stained tumor-infiltrating immune cells [IC] covering ≥ 10% of the tumor area [IC ≥ 10%]), as determined by an FDA-approved test, with no EGFR or ALK genomic tumor aberrations [see Dosage and Administration (2.1)].
- TECENTRIQ HYBREZA, in combination with bevacizumab, paclitaxel, and carboplatin, is indicated for the first-line treatment of adult patients with metastatic non-squamous NSCLC with no EGFR or ALK genomic tumor aberrations.
- TECENTRIQ HYBREZA, in combination with paclitaxel protein-bound and carboplatin, is indicated for the first-line treatment of adult patients with metastatic non-squamous NSCLC with no EGFR or ALK genomic tumor aberrations.
- TECENTRIQ HYBREZA, as monotherapy, is indicated for the treatment of adult patients with metastatic NSCLC who have disease progression during or following platinum-containing chemotherapy. Patients with EGFR or ALK genomic tumor aberrations should have disease progression on FDA-approved therapy for NSCLC harboring these aberrations prior to receiving TECENTRIQ HYBREZA.

1.2 Small Cell Lung Cancer

- TECENTRIQ HYBREZA, in combination with carboplatin and etoposide, is indicated for the first-line treatment of adult patients with extensive-stage small cell lung cancer (ES-SCLC).
- TECENTRIQ HYBREZA, in combination with lurbinectedin, is indicated for the maintenance treatment of adult patients with ES-SCLC whose disease has not progressed after first-line induction therapy with TECENTRIQ HYBREZA or intravenous atezolizumab, carboplatin and etoposide.

1.3 Hepatocellular Carcinoma

TECENTRIQ HYBREZA, in combination with bevacizumab, is indicated for the treatment of adult patients with unresectable or metastatic hepatocellular carcinoma (HCC) who have not received prior systemic therapy.

1.4 Melanoma

TECENTRIQ HYBREZA, in combination with cobimetinib and vemurafenib, is indicated for the treatment of adult patients with BRAF V600 mutation-positive unresectable or metastatic melanoma as determined by an FDA-approved test [see Dosage and Administration (2.1)].

1.5 Alveolar Soft Part Sarcoma

TECENTRIQ HYBREZA, as monotherapy, is indicated for the treatment of adult patients and pediatric patients (12 years of age and older who weigh 40 kg or greater) with unresectable or metastatic alveolar soft part sarcoma (ASPS).

2 DOSAGE AND ADMINISTRATION

2.1 Patient Selection for Treatment of Non-Small Cell Lung Cancer and Melanoma

Select adult patients with:

- Stage II to IIIA NSCLC for adjuvant treatment with TECENTRIQ HYBREZA as a monotherapy (following tumor resection and platinum-based chemotherapy) based on PD-L1 expression on tumor cells [see Clinical Studies (14.1)].
- Metastatic NSCLC for first-line treatment with TECENTRIQ HYBREZA as monotherapy based on the PD-L1 expression on tumor cells or on tumor-infiltrating immune cells [see Clinical Studies (14.1)].
- Unresectable or metastatic melanoma for treatment with TECENTRIQ HYBREZA in combination with cobimetinib and vemurafenib after confirming the presence of a BRAF V600 mutation [see Clinical Studies (14.4)].

Information on FDA-approved tests for the determination of PD-L1 expression in metastatic NSCLC or for detection of BRAF V600 mutations in melanoma is available at: http://www.fda.gov/CompanionDiagnostics.

2.2 Important Dosage and Administration Information

- TECENTRIQ HYBREZA has different recommended dosage and administration than intravenous atezolizumab products.
  - To reduce the risk of medication errors, prior to administration, check the vial labels to ensure that the drug being prepared is subcutaneously administered TECENTRIQ HYBREZA and not intravenously administered atezolizumab.
  - Do not substitute TECENTRIQ HYBREZA for or with intravenous atezolizumab products because they have different recommended dosages.
  - Adult patients who are treated with intravenous atezolizumab can switch to subcutaneous TECENTRIQ HYBREZA at their next scheduled dose. Adult patients who are treated with TECENTRIQ HYBREZA can switch to intravenous atezolizumab at their next scheduled dose.
  - Pediatric patients 12 years of age and older who weigh 40 kg or greater and are treated with intravenous atezolizumab can switch to subcutaneous TECENTRIQ HYBREZA at their next scheduled dose [see Indications and Usage (1.5)]. Pediatric patients who are treated with TECENTRIQ HYBREZA can switch to intravenous atezolizumab at their next scheduled dose.
- TECENTRIQ HYBREZA is for subcutaneous use in the thigh only. Administer over approximately 7 minutes. Inject in healthy skin and never into areas where the skin is red, bruised, tender, or hard.
- When possible, alternate injections between the left and right thigh. Ensure the injection site is at least 2.5 cm from the previous site.
- Do not administer TECENTRIQ HYBREZA intravenously.
- TECENTRIQ HYBREZA must be administered by a healthcare professional.
- Do not administer the remaining volume in the tubing to the patient.
- If using concomitant subcutaneous drugs, administer at sites other than the thighs.

2.3 Recommended Dosage and Administration Instructions

The recommended dosage of TECENTRIQ HYBREZA in adult patients and pediatric patients (12 years of age and older who weigh 40 kg or greater) is one 15 mL injection (containing 1,875 mg of atezolizumab and 30,000 units of hyaluronidase, referred to as TECENTRIQ HYBREZA) administered subcutaneously in the thigh over approximately 7 minutes every 3 weeks.

The recommended dosage for pediatric patients 12 years of age and older who weigh less than 40 kg has not been established [see Use in Specific Populations (8.4), Clinical Pharmacology (12.3)].

Administration instructions for TECENTRIQ HYBREZA as monotherapy and in combination with other therapeutic agents are presented in Table 1. For the recommended dosage of each therapeutic agent administered in combination with TECENTRIQ HYBREZA refer to the product's respective Prescribing Information.

Table 1: TECENTRIQ HYBREZA Administration Instructions and Duration of Therapy
Indication | Administration Instructions for TECENTRIQ HYBREZA | Duration of Therapy
Adjuvant Treatment of Non-Small Cell Lung Cancer | Administer TECENTRIQ HYBREZA as monotherapy | Up to one year, unless there is disease recurrence or unacceptable toxicity
Metastatic Non-Small Cell Lung Cancer | Administer TECENTRIQ HYBREZA as monotherapy | Until disease progression or unacceptable toxicity
Non-Small Cell Lung Cancer | Administer TECENTRIQ HYBREZA prior to chemotherapy and bevacizumab when given on the same day. | Until disease progression or unacceptable toxicity
Small Cell Lung Cancer | Administer TECENTRIQ HYBREZA prior to chemotherapy when given on the same day. | Until disease progression or unacceptable toxicity
Hepatocellular Carcinoma | Administer TECENTRIQ HYBREZA prior to bevacizumab when given on the same day. Bevacizumab is administered intravenously at 15 mg/kg every 3 weeks. | Until disease progression or unacceptable toxicity
Melanoma | Prior to initiating TECENTRIQ HYBREZA, patients should receive the following 28-day treatment cycle of cobimetinib and vemurafenib:; - Days 1 to 21: cobimetinib 60 mg orally once daily in combination with 960 mg of oral vemurafenib twice daily - Days 22 to 28: withhold cobimetinib and administer vemurafenib 720 mg orally twice daily | Until disease progression or unacceptable toxicity
Alveolar Soft Part Sarcoma | Administer TECENTRIQ HYBREZA as monotherapy | Until disease progression or unacceptable toxicity

2.4 Dosage Modifications for Adverse Reactions

No dose reduction for TECENTRIQ HYBREZA is recommended. In general, withhold TECENTRIQ HYBREZA for severe (Grade 3) immune-mediated adverse reactions. Permanently discontinue TECENTRIQ HYBREZA for life-threatening (Grade 4) immune-mediated adverse reactions, recurrent severe (Grade 3) immune-mediated reactions that require systemic immunosuppressive treatment, or an inability to reduce the daily corticosteroid dosage to 10 mg or less of prednisone or equivalent corticosteroid dosage within 12 weeks of initiating corticosteroids.

Dosage modifications for TECENTRIQ HYBREZA for adverse reactions that require management different from these general guidelines are summarized in Table 2.

Table 2: Recommended Dosage Modifications for Adverse Reactions
Adverse Reaction | Severity [Based on Common Terminology Criteria for Adverse Events (CTCAE), version 5] | Dosage Modification
Immune-Mediated Adverse Reactions [see Warnings and Precautions (5.1)]
Pneumonitis | Grade 2 | Withhold [Resume in patients with complete or partial resolution (Grade 0 to 1) after corticosteroid taper. Permanently discontinue if no complete or partial resolution within 12 weeks of initiating steroids or inability to reduce prednisone to 10 mg per day or less (or equivalent) within 12 weeks of initiating steroids]
Pneumonitis | Grades 3 or 4 | Permanently discontinue
Colitis | Grades 2 or 3 | Withhold
Colitis | Grade 4 | Permanently discontinue
Hepatitis with no tumor involvement of the liver | AST or ALT increases to more than 3 and up to 8 times ULN or Total bilirubin increases to more than 1.5 and up to 3 times ULN | Withhold
Hepatitis with no tumor involvement of the liver | AST or ALT increases to more than 8 times ULN or Total bilirubin increases to more than 3 times ULN | Permanently discontinue
Hepatitis with tumor involvement of the liver [If AST and ALT are less than or equal to ULN at baseline, withhold or permanently discontinue TECENTRIQ HYBREZA based on recommendations for hepatitis with no liver involvement] | Baseline AST or ALT is more than 1 and up to 3 times ULN and increases to more than 5 and up to 10 times ULN or Baseline AST or ALT is more than 3 and up to 5 times ULN and increases to more than 8 and up to 10 times ULN | Withhold
Hepatitis with tumor involvement of the liver [If AST and ALT are less than or equal to ULN at baseline, withhold or permanently discontinue TECENTRIQ HYBREZA based on recommendations for hepatitis with no liver involvement] | AST or ALT increases to more than 10 times ULN or Total bilirubin increases to more than 3 times ULN | Permanently discontinue
Endocrinopathies | Grades 3 or 4 | Withhold until clinically stable or permanently discontinue depending on severity
Nephritis with Renal Dysfunction | Grades 2 or 3 increased blood creatinine | Withhold
Nephritis with Renal Dysfunction | Grade 4 increased blood creatinine | Permanently discontinue
Exfoliative Dermatologic Conditions | Suspected SJS, TEN, or DRESS | Withhold
Exfoliative Dermatologic Conditions | Confirmed SJS, TEN, or DRESS | Permanently discontinue
Myocarditis or pericarditis | Grades 2, 3, or 4 | Permanently discontinue
Neurological Toxicities | Grade 2 | Withhold
Neurological Toxicities | Grades 3 or 4 | Permanently discontinue
Other Adverse Reactions
Infusion-Related Reactions [see Warnings and Precautions (5.2)] | Grades 1 or 2 | Pause or slow the rate of injection Premedication with antipyretic and antihistamines may be considered for subsequent doses.
Infusion-Related Reactions [see Warnings and Precautions (5.2)] | Grades 3 or 4 | Permanently discontinue
ALT = alanine aminotransferase, AST = aspartate aminotransferase, ULN = upper limit normal, DRESS = Drug Rash with Eosinophilia and Systemic Symptoms, SJS = Stevens Johnson syndrome, TEN = toxic epidermal necrolysis

2.5 Preparation Instructions

TECENTRIQ HYBREZA does not contain any antimicrobial preservative. If the TECENTRIQ HYBREZA dose is not administered immediately, refer to "Storage Instructions" [see Dosage and Administration (2.6)].

- Remove the vial from the refrigerator and allow the solution to acclimate to room temperature. Visually inspect for particulate matter and discoloration prior to administration. Discard the vial if the solution is cloudy, discolored, or visible particles are observed.
- Do not shake, freeze, or dilute.
- The unpunctured vial may be stored at room temperature in ambient light for a maximum of 4 hours prior to the preparation for administration.
- Use an 18-gauge transfer needle and syringe to withdraw the entire contents of the TECENTRIQ HYBREZA solution from the vial. Discard the vial and any residual drug remaining.
- TECENTRIQ HYBREZA is compatible with stainless steel transfer and injection needles, and polypropylene, polycarbonate, polyvinyl chloride, and polyurethane syringe material and subcutaneous administration sets.
- Remove the transfer needle from the syringe and replace it with a subcutaneous administration set (e.g. winged/butterfly) containing 23-gauge, 24-gauge, or 25-gauge hypodermic needle and with a priming volume that does not exceed 0.5 mL for administration.
- Prime the subcutaneous administration line with TECENTRIQ HYBREZA to eliminate the air in the line and stop when the fluid reaches the needle.
- Ensure the syringe contains exactly 15 mL of TECENTRIQ HYBREZA after priming the administration line by expelling any excess volume from the syringe.
- Administer immediately to avoid needle clogging.
- Discard any unused portion remaining.

2.6 Storage Instructions

- Do not store the prepared syringe that has been attached to the already-primed subcutaneous administration set.
- If the prepared syringe containing TECENTRIQ HYBREZA is not for immediate use, do not attach a subcutaneous administration set. The capped syringe may be stored at room temperature [at up to 25°C (77°F)] in ambient room lighting for up to 8 hours and in the refrigerator [2°C to 8°C (36°F to 46°F)] for up to 72 hours. Do not shake or freeze.
- If the prepared syringe is stored at 2°C to 8°C (36°F to 46°F), allow the syringe to acclimate to room temperature prior to administration.

3 DOSAGE FORMS AND STRENGTHS

Injection: 1,875 mg atezolizumab and 30,000 units hyaluronidase per 15 mL (125 mg and 2,000 units per mL) clear to slightly opalescent, and colorless to slightly yellow solution in a single-dose vial.

4 CONTRAINDICATIONS

TECENTRIQ HYBREZA is contraindicated in patients with known hypersensitivity to hyaluronidase or to any of its excipients.

5 WARNINGS AND PRECAUTIONS

5.1 Severe and Fatal Immune-Mediated Adverse Reactions

TECENTRIQ HYBREZA is a monoclonal antibody that belongs to a class of drugs that bind to either the programmed death-receptor 1 (PD-1) or the PD-ligand 1 (PD-L1), blocking the PD-1/PD-L1 pathway, thereby removing inhibition of the immune response, potentially breaking peripheral tolerance and inducing immune-mediated adverse reactions. Important immune-mediated adverse reactions listed under Warnings and Precautions may not include all possible severe and fatal immune-mediated reactions.

Immune-mediated adverse reactions, which may be severe or fatal, can occur in any organ system or tissue. Immune-mediated adverse reactions can occur at any time after starting a PD-1/PD-L1 blocking antibody. While immune-mediated adverse reactions usually manifest during treatment with PD-1/PD-L1 blocking antibodies, immune-mediated adverse reactions can also manifest after discontinuation of PD-1/PD-L1 blocking antibodies.

Early identification and management of immune-mediated adverse reactions are essential to ensure safe use of PD-1/PD-L1 blocking antibodies. Monitor patients closely for symptoms and signs that may be clinical manifestations of underlying immune-mediated adverse reactions. Evaluate liver enzymes, creatinine, and thyroid function at baseline and periodically during treatment. In cases of suspected immune-mediated adverse reactions, initiate appropriate workup to exclude alternative etiologies, including infection. Institute medical management promptly, including specialty consultation as appropriate.

Withhold or permanently discontinue TECENTRIQ HYBREZA depending on severity [see Dosage and Administration (2.3)]. In general, if TECENTRIQ HYBREZA requires interruption or discontinuation, administer systemic corticosteroid therapy (1 to 2 mg/kg/day prednisone or equivalent) until improvement to Grade 1 or less. Upon improvement to Grade 1 or less, initiate corticosteroid taper and continue to taper over at least 1 month. Consider administration of other systemic immunosuppressants in patients whose immune-mediated adverse reactions are not controlled with corticosteroid therapy.

Toxicity management guidelines for adverse reactions that do not necessarily require systemic steroids (e.g., endocrinopathies and dermatologic reactions) are discussed below.

Immune-Mediated Pneumonitis

TECENTRIQ HYBREZA can cause immune-mediated pneumonitis, including fatal adverse reactions. The incidence of pneumonitis is higher in patients who have received prior thoracic radiation.

Immune-mediated pneumonitis occurred in 2% (5/247) of patients with locally advanced or metastatic NSCLC receiving TECENTRIQ HYBREZA as monotherapy in the IMscin001 trial [see Adverse Reactions (6.1)], including Grade 2 (0.8%), and Grade 1 (1.2%) events. Pneumonitis led to the withholding of TECENTRIQ HYBREZA in one patient.

Systemic corticosteroids were required in 40% (2/5) patients with pneumonitis who received TECENTRIQ HYBREZA as monotherapy. Pneumonitis resolved in both patients. The single patient in whom TECENTRIQ HYBREZA was withheld for pneumonitis reinitiated TECENTRIQ HYBREZA after symptom improvement.

Intravenous Atezolizumab in Combination with Cobimetinib and Vemurafenib:

Immune-mediated pneumonitis occurred in 13% (29/230) of patients receiving intravenous atezolizumab in combination with cobimetinib and vemurafenib in the IMspire150 trial [see Adverse Reactions (6.1)], including Grade 3 (1.3%) and Grade 2 (7%) adverse reactions. Pneumonitis led to permanent discontinuation of intravenous atezolizumab in 2.6% of patients and withholding of intravenous atezolizumab in 7.4% of patients.

Systemic corticosteroids were required in 55% (16/29) of patients with pneumonitis. Pneumonitis resolved in 97% of the 29 patients. Of the 17 patients in whom intravenous atezolizumab was withheld for pneumonitis, 10 reinitiated intravenous atezolizumab after symptom improvement; of these, 50% had recurrence of pneumonitis.

Immune-Mediated Colitis

TECENTRIQ HYBREZA can cause immune-mediated colitis, including Grade 3 adverse reactions. Colitis can present with diarrhea, abdominal pain, and lower gastrointestinal bleeding. Cytomegalovirus (CMV) infection/reactivation has been reported in patients with corticosteroid-refractory immune-mediated colitis. In cases of corticosteroid-refractory colitis, consider repeating infectious workup to exclude alternative etiologies.

Immune-Mediated Hepatitis

TECENTRIQ HYBREZA can cause immune-mediated hepatitis, including fatal adverse reactions.

Immune-mediated hepatitis occurred in 1.2% (3/247) of patients with locally advanced or metastatic NSCLC receiving TECENTRIQ HYBREZA as monotherapy in the IMscin001 trial [see Adverse Reactions (6.1)], including Grade 1 (0.4%) and Grade 3 (0.8%) events. Hepatitis led to the withholding of TECENTRIQ HYBREZA in 0.4% of patients.

Systemic corticosteroids were required in 67% (2/3) of patients with hepatitis who received TECENTRIQ HYBREZA as monotherapy. Hepatitis resolved in 1 of the 3 patients.

Intravenous Atezolizumab in Combination with Cobimetinib and Vemurafenib:

Immune-mediated hepatitis occurred in 6.1% (14/230) of patients receiving intravenous atezolizumab in combination with cobimetinib and vemurafenib in the IMspire150 trial [see Adverse Reactions (6.1)], including Grade 4 (1.3%), Grade 3 (1.7%) and Grade 2 (1.3%) adverse reactions. Hepatitis led to permanent discontinuation of intravenous atezolizumab in 2.2% and withholding of intravenous atezolizumab in 1.7% of patients.

Systemic corticosteroids were required in 50% (7/14) of patients with hepatitis. Hepatitis resolved in 93% of the 14 patients. Of the 4 patients in whom intravenous atezolizumab was withheld for hepatitis, 3 reinitiated intravenous atezolizumab after symptom improvement; of these, 33% had recurrence of hepatitis.

Immune-Mediated Endocrinopathies

Adrenal Insufficiency:

TECENTRIQ HYBREZA can cause primary or secondary adrenal insufficiency, including Grade 3 adverse reactions. For Grade 2 or higher adrenal insufficiency, initiate symptomatic treatment, including hormone replacement as clinically indicated. Withhold or permanently discontinue TECENTRIQ HYBREZA depending on severity [see Dosage and Administration (2.3)].

Immune-mediated adrenal insufficiency occurred in 0.8% (2/247) of patients with locally advanced or metastatic NSCLC receiving TECENTRIQ HYBREZA as monotherapy in the IMscin001 trial [see Adverse Reactions (6.1)], including Grade 2 (0.4%) adverse reactions. Adrenal insufficiency led to the withholding of TECENTRIQ HYBREZA in both patients. Systemic corticosteroids were required in 50% (1/2) of patients with adrenal insufficiency who received TECENTRIQ HYBREZA as monotherapy; this single patient remained on systemic corticosteroids.

Hypophysitis:

TECENTRIQ HYBREZA can cause immune-mediated hypophysitis, including Grade 2 adverse reactions. Hypophysitis can present with acute symptoms associated with mass effect such as headache, photophobia, or visual field cuts. Hypophysitis can cause hypopituitarism. Initiate hormone replacement as clinically indicated. Withhold or permanently discontinue TECENTRIQ HYBREZA depending on severity [see Dosage and Administration (2.3)].

Immune-mediated hypophysitis occurred in 0.4% (1/247) of patients with locally advanced or metastatic NSCLC in the IMscin001 trial [see Adverse Reactions (6.1)] receiving TECENTRIQ HYBREZA as monotherapy, including Grade 1 (0.4%) adverse reactions. Hypophysitis led to the withholding of TECENTRIQ HYBREZA in this patient.

Thyroid Disorders:

TECENTRIQ HYBREZA can cause immune-mediated thyroid disorders. Thyroiditis can present with or without endocrinopathy. Hypothyroidism can follow hyperthyroidism. Initiate hormone replacement for hypothyroidism or medical management for hyperthyroidism as clinically indicated. Withhold or permanently discontinue TECENTRIQ HYBREZA depending on severity [see Dosage and Administration (2.3)].

Thyroiditis:

Immune-mediated thyroiditis occurred in 0.8% (2/247) of patients with locally advanced or metastatic NSCLC receiving TECENTRIQ HYBREZA as monotherapy in the IMscin001 trial [see Adverse Reactions (6.1)], including Grade 2 (0.4%) adverse reactions. Thyroiditis resolved in 50% of patients.

Hyperthyroidism:

Immune-mediated hyperthyroidism occurred in 2% (5/247) of patients with locally advanced or metastatic NSCLC receiving TECENTRIQ HYBREZA as monotherapy in the IMscin001 trial [see Adverse Reactions (6.1)], including Grade 2 (1.2%) adverse reactions. Hyperthyroidism led to withholding of TECENTRIQ HYBREZA in 0.8% of patients.

Anti-thyroid therapy was required in 40% (2/5) of patients with hyperthyroidism who received TECENTRIQ HYBREZA as monotherapy. Of these 2 patients, one remained on anti-thyroid treatment. Of the 2 patients in whom TECENTRIQ HYBREZA was withheld for hyperthyroidism, 1 patient reinitiated TECENTRIQ HYBREZA; this patient did not have recurrence of hyperthyroidism.

Intravenous Atezolizumab in Combination with Cobimetinib and Vemurafenib:

Hyperthyroidism occurred in 19% (43/230) of patients receiving intravenous atezolizumab in combination with cobimetinib and vemurafenib in the IMspire150 trial [see Adverse Reactions (6.1)], including Grade 3 (0.9%) and Grade 2 (7.8%) adverse reactions. Hyperthyroidism led to permanent discontinuation of intravenous atezolizumab in 0.4% and withholding of intravenous atezolizumab in 10% of patients. Antithyroid therapy was required in 53% (23/43) of patients with hyperthyroidism. Of these 23 patients, the majority remained on antithyroid treatment. Of the 24 patients in whom intravenous atezolizumab was withheld for hyperthyroidism, 18 patients reinitiated intravenous atezolizumab; of these, 28% had recurrence of hyperthyroidism.

Hypothyroidism:

TECENTRIQ HYBREZA can cause immune-mediated hypothyroidism, including Grade 4 adverse reactions. Immune-mediated hypothyroidism occurred in 10% (25/247) of patients with locally advanced or metastatic NSCLC who received TECENTRIQ HYBREZA as monotherapy in the IMscin001 trial [see Adverse Reactions (6.1)].

Hormone replacement was required in 68% (17/25) of patients with hypothyroidism who received TECENTRIQ HYBREZA as monotherapy. Two patients with hypothyroidism remained on thyroid hormone replacement.

Intravenous Atezolizumab in Combination with Platinum-based Chemotherapy:

Hypothyroidism occurred in 11% (277/2421) of patients with NSCLC (N = 2223) or SCLC (N = 198) enrolled in five randomized, active-controlled trials, including IMpower150, IMpower130 and IMpower133 receiving intravenous atezolizumab in combination with platinum-based chemotherapy, including Grade 4 (< 0.1%), Grade 3 (0.3%), and Grade 2 (5.7%) adverse reactions. Hypothyroidism led to permanent discontinuation of intravenous atezolizumab in 0.1% and withholding of intravenous atezolizumab in 1.6% of patients.

Hormone replacement therapy was required in 71% (198/277) of patients with hypothyroidism. The majority of patients with hypothyroidism remained on thyroid hormone replacement. Of the 39 patients in whom intravenous atezolizumab was withheld for hypothyroidism, 9 reinitiated intravenous atezolizumab after symptom improvement.

Intravenous Atezolizumab in Combination with Cobimetinib and Vemurafenib:

Hypothyroidism occurred in 26% (60/230) of patients receiving intravenous atezolizumab in combination with cobimetinib and vemurafenib in the IMspire150 trial [see Adverse Reactions (6.1)], including Grade 2 (9.1%) adverse reactions. Hypothyroidism led to withholding of intravenous atezolizumab in 2.6% of patients. Hormone replacement therapy was required in 52% (31/60) of patients with hypothyroidism. The majority of patients with hypothyroidism remained on thyroid hormone replacement. Of the 6 patients in whom intravenous atezolizumab was withheld for hypothyroidism, 4 reinitiated intravenous atezolizumab after symptom improvement. The majority of patients with hypothyroidism required long term thyroid replacement.

Type 1 Diabetes Mellitus, which can present with Diabetic Ketoacidosis:

TECENTRIQ HYBREZA can cause type 1 diabetes mellitus, including Grade 3 adverse reactions and diabetic ketoacidosis. Monitor patients for hyperglycemia or other signs and symptoms of diabetes. Initiate treatment with insulin as clinically indicated. Withhold or permanently discontinue TECENTRIQ HYBREZA depending on severity [see Dosage and Administration (2.3)].

Immune-Mediated Nephritis with Renal Dysfunction

TECENTRIQ HYBREZA can cause immune-mediated nephritis, including Grade 3 adverse reactions.

Intravenous Atezolizumab in Combination with Cobimetinib and Vemurafenib:

Immune-mediated nephritis with renal dysfunction occurred in 1.3% (3/230) of patients receiving intravenous atezolizumab in combination with cobimetinib and vemurafenib in the IMspire150 trial [see Adverse Reactions (6.1)], including Grade 2 (1.3%) adverse reactions. Nephritis led to permanent discontinuation of intravenous atezolizumab in 0.4% and withholding of intravenous atezolizumab in 0.9% of patients.

Systemic corticosteroids were required in 67% (2/3) of patients with nephritis. Nephritis resolved in all 3 of these patients. Of the 2 patients in whom intravenous atezolizumab was withheld for nephritis, both reinitiated intravenous atezolizumab after symptom improvement and neither had recurrence of nephritis.

Immune-Mediated Dermatologic Adverse Reactions

TECENTRIQ HYBREZA can cause immune-mediated rash or dermatitis, including Grade 3 and fatal adverse reactions. Exfoliative dermatitis, including Stevens-Johnson syndrome (SJS), drug reaction with eosinophilia and systemic symptoms (DRESS), and toxic epidermal necrolysis (TEN), has occurred with PD-1/PD-L1 blocking antibodies. Topical emollients and/or topical corticosteroids may be adequate to treat mild to moderate non-exfoliative rashes. Withhold or permanently discontinue TECENTRIQ HYBREZA depending on severity [see Dosage and Administration (2.3)].

One fatal case of an immune-mediated dermatologic adverse reaction, due to TEN, occurred (0.4%, 1/247) in patients with locally advanced or metastatic NSCLC receiving TECENTRIQ HYBREZA as monotherapy in the IMscin001 trial [see Adverse Reactions (6.1)].

Other Immune-Mediated Adverse Reactions

The following clinically significant immune-mediated adverse reactions occurred at an incidence of < 1% (unless otherwise noted) in patients receiving intravenous atezolizumab or were reported with the use of other PD-1/PD-L1 blocking antibodies. Severe or fatal cases have been reported for some of these adverse reactions.

- Cardiac/Vascular: Myocarditis, pericarditis, vasculitis.
- Nervous System: Meningitis, encephalitis, myelitis and demyelination, myasthenic syndrome/myasthenia gravis (including exacerbation), Guillain-Barré syndrome, nerve paresis, autoimmune neuropathy.
- Ocular: Uveitis, iritis, and other ocular inflammatory toxicities occurred. Some cases were associated with retinal detachment. Various grades of visual impairment, including blindness, occurred. If uveitis occurs in combination with other immune-mediated adverse reactions, consider a Vogt-Koyanagi-Harada-like syndrome, as this may require treatment with systemic steroids to reduce the risk of permanent vision loss.
- Gastrointestinal: Pancreatitis to include increases in serum amylase and lipase levels, gastritis, duodenitis.
- Musculoskeletal and Connective Tissue: Myositis/polymyositis, rhabdomyolysis and associated sequelae including renal failure, arthritis, polymyalgia rheumatic.
- Endocrine: Hypoparathyroidism.
- Other (Hematologic/Immune): Hemolytic anemia, aplastic anemia, hemophagocytic lymphohistiocytosis, systemic inflammatory response syndrome, histiocytic necrotizing lymphadenitis (Kikuchi lymphadenitis), sarcoidosis, immune thrombocytopenic purpura, solid organ transplant rejection, other transplant (including corneal graft) rejection.

5.2 Infusion-Related Reactions

TECENTRIQ HYBREZA can cause severe or life-threatening infusion-related reactions, including Grade 3 adverse reactions and anaphylaxis. Monitor for signs and symptoms of infusion-related reactions. Pause, slow the rate of, or permanently discontinue TECENTRIQ HYBREZA based on the severity [see Dosage and Administration (2.3)]. For Grade 1 or 2 infusion-related reactions, consider using pre-medications with subsequent doses.

5.3 Complications of Allogeneic HSCT after PD-1/PD-L1 Inhibitors

Fatal and other serious complications can occur in patients who receive allogeneic hematopoietic stem cell transplantation (HSCT) before or after being treated with a PD-1/PD-L1 blocking antibody. Transplant-related complications include hyperacute graft-versus-host disease (GVHD), acute GVHD, chronic GVHD, hepatic veno-occlusive disease after reduced intensity conditioning, and steroid-requiring febrile syndrome (without an identified infectious cause). These complications may occur despite intervening therapy between PD-1/PD-L1 blockage and allogeneic HSCT.

Follow patients closely for evidence of transplant-related complications and intervene promptly. Consider the benefits versus risks of treatment with a PD-1/PD-L1 blocking antibody prior to or after an allogeneic HSCT.

5.4 Embryo-Fetal Toxicity

Based on its mechanism of action, TECENTRIQ HYBREZA can cause fetal harm when administered to a pregnant woman. There are no available data on the use of TECENTRIQ HYBREZA in pregnant women. Animal studies have demonstrated that inhibition of the PD-L1/PD-1 pathway can lead to increased risk of immune-related rejection of the developing fetus resulting in fetal death.

Verify pregnancy status of females of reproductive potential prior to initiating TECENTRIQ HYBREZA. Advise females of reproductive potential of the potential risk to a fetus. Advise females of reproductive potential to use effective contraception during treatment with TECENTRIQ HYBREZA and for 5 months after the last dose [see Use in Specific Populations (8.1, 8.3)].

6 ADVERSE REACTIONS

The following clinically significant adverse reactions are described elsewhere in the labeling:

- Severe and Fatal Immune-Mediated Adverse Reactions [see Warnings and Precautions (5.1)]
- Infusion-Related Reactions [see Warnings and Precautions (5.2)]
- Complications of Allogeneic HSCT after PD-1/PD-L1 Inhibitors [see Warnings and Precautions (5.3)]

6.1 Clinical Trials Experience

Because clinical trials are conducted under widely varying conditions, adverse reaction rates observed in the clinical trials of a drug cannot be directly compared to rates in the clinical trials of another drug and may not reflect the rates observed in practice.

Adverse Reactions of TECENTRIQ HYBREZA in Adult Patients with NSCLC

The safety of TECENTRIQ HYBREZA was evaluated in IMscin001, open-label, multi-center, international, randomized trial for patients with locally advanced or metastatic NSCLC who have not been exposed to cancer immunotherapy and who have had disease progression on prior platinum-based therapy [see Clinical Studies (14.1)]. Patients with previously treated metastatic non-small cell lung cancer (NSCLC) either received TECENTRIQ HYBREZA (containing 1,875 mg of atezolizumab and 30,000 units of hyaluronidase) administered subcutaneously into the thigh over approximately 7 minutes every 3 weeks or intravenous atezolizumab every 3 weeks until disease progression or unacceptable toxicity. Among 247 patients who received TECENTRIQ HYBREZA, 32% were exposed for 6 months or longer and 8% were exposed for greater than one year.

The median age was 64 years (range: 27 to 85); 69% male; 67% White, 22% Asian, 0.8% Black or African American; 74% were non-Hispanic or Latino; 26% had an Eastern Cooperative Oncology Group (ECOG) performance status (PS) of 0, 74% had an ECOG PS of 1; and 70% of patients were current or previous smokers.

Serious adverse reactions occurred in 19% of patients who received TECENTRIQ HYBREZA. Serious adverse reactions (> 1%) included pneumonia, myocardial infarction, and pleural effusion. Fatal adverse reactions occurred in 6% of patients who received TECENTRIQ HYBREZA, including pneumonia (2.4%), myocardial infarction (1.2%), head injury (0.4%), ischemic stroke (0.4%), pleural effusion (0.4%), pulmonary embolism (0.4%), respiratory tract infection (0.4%), sepsis (0.4%), and toxic epidermal necrolysis (0.4%).

Permanent discontinuation of TECENTRIQ HYBREZA due to an adverse reaction occurred in 3.6% of patients. Adverse reactions which resulted in permanent discontinuation of TECENTRIQ HYBREZA in > 1% of patients included pneumonia (2%).

Dosage interruptions of TECENTRIQ HYBREZA due to an adverse reaction occurred in 32% of patients. Adverse reactions which required dosage interruption in > 1% of patients were COVID-19 (4.9%), increased aspartate aminotransferase (2.8%), increased alanine aminotransferase (2.4%), pneumonia (2.4%), anemia (1.6%), dyspnea (1.6%), fatigue (1.2%), and viral respiratory tract infection (1.2%). The most common adverse reactions of any grade (occurring in ≥ 10% of patients) were fatigue (19%), musculoskeletal pain (15%), cough (13%), dyspnea (12%), and decreased appetite (11%).

Tables 3 and 4 summarize adverse reactions and selected laboratory abnormalities, respectively in TECENTRIQ HYBREZA-treated patients in IMscin001.

Table 3: Adverse Reactions (≥ 10%) in Adult Patients with Locally Advanced or Metastatic NSCLC Who Received TECENTRIQ HYBREZA in IMscin001
Adverse Reaction [Graded per NCI CTCAE v5.0] | TECENTRIQ HYBREZA n = 247 |  | Intravenous Atezolizumab n = 124
Adverse Reaction [Graded per NCI CTCAE v5.0] | All Grades (%) | Grades 3–4 (%) | All Grades (%) | Grades 3–4 (%)
General Disorder and Administration Site Conditions
Fatigue [Composite term includes fatigue, asthenia] | 19 | 0.8 | 18 | 0
Musculoskeletal and Connective Tissue disorders
Musculoskeletal Pain [Composite term includes back pain, myalgia, bone pain, musculoskeletal chest pain, neck pain, spinal pain, non-cardiac chest pain] | 15 | 0.4 | 13 | 3.2
Respiratory, Thoracic and Mediastinal
Cough [Composite term includes cough, productive cough] | 13 | 0 | 7 | 0
Dyspnea [Composite term includes dyspnea, dyspnea at rest, dyspnea exertional] | 12 | 1.2 | 15 | 1.6
Metabolism and Nutrition Disorders
Decreased appetite | 11 | 0 | 11 | 0

Clinically relevant adverse reactions in < 10% of patients who received TECENTRIQ HYBREZA were local injection site reactions (4.5%) and pyrexia (1.2%).

Table 4: Select Laboratory Abnormalities (≥ 20%) That Worsened from Baseline in Adult Patients with Advanced or Metastatic NSCLC Who Received TECENTRIQ HYBREZA in IMscin001
Laboratory Abnormality [Graded per NCI CTCAE v5.0] | TECENTRIQ HYBREZA (n = 247) |  | Intravenous Atezolizumab (n = 124)
Laboratory Abnormality [Graded per NCI CTCAE v5.0] | All Grades (%) | Grades 3–4 (%) | All Grades (%) | Grades 3–4 (%)
Hematology
Decreased Hemoglobin | 67 | 6 | 63 | 5
Decreased lymphocytes | 37 | 9 | 45 | 15
Chemistry
Decreased Sodium | 46 | 3.9 | 47 | 5
Decreased Albumin | 34 | 2.2 | 27 | 0
Increased Alkaline Phosphatase | 33 | 1.3 | 27 | 0
Increased AST | 28 | 2.6 | 32 | 2.6
Increased ALT | 28 | 2.6 | 23 | 1.7
Decreased calcium | 22 | 2.6 | 23 | 0.9
Increased calcium | 20 | 2.6 | 24 | 1.7
Increased potassium | 21 | 1.7 | 22 | 1.7
Increased INR | 20 | 2 | 23 | 0
Increased Creatinine | 19 | 1.7 | 26 | 0.9
Each test incidence is based on the number of patients who had both baseline and at least one on-study laboratory measurement available: TECENTRIQ HYBREZA (48-233) and intravenous atezolizumab (19-117)

Adverse Reactions in Adult Patients with NSCLC Treated with Intravenous Atezolizumab

The safety of TECENTRIQ HYBREZA for its approved NSCLC indications [see Indications and Usage (1.1)] has been established in adequate and well-controlled studies of intravenous atezolizumab for the:

- adjuvant treatment (following tumor resection and platinum-based chemotherapy) in adult patients with stage II to IIIA NSCLC whose tumors have PD-L1 expression on ≥ 1% of tumor cells (IMpower010 study).
- first-line treatment of adult patients with metastatic NSCLC whose tumors have high PD-L1 expression (PD-L1 stained ≥ 50% of tumor cells [TC ≥ 50%] or PD-L1 stained tumor-infiltrating immune cells [IC] covering ≥ 10% of the tumor area [IC ≥ 10%]), with no EGFR or ALK genomic tumor aberrations (IMpower110 study).
- first-line treatment of adult patients with metastatic non-squamous NSCLC with no EGFR or ALK genomic tumor aberrations (IMpower150 study).
- first-line treatment of adult patients with metastatic non-squamous NSCLC with no EGFR or ALK genomic tumor aberrations (IMpower130 study).
- first-line treatment of adult patients with metastatic NSCLC whose tumors have high PD-L1 expression, with no EGFR or ALK genomic tumor aberrations (OAK study).

Below is a description of adverse reactions of intravenous atezolizumab in these adequate and well-controlled NSCLC studies.

Non-Small Cell Lung Cancer (NSCLC)

Adjuvant Treatment of Early-stage NSCLC

IMpower010

The safety of intravenous atezolizumab was evaluated in IMpower010, a multicenter, open-label, randomized trial for the adjuvant treatment of patients with stage IB (tumors ≥ 4 cm) -IIIA NSCLC who had complete tumor resection and received up to 4 cycles of cisplatin-based adjuvant chemotherapy. Patients received intravenous atezolizumab 1200 mg every 3 weeks (n = 495) for 1 year (16 cycles), unless disease progression or unacceptable toxicity occurred, or best supportive care [see Clinical Studies (14.1)]. The median number of cycles received was 16 (range: 1, 16).

Fatal adverse reactions occurred in 1.8% of patients receiving intravenous atezolizumab; these included multiple organ dysfunction syndrome, pneumothorax, interstitial lung disease, arrhythmia, acute cardiac failure, myocarditis, cerebrovascular accident, death of unknown cause, and acute myeloid leukemia (1 patient each).

Serious adverse reactions occurred in 18% of patients receiving intravenous atezolizumab. The most frequent serious adverse reactions (> 1%) were pneumonia (1.8%), pneumonitis (1.6%), and pyrexia (1.2%).

Intravenous atezolizumab was discontinued due to adverse reactions in 18% of patients; the most common adverse reactions (≥ 1%) leading to intravenous atezolizumab discontinuation were pneumonitis (2.2%), hypothyroidism (1.6%), increased aspartate aminotransferase (1.4%), arthralgia (1.0%), and increased alanine aminotransferase (1.0%).

Adverse reactions leading to interruption of intravenous atezolizumab occurred in 29% of patients; the most common (> 1%) were rash (3.0%), hyperthyroidism (2.8%), hypothyroidism (1.6%), increased AST (1.6%), pyrexia (1.6%), increased ALT (1.4%), upper respiratory tract infection (1.4%), headache (1.2%), peripheral neuropathy (1.2%), and pneumonia (1.2%).

Tables 5 and 6 summarize adverse reactions and selected laboratory abnormalities in patients receiving intravenous atezolizumab in IMpower010.

Table 5: Adverse Reactions Occurring in ≥ 10% of Patients with Early-Stage NSCLC Receiving Intravenous Atezolizumab in IMpower010
Adverse Reaction [Graded per NCI CTCAE v4.0] | Intravenous Atezolizumab N = 495 |  | Best Supportive Care N = 495
Adverse Reaction [Graded per NCI CTCAE v4.0] | All Grades (%) | Grades 3–4 (%) | All Grades (%) | Grades 3–4 (%)
Skin and Subcutaneous Tissue
Rash [Includes rash, dermatitis, genital rash, skin exfoliation, rash maculo-papular, rash erythematous, rash papular, lichen planus, eczema asteatotic, dermatitis exfoliative, palmar-plantar erythrodysaesthesia syndrome, dyshidrotic eczema, eczema, drug eruption, rash pruritic, toxic skin eruption, dermatitis acneiform] | 17 | 1.2 | 1.4 | 0
Pruritus | 10 | 0 | 0.6 | 0
Endocrine Disorders
Hypothyroidism [Includes hypothyroidism, autoimmune hypothyroidism, primary hypothyroidism, blood thyroid stimulating hormone increased] | 14 | 0 | 0.6 | 0
Respiratory, Thoracic and Mediastinal
Cough [Productive cough, upper airway cough syndrome, cough] | 16 | 0 | 11 | 0
General
Pyrexia [Includes pyrexia, body temperature increased, hyperthermia] | 14 | 0.8 | 2.2 | 0.2
Fatigue [Includes fatigue, asthenia] | 14 | 0.6 | 5 | 0.2
Nervous System Disorders
Peripheral neuropathy [Includes paraesthesia, neuropathy peripheral, peripheral sensory neuropathy, hypoaesthesia, polyneuropathy, dysaesthesia, neuralgia, axonal neuropathy] | 12 | 0.4 | 7 | 0.2
Musculoskeletal and Connective Tissue
Musculoskeletal pain [Includes myalgia, bone pain, back pain, spinal pain, musculoskeletal chest pain, pain in extremity, neck pain, non-cardiac chest pain, musculoskeletal discomfort, musculoskeletal stiffness, musculoskeletal pain] | 14 | 0.8 | 9 | 0.2
Arthralgia [Includes arthralgia, arthritis] | 11 | 0.6 | 6 | 0

Table 6: Laboratory Abnormalities Worsening from Baseline Occurring in ≥ 20% of Patients with Early-Stage NSCLC Receiving Intravenous Atezolizumab in IMpower010
Laboratory Abnormality [Graded per NCI CTCAE v4.0, except for increased creatinine which only includes patients with creatinine increase based on upper limit of normal definition for Grade 1 events (NCI CTCAE v5.0).] | Intravenous Atezolizumab [The denominators used to calculate the rate varied from 78–480 for BSC arm and 483 for intravenous atezolizumab are for all tests of interest based on the number of patients with a baseline value and at least one post-treatment value.] |  | Best Supportive Care
Laboratory Abnormality [Graded per NCI CTCAE v4.0, except for increased creatinine which only includes patients with creatinine increase based on upper limit of normal definition for Grade 1 events (NCI CTCAE v5.0).] | All Grades (%) | Grades 3–4 (%) | All Grades (%) | Grades 3–4 (%)
Chemistry
Increased aspartate aminotransferase | 34 | 2.5 | 18 | 0
Increased alanine aminotransferase | 30 | 3.3 | 19 | 0.4
Hyperkalemia | 24 | 3.5 | 15 | 2.5
Increased blood creatinine | 31 | 0.2 | 23 | 0.2

Metastatic Chemotherapy-Naïve NSCLC

IMpower110

The safety of intravenous atezolizumab was evaluated in IMpower110, a multicenter, international, randomized, open-label study in 549 chemotherapy-naïve patients with stage IV NSCLC, including those with EGFR or ALK genomic tumor aberrations. Patients received intravenous atezolizumab 1200 mg every 3 weeks (n = 286) or platinum-based chemotherapy consisting of carboplatin or cisplatin with either pemetrexed or gemcitabine (n = 263) until disease progression or unacceptable toxicity [see Clinical Studies (14.1)]. IMpower110 enrolled patients whose tumors express PD-L1 (PD-L1 stained ≥ 1% of tumor cells [TC] or PD-L1 stained tumor-infiltrating immune cells [IC] covering ≥ 1% of the tumor area). The median duration of exposure to intravenous atezolizumab was 5.3 months (0 to 33 months).

Fatal adverse reactions occurred in 3.8% of patients receiving intravenous atezolizumab; these included death (reported as unexplained death and death of unknown cause), aspiration, chronic obstructive pulmonary disease, pulmonary embolism, acute myocardial infarction, cardiac arrest, mechanical ileus, sepsis, cerebral infarction, and device occlusion (1 patient each).

Serious adverse reactions occurred in 28% of patients receiving intravenous atezolizumab. The most frequent serious adverse reactions (> 2%) were pneumonia (2.8%), chronic obstructive pulmonary disease (2.1%) and pneumonitis (2.1%).

Intravenous atezolizumab was discontinued due to adverse reactions in 6% of patients; the most common adverse reactions (≥ 2 patients) leading to intravenous atezolizumab discontinuation were peripheral neuropathy and pneumonitis.

Adverse reactions leading to interruption of intravenous atezolizumab occurred in 26% of patients; the most common (> 1%) were ALT increased (2.1%), AST increased (2.1%), pneumonitis (2.1%), pyrexia (1.4%), pneumonia (1.4%) and upper respiratory tract infection (1.4%).

Tables 7 and 8 summarize adverse reactions and selected laboratory abnormalities in patients receiving intravenous atezolizumab in IMpower110.

Table 7: Adverse Reactions Occurring in ≥ 10% of Patients with NSCLC Receiving Intravenous Atezolizumab in IMpower110
Adverse Reaction | Intravenous Atezolizumab N = 286 |  | Platinum-Based Chemotherapy N = 263
Adverse Reaction | All Grades (%) | Grades 3–4 (%) | All Grades (%) | Grades 3–4 (%)
Gastrointestinal
Nausea | 14 | 0.3 | 34 | 1.9
Constipation | 12 | 1.0 | 22 | 0.8
Diarrhea | 11 | 0 | 12 | 0.8
General
Fatigue/Asthenia | 25 | 1.4 | 34 | 4.2
Pyrexia | 14 | 0 | 9 | 0.4
Metabolism and Nutrition
Decreased appetite | 15 | 0.7 | 19 | 0
Respiratory, Thoracic and Mediastinal
Dyspnea | 14 | 0.7 | 10 | 0
Cough | 12 | 0.3 | 10 | 0
Graded per NCI CTCAE v4.0

Table 8: Laboratory Abnormalities Worsening from Baseline Occurring in ≥ 20% of Patients Receiving Intravenous Atezolizumab in IMpower110
Laboratory Abnormality | Intravenous Atezolizumab |  | Platinum-Based Chemotherapy
Laboratory Abnormality | All Grades (%) | Grades 3–4 (%) | All Grades (%) | Grades 3–4 (%)
Hematology
Anemia | 69 | 1.8 | 94 | 20
Lymphopenia | 47 | 9 | 59 | 17
Chemistry
Hypoalbuminemia | 48 | 0.4 | 39 | 2
Increased alkaline phosphatase | 46 | 2.5 | 42 | 1.2
Hyponatremia | 44 | 9 | 36 | 7
Increased ALT | 38 | 3.2 | 32 | 0.8
Increased AST | 36 | 3.2 | 32 | 0.8
Hyperkalemia | 29 | 3.9 | 36 | 2.7
Hypocalcemia | 24 | 1.4 | 24 | 2.7
Increased blood creatinine | 24 | 0.7 | 33 | 1.5
Hypophosphatemia | 23 | 3.6 | 21 | 2
Each test incidence is based on the number of patients who had at least one on-study laboratory measurement available: intravenous atezolizumab (range: 278–281); platinum-based chemotherapy (range: 256–260). Graded per NCI CTCAE v4.0. Increased blood creatinine only includes patients with test results above the normal range.

First-Line Metastatic Non-squamous NSCLC

IMpower150

The safety of intravenous atezolizumab with bevacizumab, paclitaxel and carboplatin was evaluated in IMpower150, a multicenter, international, randomized, open-label trial in which 393 chemotherapy-naïve patients with metastatic non-squamous NSCLC received intravenous atezolizumab 1200 mg with bevacizumab 15 mg/kg, paclitaxel 175 mg/m^2 or 200 mg/m^2, and carboplatin AUC 6 mg/mL/min intravenously every 3 weeks for a maximum of 4 or 6 cycles, followed by intravenous atezolizumab 1200 mg with bevacizumab 15 mg/kg intravenously every 3 weeks until disease progression or unacceptable toxicity [see Clinical Studies (14.1)]. The median duration of exposure to intravenous atezolizumab was 8.3 months in patients receiving intravenous atezolizumab with bevacizumab, paclitaxel, and carboplatin.

Fatal adverse reactions occurred in 6% of patients receiving intravenous atezolizumab; these included hemoptysis, febrile neutropenia, pulmonary embolism, pulmonary hemorrhage, death, cardiac arrest, cerebrovascular accident, pneumonia, aspiration pneumonia, chronic obstructive pulmonary disease, intracranial hemorrhage, intestinal angina, intestinal ischemia, intestinal obstruction and aortic dissection.

Serious adverse reactions occurred in 44%. The most frequent serious adverse reactions (> 2%) were febrile neutropenia, pneumonia, diarrhea, and hemoptysis.

Intravenous atezolizumab was discontinued due to adverse reactions in 15% of patients; the most common adverse reaction leading to discontinuation was pneumonitis (1.8%).

Adverse reactions leading to interruption of intravenous atezolizumab occurred in 48%; the most common (> 1%) were neutropenia, thrombocytopenia, fatigue/asthenia, diarrhea, hypothyroidism, anemia, pneumonia, pyrexia, hyperthyroidism, febrile neutropenia, increased ALT, dyspnea, dehydration and proteinuria.

Tables 9 and 10 summarize adverse reactions and laboratory abnormalities in patients receiving intravenous atezolizumab with bevacizumab, paclitaxel, and carboplatin in IMpower150.

Table 9: Adverse Reactions Occurring in ≥ 15% of Patients with NSCLC Receiving Intravenous Atezolizumab in IMpower150
Adverse Reaction | Intravenous Atezolizumab with Bevacizumab, Paclitaxel, and Carboplatin N = 393 |  | Bevacizumab, Paclitaxel and Carboplatin N = 394
Adverse Reaction | All Grades (%) | Grades 3–4 (%) | All Grades (%) | Grades 3–4 (%)
Nervous System
Neuropathy [Includes neuropathy peripheral, peripheral sensory neuropathy, hypoesthesia, paresthesia, dysesthesia, polyneuropathy] | 56 | 3 | 47 | 3
Headache | 16 | 0.8 | 13 | 0
General
Fatigue/Asthenia | 50 | 6 | 46 | 6
Pyrexia | 19 | 0.3 | 9 | 0.5
Skin and Subcutaneous Tissue
Alopecia | 48 | 0 | 46 | 0
Rash [Includes rash, rash maculo-papular, drug eruption, eczema, eczema asteatotic, dermatitis, contact dermatitis, rash erythematous, rash macular, pruritic rash, seborrheic dermatitis, dermatitis psoriasiform] | 23 | 2 | 10 | 0.3
Musculoskeletal and Connective Tissue
Myalgia/Pain [Includes pain in extremity, musculoskeletal chest pain, musculoskeletal discomfort, neck pain, back pain, myalgia, and bone pain] | 42 | 3 | 34 | 2
Arthralgia | 26 | 1 | 22 | 1
Gastrointestinal
Nausea | 39 | 4 | 32 | 2
Diarrhea [Includes diarrhea, gastroenteritis, colitis, enterocolitis] | 33 | 6 | 25 | 0.5
Constipation | 30 | 0.3 | 23 | 0.3
Vomiting | 19 | 2 | 18 | 1
Metabolism and Nutrition
Decreased appetite | 29 | 4 | 21 | 0.8
Vascular
Hypertension | 25 | 9 | 22 | 8
Respiratory
Cough | 20 | 0.8 | 19 | 0.3
Epistaxis | 17 | 1 | 22 | 0.3
Renal
Proteinuria [Based on adverse reaction terms since laboratory data for proteinuria was not systematically collected] | 16 | 3 | 15 | 3
Graded per NCI CTCAE v4.0

Table 10: Laboratory Abnormalities Worsening from Baseline Occurring in ≥ 20% of Patients with NSCLC Receiving Intravenous Atezolizumab in IMpower150
Laboratory Abnormality | Intravenous Atezolizumab with Bevacizumab, Paclitaxel, and Carboplatin |  | Bevacizumab, Paclitaxel and Carboplatin
Laboratory Abnormality | All Grades (%) | Grades 3–4 (%) | All Grades (%) | Grades 3–4 (%)
Hematology
Anemia | 83 | 10 | 83 | 9
Neutropenia | 52 | 31 | 45 | 26
Lymphopenia | 48 | 17 | 38 | 13
Chemistry
Hyperglycemia | 61 | 0 | 60 | 0
Increased BUN | 52 | NA [NA = Not applicable. NCI CTCAE does not provide a Grades 3–4 definition for these laboratory abnormalities] | 44 | NA
Hypomagnesemia | 42 | 2 | 36 | 1
Hypoalbuminemia | 40 | 3 | 31 | 2
Increased AST | 40 | 4 | 28 | 0.8
Hyponatremia | 38 | 10 | 36 | 9
Increased Alkaline Phosphatase | 37 | 2 | 32 | 1
Increased ALT | 37 | 6 | 28 | 0.5
Increased TSH | 30 | NA | 20 | NA
Hyperkalemia | 28 | 3 | 25 | 2
Increased Creatinine | 28 | 1 | 19 | 2
Hypocalcemia | 26 | 3 | 21 | 3
Hypophosphatemia | 25 | 4 | 18 | 4
Hypokalemia | 23 | 7 | 14 | 4
Hyperphosphatemia | 25 | NA | 19 | NA
Each test incidence is based on the number of patients who had both baseline and at least one on-study laboratory measurement available: Intravenous Atezolizumab with bevacizumab, paclitaxel, and carboplatin range: (337–380); bevacizumab, paclitaxel, and carboplatin (range: 337–382). Graded per NCI CTCAE v4.0

IMpower130

The safety of intravenous atezolizumab with paclitaxel protein-bound and carboplatin was evaluated in IMpower130, a multicenter, international, randomized, open-label trial in which 473 chemotherapy-naïve patients with metastatic non-squamous NSCLC received intravenous atezolizumab 1200 mg and carboplatin AUC 6 mg/mL/min intravenously on Day 1 and paclitaxel protein-bound 100 mg/m^2 intravenously on Days 1, 8, and 15 of each 21-day cycle for a maximum of 4 or 6 cycles, followed by intravenous atezolizumab 1200 mg intravenously every 3 weeks until disease progression or unacceptable toxicity [see Clinical Studies (14.1)]. Among patients receiving intravenous atezolizumab, 55% were exposed for 6 months or longer and 3.5% were exposed for greater than one year.

Fatal adverse reactions occurred in 5.3% of patients receiving intravenous atezolizumab; these included pneumonia (1.1%), pulmonary embolism (0.8%), myocardial infarction (0.6%), cardiac arrest (0.4%), pneumonitis (0.4%) and sepsis, septic shock, staphylococcal sepsis, aspiration, respiratory distress, cardiorespiratory arrest, ventricular tachycardia, death (not otherwise specified), and hepatic cirrhosis (0.2% each).

Serious adverse reactions occurred in 51% of patients receiving intravenous atezolizumab. The most frequent serious adverse reactions (≥ 2%) were pneumonia (6%), diarrhea (3%), lung infection (3%), pulmonary embolism (3%), chronic obstructive pulmonary disease exacerbation (2.5%), dyspnea (2.3%), and febrile neutropenia (1.9%).

Intravenous atezolizumab was discontinued due to adverse reactions in 13% of patients; the most common adverse reactions leading to discontinuation were pneumonia (0.8%), pulmonary embolism (0.8%), fatigue (0.6%), dyspnea (0.6%), pneumonitis (0.6%), neutropenia (0.4%), nausea (0.4%), renal failure (0.4%), cardiac arrest (0.4%), and septic shock (0.4%).

Adverse reactions leading to interruption of intravenous atezolizumab occurred in 62% of patients; the most common (> 1%) were neutropenia, thrombocytopenia, anemia, diarrhea, fatigue/asthenia, pneumonia, dyspnea, pneumonitis, pyrexia, nausea, acute kidney injury, vomiting, pulmonary embolism, arthralgia, infusion-related reaction, abdominal pain, chronic obstructive pulmonary disease exacerbation, dehydration, and hypokalemia.

Tables 11 and 12 summarize adverse reactions and laboratory abnormalities in patients receiving intravenous atezolizumab with paclitaxel protein-bound and carboplatin in IMpower130.

Table 11: Adverse Reactions Occurring in ≥ 20% of Patients with NSCLC Receiving Intravenous Atezolizumab in IMpower130
Adverse Reaction | Intravenous Atezolizumab with Paclitaxel Protein-Bound and Carboplatin N = 473 |  | Paclitaxel Protein-Bound and Carboplatin N = 232
Adverse Reaction | All Grades (%) | Grades 3–4 (%) | All Grades (%) | Grades 3–4 (%)
General
Fatigue/Asthenia | 61 | 11 | 60 | 8
Gastrointestinal
Nausea | 50 | 3.4 | 46 | 2.2
Diarrhea [Includes diarrhea, colitis, and gastroenteritis] | 43 | 6 | 32 | 6
Constipation | 36 | 1.1 | 31 | 0
Vomiting | 27 | 2.7 | 19 | 2.2
Musculoskeletal and Connective Tissue
Myalgia/Pain [Includes back pain, pain in extremity, myalgia, musculoskeletal chest pain, bone pain, neck pain and musculoskeletal discomfort] | 38 | 3 | 22 | 0.4
Nervous System
Neuropathy [Includes neuropathy peripheral, peripheral sensory neuropathy, hypoesthesia, paresthesia, dysesthesia, polyneuropathy] | 33 | 2.5 | 28 | 2.2
Respiratory, Thoracic and Mediastinal
Dyspnea [Includes dyspnea, dyspnea exertional and wheezing] | 32 | 4.9 | 25 | 1.3
Cough | 27 | 0.6 | 17 | 0
Skin and Subcutaneous Tissue
Alopecia | 32 | 0 | 27 | 0
Rash [Includes rash, rash maculo-papular, eczema, rash pruritic, rash erythematous, dermatitis, dermatitis contact, drug eruption, seborrheic dermatitis and rash macular] | 20 | 0.6 | 11 | 0.9
Metabolism and Nutrition
Decreased appetite | 30 | 2.1 | 26 | 2.2
Graded per NCI CTCAE v4.0

Table 12: Laboratory Abnormalities Worsening from Baseline Occurring in ≥ 20% of Patients Receiving Intravenous Atezolizumab in IMpower130
Laboratory Abnormality | Intravenous Atezolizumab with Paclitaxel Protein-Bound and Carboplatin N = 473 |  | Paclitaxel Protein-Bound and Carboplatin N = 232
Laboratory Abnormality | All Grades (%) | Grades 3–4 (%) | All Grades (%) | Grades 3–4 (%)
Hematology
Anemia | 92 | 33 | 87 | 25
Neutropenia | 75 | 50 | 67 | 39
Thrombocytopenia | 73 | 19 | 59 | 13
Lymphopenia | 71 | 23 | 61 | 16
Chemistry
Hyperglycemia | 75 | 8 | 66 | 8
Hypomagnesemia | 50 | 3.4 | 42 | 3.2
Hyponatremia | 37 | 9 | 28 | 7
Hypoalbuminemia | 35 | 1.3 | 31 | 0
Increased ALT | 31 | 2.8 | 24 | 3.9
Hypocalcemia | 31 | 2.6 | 27 | 1.8
Hypophosphatemia | 29 | 6 | 20 | 3.2
Increased AST | 28 | 2.2 | 24 | 1.8
Increased TSH | 26 | NA [NA = Not applicable. NCI CTCAE does not provide a Grades 3–4 definition for these laboratory abnormalities] | 5 | NA
Hypokalemia | 26 | 6 | 24 | 4.4
Increased Alkaline Phosphatase | 25 | 2.6 | 22 | 1.3
Increased Blood Creatinine | 23 | 2.8 | 16 | 0.4
Hyperphosphatemia | 21 | NA | 13 | NA
Each test incidence is based on the number of patients who had both baseline and at least one on-study laboratory measurement available: intravenous atezolizumab with paclitaxel protein-bound and carboplatin (range: 423–467); paclitaxel protein-bound and carboplatin (range: 218–229). Graded per NCI CTCAE v4.0.

Previously Treated Metastatic NSCLC

OAK

The safety of intravenous atezolizumab was evaluated in OAK, a multicenter, international, randomized, open-label trial in patients with metastatic NSCLC who progressed during or following a platinum-containing regimen, regardless of PD-L1 expression [see Clinical Studies (14.1)]. A total of 609 patients received intravenous atezolizumab 1200 mg intravenously every 3 weeks until unacceptable toxicity, radiographic progression, or clinical progression or docetaxel (n = 578) 75 mg/m^2 intravenously every 3 weeks until unacceptable toxicity or disease progression. The study excluded patients with active or prior autoimmune disease or with medical conditions that required systemic corticosteroids. The median duration of exposure was 3.4 months (0 to 26 months) in intravenous atezolizumab-treated patients and 2.1 months (0 to 23 months) in docetaxel-treated patients.

The study population characteristics were: median age of 63 years (25 to 85 years), 46% age 65 years or older, 62% male, 71% White, 20% Asian, 68% former smoker, 16% current smoker, and 63% had Eastern Cooperative Oncology Group (ECOG) performance status of 1.

Fatal adverse reactions occurred in 1.6% of patients; these included pneumonia, sepsis, septic shock, dyspnea, pulmonary hemorrhage, sudden death, myocardial ischemia or renal failure.

Serious adverse reactions occurred in 33.5% of patients. The most frequent serious adverse reactions (> 1%) were pneumonia, sepsis, dyspnea, pleural effusion, pulmonary embolism, pyrexia and respiratory tract infection.

Intravenous atezolizumab was discontinued due to adverse reactions in 8% of patients. The most common adverse reactions leading to intravenous atezolizumab discontinuation were fatigue, infections and dyspnea. Adverse reactions leading to interruption of intravenous atezolizumab occurred in 25% of patients; the most common (> 1%) were pneumonia, liver function test abnormality, dyspnea, fatigue, pyrexia, and back pain.

Tables 13 and 14 summarize adverse reactions and laboratory abnormalities, respectively, in OAK.

Table 13: Adverse Reactions Occurring in ≥ 10% of Patients with NSCLC Receiving Intravenous Atezolizumab in OAK
Adverse Reaction | Intravenous Atezolizumab N = 609 |  | Docetaxel N = 578
Adverse Reaction | All Grades (%) | Grades 3–4 (%) | All Grades (%) | Grades 3–4 (%)
General
Fatigue/Asthenia [Includes fatigue and asthenia] | 44 | 4 | 53 | 6
Pyrexia | 18 | < 1 | 13 | < 1
Respiratory
Cough [Includes cough and exertional cough] | 26 | < 1 | 21 | < 1
Dyspnea | 22 | 2.8 | 21 | 2.6
Metabolism and Nutrition
Decreased appetite | 23 | < 1 | 24 | 1.6
Musculoskeletal
Myalgia/Pain [Includes musculoskeletal pain, musculoskeletal stiffness, musculoskeletal chest pain, myalgia] | 20 | 1.3 | 20 | < 1
Arthralgia | 12 | 0.5 | 10 | 0.2
Gastrointestinal
Nausea | 18 | < 1 | 23 | < 1
Constipation | 18 | < 1 | 14 | < 1
Diarrhea | 16 | < 1 | 24 | 2
Skin
Rash [Includes rash, erythematous rash, generalized rash, maculopapular rash, papular rash, pruritic rash, pustular rash, pemphigoid] | 12 | < 1 | 10 | 0
Graded per NCI CTCAE v4.0

Table 14: Laboratory Abnormalities Worsening from Baseline Occurring in ≥ 20% of Patients with NSCLC Receiving Intravenous Atezolizumab in OAK
Laboratory Abnormality | Intravenous Atezolizumab |  | Docetaxel
Laboratory Abnormality | All Grades (%) | Grades 3–4 (%) | All Grades (%) | Grades 3–4 (%)
Hematology
Anemia | 67 | 3 | 82 | 7
Lymphocytopenia | 49 | 14 | 60 | 21
Chemistry
Hypoalbuminemia | 48 | 4 | 50 | 3
Hyponatremia | 42 | 7 | 31 | 6
Increased Alkaline Phosphatase | 39 | 2 | 25 | 1
Increased AST | 31 | 3 | 16 | 0.5
Increased ALT | 27 | 3 | 14 | 0.5
Hypophosphatemia | 27 | 5 | 23 | 4
Hypomagnesemia | 26 | 1 | 21 | 1
Increased Creatinine | 23 | 2 | 16 | 1
Each test incidence is based on the number of patients who had both baseline and at least one on-study laboratory measurement available: intravenous atezolizumab (range: 546–585) and docetaxel (range: 532–560). Graded according to NCI CTCAE version 4.0

Adverse Reactions in Adult Patients with Small Cell Lung Cancer

The safety of TECENTRIQ HYBREZA for its approved Small Cell Lung Cancer (SCLC) indications [see Indications and Usage (1.2)] has been established in adequate and well-controlled studies of intravenous atezolizumab for SCLC (IMpower133 and IMforte studies).

Small Cell Lung Cancer (SCLC)

IMpower133

The safety of intravenous atezolizumab with carboplatin and etoposide was evaluated in IMpower133, a randomized, multicenter, double-blind, placebo-controlled trial in which 198 patients with ES-SCLC received intravenous atezolizumab 1200 mg and carboplatin AUC 5 mg/mL/min on Day 1 and etoposide 100 mg/m^2 intravenously on Days 1, 2 and 3 of each 21-day cycle for a maximum of 4 cycles, followed by intravenous atezolizumab 1200 mg every 3 weeks until disease progression or unacceptable toxicity [see Clinical Studies (14.2)]. Among 198 patients receiving intravenous atezolizumab, 32% were exposed for 6 months or longer and 12% were exposed for 12 months or longer.

Fatal adverse reactions occurred in 2% of patients receiving intravenous atezolizumab. These included pneumonia, respiratory failure, neutropenia, and death (1 patient each).

Serious adverse reactions occurred in 37% of patients receiving intravenous atezolizumab. Serious adverse reactions in > 2% were pneumonia (4.5%), neutropenia (3.5%), febrile neutropenia (2.5%), and thrombocytopenia (2.5%).

Intravenous atezolizumab was discontinued due to adverse reactions in 11% of patients. The most frequent adverse reaction requiring permanent discontinuation in > 2% of patients was infusion-related reactions (2.5%).

Adverse reactions leading to interruption of intravenous atezolizumab occurred in 59% of patients; the most common (> 1%) were neutropenia (22%), anemia (9%), leukopenia (7%), thrombocytopenia (5%), fatigue (4.0%), infusion-related reaction (3.5%), pneumonia (2.0%), febrile neutropenia (1.5%), increased ALT (1.5%), and nausea (1.5%).

Tables 15 and 16 summarize adverse reactions and laboratory abnormalities, respectively, in patients who received intravenous atezolizumab with carboplatin and etoposide in IMpower133.

Table 15: Adverse Reactions Occurring in ≥ 20% of Patients with SCLC Receiving Intravenous Atezolizumab in IMpower133
Adverse Reaction | Intravenous Atezolizumab with Carboplatin and Etoposide N = 198 |  | Placebo with Carboplatin and Etoposide N = 196
Adverse Reaction | All Grades (%) | Grades 3–4 (%) | All Grades (%) | Grades 3–4 (%)
General
Fatigue/Asthenia | 39 | 5 | 33 | 3
Gastrointestinal
Nausea | 38 | 1 | 33 | 1
Constipation | 26 | 1 | 30 | 1
Vomiting | 20 | 2 | 17 | 3
Skin and Subcutaneous Tissue
Alopecia | 37 | 0 | 35 | 0
Metabolism and Nutrition
Decreased appetite | 27 | 1 | 18 | 0
Graded per NCI CTCAE v4.0

Table 16: Laboratory Abnormalities Worsening from Baseline Occurring in ≥ 20% of Patients with SCLC Receiving Intravenous Atezolizumab in IMpower133
Laboratory Abnormality | Intravenous Atezolizumab with Carboplatin and Etoposide |  | Placebo with Carboplatin and Etoposide
Laboratory Abnormality | All Grades (%) | Grades 3–4 (%) | All Grades (%) | Grades 3–4 (%)
Hematology
Anemia | 94 | 17 | 93 | 19
Neutropenia | 73 | 45 | 76 | 48
Thrombocytopenia | 58 | 20 | 53 | 17
Lymphopenia | 46 | 14 | 38 | 11
Chemistry
Hyperglycemia | 67 | 10 | 65 | 8
Increased Alkaline Phosphatase | 38 | 1 | 35 | 2
Hyponatremia | 34 | 15 | 33 | 11
Hypoalbuminemia | 32 | 1 | 30 | 0
Decreased TSH [TSH = thyroid-stimulating hormone. NCI CTCAE v4.0 does not include these laboratories.] | 28 | NA [NA = Not applicable] | 15 | NA
Hypomagnesemia | 31 | 5 | 35 | 6
Hypocalcemia | 26 | 3 | 28 | 5
Increased ALT | 26 | 3 | 31 | 1
Increased AST | 22 | 1 | 21 | 2
Increased Blood Creatinine | 22 | 4 | 15 | 1
Hyperphosphatemia | 21 | NA | 23 | NA
Increased TSH | 21 | NA | 7 | NA
Each test incidence is based on the number of patients who had both baseline and at least one on-study laboratory measurement available: Intravenous Atezolizumab (range: 181–193); Placebo (range: 181–196). Graded per NCI CTCAE v4.0

IMforte

The safety of intravenous atezolizumab in combination with lurbinectedin was evaluated in IMforte [see Clinical Studies (14.2)]. Patients received intravenous atezolizumab 1200 mg IV and lurbinectedin 3.2 mg/m^2 IV, on Day 1 of each 21-day cycle until disease progression or unacceptable toxicity. Primary prophylaxis of G-CSF was administered to 84% of patients. Among 242 patients receiving intravenous atezolizumab with lurbinectedin, the median duration of exposure to intravenous atezolizumab was 4.2 months, with 34% of patients exposed for 6 months or longer and 8% of patients exposed for 12 months or longer.

Serious adverse reactions occurred in 31% of patients receiving intravenous atezolizumab with lurbinectedin. Serious adverse reactions in >2% of patients were pneumonia (2.5%), respiratory tract infection (2.1%), dyspnea (2.1%), and decreased platelet count (2.1%).

Fatal adverse reactions occurred in 5% of patients receiving intravenous atezolizumab with lurbinectedin including pneumonia (3 patients), sepsis (3 patients), cardio-respiratory arrest (2 patients), myocardial infarction (2 patients), and febrile neutropenia (1 patient).

Permanent discontinuation of intravenous atezolizumab due to an adverse reaction occurred in 2.5% of patients. The adverse reactions requiring permanent discontinuation in ≥ 1% of patients who received intravenous atezolizumab were immune-mediated nephritis, peripheral neuropathy, nephropathy, pneumonitis, anemia, neutropenia, and thrombocytopenia.

Dosage interruptions of intravenous atezolizumab due to an adverse reaction occurred in 29% of patients. Adverse reactions which required dosage interruption in ≥ 2% of patients included anemia, fatigue, decreased neutrophil count, pneumonitis, and decreased platelet count.

Tables 17 and 18 summarize adverse reactions and laboratory abnormalities, respectively, in patients who received intravenous atezolizumab with lurbinectedin in IMforte.

Table 17: Adverse Reactions (≥10%) in Patients with ES-SCLC Who Received Intravenous Atezolizumab with Lurbinectedin in IMforte
Adverse Reaction | Intravenous Atezolizumab with Lurbinectedin N = 242 |  | Intravenous Atezolizumab N = 240
Adverse Reaction | All Grades (%) | Grades 3 or 4 (%) | All Grades (%) | Grades 3 or 4 (%)
Gastrointestinal
Nausea | 36 | 3 | 4 | 1
Diarrhea [Includes diarrhea and colitis.] | 15 | 0 | 8 | 0
Vomiting | 14 | 1 | 3 | 0
Constipation | 12 | 0 | 6 | 1
General disorders and administration site conditions
Fatigue [Includes fatigue and asthenia.] | 32 | 5 | 13 | 2
Musculoskeletal and connective tissue disorders
Musculoskeletal Pain [Includes arthralgia, arthritis, back pain, bone pain, musculoskeletal chest pain, musculoskeletal discomfort, musculoskeletal pain, myalgia, neck pain, non-cardiac chest pain, and pain in extremity.] | 19 | 2 | 16 | 1
Metabolism and Nutrition
Decreased appetite | 17 | 0 | 7 | 0
Respiratory, thoracic and mediastinal disorders
Cough [Includes cough, productive cough, and upper-airway cough syndrome.] | 12 | 0 | 8 | 0
Dyspnea [Includes dyspnea and dyspnea exertional.] | 11 | 2 | 10 | 2
Graded per NCI CTCAE v5.0

Clinically relevant adverse reactions in < 10% of patients who received intravenous atezolizumab in combination with lurbinectedin included pneumonia, phlebitis, extravasation resulting in skin necrosis, hypersensitivity and increased creatine phosphokinase.

Table 18: Select Laboratory Abnormalities (≥20%) That Worsened from Baseline in Patients with ES-SCLC Who Received Intravenous Atezolizumab in Combination with Lurbinectedin in IMforte
Laboratory Abnormality | Intravenous Atezolizumab with Lurbinectedin N = 242 |  | Intravenous Atezolizumab N = 240
Laboratory Abnormality | All Grades (%) | Grades 3–4 (%) | All Grades (%) | Grades 3–4 (%)
Hematology
Lymphopenia | 55 | 17 | 31 | 11
Thrombocytopenia | 54 | 15 | 15 | 3
Anemia | 51 | 13 | 12 | 3
Neutropenia | 36 | 18 | 7 | 4
Chemistry
Increased alkaline phosphatase | 29 | 1 | 14 | 0
Decreased sodium | 27 | 4 | 30 | 5
Increased ALT | 25 | 3 | 18 | 2
Increased AST | 24 | 3 | 22 | 1
Decreased calcium | 24 | 3 | 8 | 1
Increased creatinine | 21 | 3 | 14 | 0
Graded per NCI CTCAE v5.0

Adverse Reactions in Adult Patients with Hepatocellular Carcinoma

The safety of TECENTRIQ HYBREZA for its approved indication hepatocellular carcinoma [see Indications and Usage (1.3)] has been established in adequate and well-controlled studies of intravenous atezolizumab for hepatocellular carcinoma (IMbrave150 study).

Hepatocellular Carcinoma

IMbrave150

The safety of intravenous atezolizumab in combination with bevacizumab was evaluated in IMbrave150, a multicenter, international, randomized, open-label trial in patients with locally advanced or metastatic or unresectable hepatocellular carcinoma who have not received prior systemic treatment [see Clinical Studies (14.3)]. Patients received 1,200 mg of intravenous atezolizumab intravenously followed by 15 mg/kg bevacizumab (n = 329) every 3 weeks, or 400 mg of sorafenib (n = 156) given orally twice daily, until disease progression or unacceptable toxicity. The median duration of exposure to intravenous atezolizumab was 7.4 months (range: 0–16 months) and to bevacizumab was 6.9 months (range: 0–16 months).

Fatal adverse reactions occurred in 4.6% of patients in the intravenous atezolizumab and bevacizumab arm. The most common adverse reactions leading to death were gastrointestinal and esophageal varices hemorrhage (1.2%) and infections (1.2%).

Serious adverse reactions occurred in 38% of patients in the intravenous atezolizumab and bevacizumab arm. The most frequent serious adverse reactions (≥ 2%) were gastrointestinal hemorrhage (7%), infections (6%), and pyrexia (2.1%).

Adverse reactions leading to discontinuation of intravenous atezolizumab occurred in 9% of patients in the intravenous atezolizumab and bevacizumab arm. The most common adverse reactions leading to intravenous atezolizumab discontinuation were hemorrhages (1.2%), including gastrointestinal, subarachnoid, and pulmonary hemorrhages; increased transaminases or bilirubin (1.2%); infusion-related reaction/cytokine release syndrome (0.9%); and autoimmune hepatitis (0.6%).

Adverse reactions leading to interruption of intravenous atezolizumab occurred in 41% of patients in the intravenous atezolizumab and bevacizumab arm; the most common (≥ 2%) were liver function laboratory abnormalities including increased transaminases, bilirubin, or alkaline phosphatase (8%); infections (6%); gastrointestinal hemorrhages (3.6%); thrombocytopenia/decreased platelet count (3.6%); hyperthyroidism (2.7%); and pyrexia (2.1%).

Immune-related adverse reactions requiring systemic corticosteroid therapy occurred in 12% of patients in the intravenous atezolizumab and bevacizumab arm.

Tables 19 and 20 summarize adverse reactions and laboratory abnormalities, respectively, in patients who received intravenous atezolizumab and bevacizumab in IMbrave150.

Table 19: Adverse Reactions Occurring in ≥ 10% of Patients with HCC Receiving Intravenous Atezolizumab in IMbrave150
Adverse Reaction | Intravenous Atezolizumab in combination with Bevacizumab (n = 329) |  | Sorafenib (n = 156)
Adverse Reaction | All Grades [Graded per NCI CTCAE v4.0] (%) | Grades 3–4 (%) | All Grades (%) | Grades 3–4 (%)
Vascular Disorders
Hypertension | 30 | 15 | 24 | 12
General Disorders and Administration Site Conditions
Fatigue/Asthenia [Includes fatigue and asthenia] | 26 | 2 | 32 | 6
Pyrexia | 18 | 0 | 10 | 0
Renal and Urinary Disorders
Proteinuria | 20 | 3 | 7 | 0.6
Investigations
Weight Decreased | 11 | 0 | 10 | 0
Skin and Subcutaneous Tissue Disorders
Pruritus | 19 | 0 | 10 | 0
Rash | 12 | 0 | 17 | 2.6
Gastrointestinal Disorders
Diarrhea | 19 | 1.8 | 49 | 5
Constipation | 13 | 0 | 14 | 0
Abdominal Pain | 12 | 0 | 17 | 0
Nausea | 12 | 0 | 16 | 0
Vomiting | 10 | 0 | 8 | 0
Metabolism and Nutrition Disorders
Decreased Appetite | 18 | 1.2 | 24 | 3.8
Respiratory, Thoracic and Mediastinal Disorders
Cough | 12 | 0 | 10 | 0
Epistaxis | 10 | 0 | 4.5 | 0
Injury, Poisoning and Procedural Complications
Infusion-Related Reaction | 11 | 2.4 | 0 | 0

Table 20: Laboratory Abnormalities Worsening from Baseline Occurring in ≥ 20% of Patients with HCC Receiving Intravenous Atezolizumab in IMbrave150
Laboratory Abnormality | Intravenous Atezolizumab in combination with Bevacizumab (n = 329) |  | Sorafenib (n = 156)
Laboratory Abnormality | All Grades [Graded per NCI CTCAE v4.0] (%) | Grades 3–4 (%) | All Grades (%) | Grades 3–4 (%)
Chemistry
Increased AST | 86 | 16 | 90 | 16
Increased Alkaline Phosphatase | 70 | 4 | 76 | 4.6
Increased ALT | 62 | 8 | 70 | 4.6
Decreased Albumin | 60 | 1.5 | 54 | 0.7
Decreased Sodium | 54 | 13 | 49 | 9
Increased Glucose | 48 | 9 | 43 | 4.6
Decreased Calcium | 30 | 0.3 | 35 | 1.3
Decreased Phosphorus | 26 | 4.7 | 58 | 16
Increased Potassium | 23 | 1.9 | 16 | 2
Hypomagnesemia | 22 | 0 | 22 | 0
Hematology
Decreased Platelet | 68 | 7 | 63 | 4.6
Decreased Lymphocytes | 62 | 13 | 58 | 11
Decreased Hemoglobin | 58 | 3.1 | 62 | 3.9
Increased Bilirubin | 57 | 8 | 59 | 14
Decreased Leukocyte | 32 | 3.4 | 29 | 1.3
Decreased Neutrophil | 23 | 2.3 | 16 | 1.1
Each test incidence is based on the number of patients who had both baseline and at least one on-study laboratory measurement available: intravenous atezolizumab plus bevacizumab (222-323) and sorafenib (90-153)

Adverse Reactions in Adult Patients with Melanoma

The safety of TECENTRIQ HYBREZA for its approved melanoma indication [see Indications and Usage (1.4)] has been established in adequate and well-controlled studies of intravenous atezolizumab for melanoma (IMspire150 study).

Metastatic Melanoma

IMspire150

The safety of intravenous atezolizumab, administered with cobimetinib and vemurafenib, was evaluated in IMspire150, a double-blind, randomized (1:1), placebo-controlled study conducted in patients with previously untreated BRAF V600 mutation-positive metastatic or unresectable melanoma [see Clinical Studies (14.4)]. Patients received intravenous atezolizumab with cobimetinib and vemurafenib (n = 230) or placebo with cobimetinib and vemurafenib (n = 281).

Among the 230 patients who received intravenous atezolizumab administered with cobimetinib and vemurafenib, the median duration of exposure to intravenous atezolizumab was 9.2 months (range: 0–30 months), to cobimetinib was 10.0 months (range: 1–31 months) and to vemurafenib was 9.8 months (range: 1–31 months).

Fatal adverse reactions occurred in 3% of patients in the intravenous atezolizumab plus cobimetinib and vemurafenib arm. Adverse reactions leading to death were hepatic failure, fulminant hepatitis, sepsis, septic shock, pneumonia, and cardiac arrest.

Serious adverse reactions occurred in 45% of patients in the intravenous atezolizumab plus cobimetinib and vemurafenib arm. The most frequent (≥ 2%) serious adverse reactions were hepatotoxicity (7%), pyrexia (6%), pneumonia (4.3%), malignant neoplasms (2.2%), and acute kidney injury (2.2%).

Adverse reactions leading to discontinuation of intravenous atezolizumab occurred in 21% of patients in the intravenous atezolizumab plus cobimetinib and vemurafenib arm. The most frequent (≥ 2%) adverse reactions leading to intravenous atezolizumab discontinuation were increased ALT (2.2%) and pneumonitis (2.6%).

Adverse reactions leading to interruption of intravenous atezolizumab occurred in 68% of patients in the intravenous atezolizumab plus cobimetinib and vemurafenib arm. The most frequent (≥ 2%) adverse reactions leading to intravenous atezolizumab interruption were pyrexia (14%), increased ALT (13%), hyperthyroidism (10%), increased AST (10%), increased lipase (9%), increased amylase (7%), pneumonitis (5%), increased CPK (4.3%), diarrhea (3.5%), pneumonia (3.5%), asthenia (3%), rash (3%), influenza (3%), arthralgia (2.6%), fatigue (2.2%), dyspnea (2.2%), cough (2.2%), peripheral edema (2.2%), uveitis (2.2%), bronchitis (2.2%), hypothyroidism (2.2%), and respiratory tract infection (2.2%).

Tables 21 and 22 summarize the incidence of adverse reactions and laboratory abnormalities in IMspire150.

Table 21: Adverse Reactions Occurring in ≥ 10% of Patients on the Intravenous Atezolizumab plus Cobimetinib and Vemurafenib Arm or the Placebo plus Cobimetinib and Vemurafenib Arm and at a Higher Incidence (Between Arm Difference of ≥ 5% All Grades or ≥ 2% Grades 3-4 Intravenous Atezolizumab in IMspire150)
Adverse Reaction | Intravenous Atezolizumab in combination with Cobimetinib and Vemurafenib (n=230) |  | Placebo with Cobimetinib and Vemurafenib (n=281)
Adverse Reaction | All Grades (%) | Grades 3–4 (%) | All Grades (%) | Grades 3–4 (%)
Skin and Subcutaneous Tissue Disorders
Rash [Includes rash, rash maculo-papular, dermatitis acneiform, rash macular, rash erythematous, eczema, skin exfoliation, rash papular, rash pustular, palmar-plantar erythrodysesthesia syndrome, dermatitis, dermatitis contact, erythema multiforme, rash pruritic, drug eruption, nodular rash, dermatitis allergic, exfoliative rash, dermatitis exfoliative generalized and rash morbilliform] | 75 | 27 | 72 | 23
Pruritus | 26 | < 1 | 17 | < 1
Photosensitivity reaction | 21 | < 1 | 25 | 3.2
General Disorders and Administration Site Conditions
Fatigue [Includes fatigue, asthenia and malaise] | 51 | 3 | 45 | 1.8
Pyrexia [Includes pyrexia and hyperpyrexia] | 49 | 1.7 | 35 | 2.1
Edema [Includes edema peripheral, lymphoedema, edema, face edema, eyelid edema, periorbital edema, lip edema and generalized edema] | 26 | < 1 | 21 | 0
Gastrointestinal Disorders
Hepatotoxicity [Includes alanine aminotransferase increased, aspartate aminotransferase increased, blood bilirubin increased, transaminases increased, hepatitis, hepatic enzyme increased, hepatotoxicity, hypertransaminasemia, bilirubin conjugated increased, hepatocellular injury, hyperbilirubinemia, liver function test increased, hepatic failure, hepatitis fulminant and liver function test abnormal] | 50 | 21 | 36 | 13
Nausea | 30 | < 1 | 32 | 2.5
Stomatitis [Includes stomatitis, mucosal inflammation, aphthous ulcer, mouth ulceration, cheilitis and glossitis] | 23 | 1.3 | 15 | < 1
Musculoskeletal and Connective Tissue Disorders
Musculoskeletal pain [Includes arthralgia, myalgia, pain in extremity, back pain, musculoskeletal pain, arthritis, neck pain, musculoskeletal chest pain, musculoskeletal stiffness, bone pain, spinal pain, immune-mediated arthritis, joint stiffness and non-cardiac chest pain] | 62 | 4.3 | 48 | 3.2
Endocrine Disorders
Hypothyroidism [Includes hypothyroidism and blood thyroid stimulating hormone increased] | 22 | 0 | 10 | 0
Hyperthyroidism | 18 | < 1 | 8 | 0
Injury, Poisoning and Procedural Complications
Infusion-related reaction [Includes infusion related reaction and hypersensitivity] | 10 | 2.6 | 8 | < 1
Respiratory, Thoracic and Mediastinal Disorders
Pneumonitis [Includes pneumonitis and interstitial lung disease] | 12 | 1.3 | 6 | < 1
Vascular Disorders
Hypertension [Includes hypertension, blood pressure increased, hypertensive crisis] | 17 | 10 | 18 | 7

Clinically important adverse reactions in < 10% of patients who received intravenous atezolizumab plus cobimetinib and vemurafenib were:

Cardiac Disorders: Arrhythmias, ejection fraction decreased, electrocardiogram QT prolonged

Eye Disorders: Uveitis

Gastrointestinal disorders: Pancreatitis

Infections and infestations: Pneumonia, urinary tract infection

Metabolism and nutrition disorders: Hyperglycemia

Nervous system Disorders: Dizziness, dysgeusia, syncope

Respiratory, thoracic and mediastinal disorders: Dyspnea, oropharyngeal pain

Skin and Subcutaneous Tissue Disorders: Vitiligo

Table 22: Laboratory Abnormalities Worsening from Baseline Occurring in ≥ 20% of Patients Receiving Intravenous Atezolizumab Plus Cobimetinib and Vemurafenib Arm or the Placebo Plus Cobimetinib and Vemurafenib Arm and at a Higher Incidence (Between Arm Difference of ≥ 5% All Grades or ≥ 2% Grades 3–4) in IMspire150
Laboratory Abnormality | Intravenous Atezolizumab in combination with Cobimetinib and Vemurafenib (n=230) |  | Placebo with Cobimetinib and Vemurafenib (n=281)
Laboratory Abnormality | All Grades (%) | Grades 3–4 (%) | All Grades (%) | Grades 3–4 (%)
Hematology
Decreased Lymphocytes | 80 | 24 | 72 | 17
Decreased Hemoglobin | 77 | 2.6 | 72 | 2.2
Decreased Platelet | 34 | 1.3 | 24 | 0.4
Decreased Neutrophils | 26 | 2.2 | 19 | 1.5
Chemistry
Increased Creatine Kinase | 88 | 22 | 81 | 18
Increased AST | 80 | 13 | 68 | 6
Increased ALT | 79 | 18 | 62 | 12
Increased Triacylglycerol Lipase | 75 | 46 | 62 | 35
Increased Alkaline Phosphatase | 73 | 6 | 63 | 2.9
Decreased Phosphorus | 67 | 22 | 64 | 14
Increased Amylase | 51 | 13 | 45 | 13
Increased Blood Urea Nitrogen | 47 | NA [NA = Not applicable. NCI CTCAE v4.0 does not include these laboratories] | 37 | NA
Decreased Albumin | 43 | 0.9 | 34 | 1.5
Increased Bilirubin | 42 | 3.1 | 33 | 0.7
Decreased Calcium | 41 | 1.3 | 28 | 0
Decreased Sodium | 40 | 5 | 34 | 7
Decreased Thyroid-Stimulating Hormone | 38 | NA | 23 | NA
Increased Thyroid-Stimulating Hormone [Increased Thyroid Stimulating Hormone has a difference < 5% (All Grades) between arms and is included for clinical completeness] | 37 | NA | 33 | NA
Decreased Potassium | 36 | 5 | 22 | 4.3
Increased Triiodothyronine | 33 | NA | 18 | NA
Increased Free Thyroxine | 32 | NA | 21 | NA
Decreased Total Triiodothyronine | 32 | NA | 8 | NA
Increased Potassium | 29 | 1.3 | 19 | 1.4
Decreased Triiodothyronine | 27 | NA | 21 | NA
Increased Sodium | 20 | 0 | 13 | 0.4
Graded per NCI CTCAE v4.0.
Each test incidence is based on the number of patients who had both baseline and at least one on-study laboratory measurement available: intravenous atezolizumab plus cobimetinib and vemurafenib (28-277), placebo plus cobimetinib and vemurafenib arm (25-230).

Adverse Reactions in Adults with Alveolar Soft Part Sarcoma

The safety of TECENTRIQ HYBREZA for its approved alveolar soft part sarcoma (ASPS) indication [see Indications and Usage (1.5)] has been established in adequate and well-controlled studies of intravenous atezolizumab for ASPS (ML39345 study).

Alveolar Soft Part Sarcoma

ML39345 Study

The safety of intravenous atezolizumab was evaluated in 47 adult and 2 pediatric patients enrolled in Study ML39345 [see Clinical Studies (14.5)]. Adult patients received intravenous atezolizumab 1200 mg every 3 weeks and pediatric patients received 15 mg/kg up to a maximum 1200 mg every 3 weeks until disease progression or unacceptable toxicity. The median duration of exposure to intravenous atezolizumab was 8.9 months (1 to 40 months).

Serious adverse reactions occurred in 41% of patients receiving intravenous atezolizumab. The most frequent serious adverse reactions (> 2%) were fatigue, pain in extremity, pulmonary hemorrhage, and pneumonia (4.1% each).

Dosage interruptions of intravenous atezolizumab due to an adverse reaction occurred in 35% of patients. The most common adverse reactions (≥ 3%) leading to dose interruptions were pneumonitis and pain in extremity (4.1% each).

Tables 23 and 24 summarize adverse reactions and laboratory abnormalities in Study ML39345.

Table 23: Adverse Reactions Occurring in ≥ 15% of Patients with ASPS Receiving Intravenous Atezolizumab in ML39345
Adverse Reaction | Intravenous Atezolizumab N = 49
Adverse Reaction | All Grades (%) | Grades 3–4 (%)
General disorders and administration site conditions
Fatigue | 55 | 2
Pyrexia | 25 | 2
Influenza like illness | 18 | 0
Gastrointestinal disorders
Nausea | 43 | 0
Vomiting | 37 | 0
Constipation | 33 | 0
Diarrhea | 27 | 2
Abdominal pain [Includes abdominal pain and abdominal pain upper] | 25 | 0
Metabolism and nutrition disorders
Decreased appetite | 22 | 2
Respiratory, Thoracic and Mediastinal
Cough [Includes cough, upper-airway cough syndrome, and productive cough] | 45 | 0
Dyspnea | 33 | 0
Rhinitis allergic | 16 | 0
Musculoskeletal and connective tissue disorders
Musculoskeletal pain [Includes arthralgia, pain in extremity, myalgia, non-cardiac chest pain, neck pain, musculoskeletal chest pain, and back pain] | 67 | 8
Skin and subcutaneous tissue disorders
Rash [Includes rash maculo-papular, rash, dermatitis acneiform, eczema, skin exfoliation, and drug eruption] | 47 | 2
Nervous system disorders
Headache | 43 | 4
Dizziness [Includes vertigo and dizziness] | 29 | 4
Vascular disorders
Hypertension | 43 | 6
Hemorrhage [Includes pulmonary hemorrhage, hemoptysis, conjunctival hemorrhage, epistaxis, hematuria, rectal hemorrhage, and laryngeal hemorrhage] | 29 | 2
Psychiatric disorders
Insomnia | 27 | 0
Anxiety | 25 | 0
Cardiac Disorders
Arrhythmia [Includes atrial fibrillation, sinus bradycardia, ventricular tachycardia, and sinus tachycardia] | 22 | 2
Endocrine disorders
Hypothyroidism [Includes hypothyroidism and blood thyroid stimulating hormone increased] | 25 | 0
Investigations
Weight decreased | 18 | 0
Weight increased | 16 | 6
Graded per NCI CTCAE v4.0

Table 24: Laboratory Abnormalities Worsening from Baseline Occurring in ≥ 20% of Patients with ASPS Receiving Intravenous Atezolizumab in ML39345
Laboratory Abnormality [Laboratory tests which do not have NCI CTCAE grading criteria are also included for All Grade assessments, which were performed by comparing to respective lab normal ranges] | Intravenous Atezolizumab [The denominators used to calculate the rate varied from 4–49 for all tests of interest based on the number of patients with a baseline value and at least one on-study laboratory measurement available]
Laboratory Abnormality [Laboratory tests which do not have NCI CTCAE grading criteria are also included for All Grade assessments, which were performed by comparing to respective lab normal ranges] | All Grades (%) | Grades 3–4 (%)
Hematology
Decreased Hemoglobin | 63 | 0
Decreased Platelets | 27 | 0
Increased Platelets | 29 | 0
Chemistry
Increased Alkaline Phosphatase | 29 | 0
Decreased Amylase | 40 | 0
Increased Amylase | 20 | 20
Decreased Bilirubin | 49 | 0
Decreased Calcium | 47 | 0
Increased Calcium | 25 | 14
Decreased Glucose | 33 | 0
Increased Glucose | 78 | 0
Decreased Glucose (fasting) | 25 | 0
Decreased Magnesium | 21 | 0
Increased Magnesium | 26 | 26
Increased AST | 39 | 2
Increased ALT | 33 | 2
Decreased Sodium | 43 | 0
Increased Lipase | 25 | 25

6.2 Postmarketing Experience

The following adverse reactions have been identified during post-approval use of intravenous atezolizumab. Because these reactions are reported voluntarily from a population of uncertain size, it is not always possible to reliably estimate their frequency or establish a causal relationship to drug exposure.

- Cardiac: pericarditis, pericardial effusion, cardiac tamponade
- Musculoskeletal and Connective Tissue: tenosynovitis

8 USE IN SPECIFIC POPULATIONS

8.1 Pregnancy

Risk Summary

Based on its mechanism of action [see Clinical Pharmacology (12.1)], TECENTRIQ HYBREZA can cause fetal harm when administered to a pregnant woman. There are no available data on the use of TECENTRIQ HYBREZA in pregnant women.

Animal studies have demonstrated that inhibition of the PD-L1/PD-1 pathway can lead to increased risk of immune-related rejection of the developing fetus resulting in fetal death (see Data). Advise females of reproductive potential of the potential risk to a fetus [see Warnings and Precautions (5.4)].

In the U.S. general population, the estimated background risk of major birth defects and miscarriage in clinically recognized pregnancies is 2% to 4% and 15% to 20%, respectively.

Data

Animal Data:

TECENTRIQ HYBREZA for subcutaneous injection contains atezolizumab and hyaluronidase [see Description (11)].

Atezolizumab: Animal reproduction studies have not been conducted with atezolizumab to evaluate its effect on reproduction and fetal development. A literature-based assessment of the effects on reproduction demonstrated that a central function of the PD-L1/PD-1 pathway is to preserve pregnancy by maintaining maternal immune tolerance to a fetus. Blockage of PD-L1 signaling has been shown in murine models of pregnancy to disrupt tolerance to a fetus and to result in an increase in fetal loss; therefore, potential risks of administering atezolizumab during pregnancy include increased rates of abortion or stillbirth. As reported in the literature, there were no malformations related to the blockade of PD-L1/PD-1 signaling in the offspring of these animals; however, immune-mediated disorders occurred in PD-1 and PD-L1 knockout mice. Based on its mechanism of action, fetal exposure to atezolizumab may increase the risk of developing immune-mediated disorders or altering the normal immune response.

Hyaluronidase: In an embryo-fetal study, mice were dosed daily by subcutaneous injection during the period of organogenesis with hyaluronidase (recombinant human) at dose levels up to 2,200,000 U/kg, which is > 2,400 times higher than the human dose. The study found no evidence of teratogenicity. Reduced fetal weight and increased numbers of fetal resorptions were observed, with no effects found at a daily dose of 360,000 U/kg, which is > 400 times higher than the human dose.

In a peri-and post-natal reproduction study, mice have been dosed daily by subcutaneous injection, with hyaluronidase (recombinant human) from implantation through lactation and weaning at dose levels up to 1,100,000 U/kg, which is > 1,200 times higher than the human dose. The study found no adverse effects on sexual maturation, learning and memory or fertility of the offspring.

8.2 Lactation

Risk Summary

There is no information regarding the presence of atezolizumab or hyaluronidase in human milk or its effects on the breastfed child, or on milk production. Maternal IgG is known to be present in human milk. The effects of local gastrointestinal exposure and limited systemic exposure in the breastfed child to TECENTRIQ HYBREZA are unknown. Because of the potential for serious adverse reactions in breastfed children from TECENTRIQ HYBREZA, advise women not to breastfeed during treatment with TECENTRIQ HYBREZA and for 5 months after the last dose.

8.3 Females and Males of Reproductive Potential

Based on its mechanism of action, TECENTRIQ HYBREZA can cause fetal harm when administered to a pregnant woman [see Use in Specific Populations (8.1)].

Pregnancy Testing

Verify pregnancy status in females of reproductive potential prior to initiating TECENTRIQ HYBREZA [see Warnings and Precautions (5.4) and Use in Specific Populations (8.1)].

Contraception

Females: Advise females of reproductive potential to use effective contraception during treatment with TECENTRIQ HYBREZA and for 5 months following the last dose.

Infertility

Females: Based on animal studies, TECENTRIQ HYBREZA may impair fertility in females of reproductive potential while receiving TECENTRIQ HYBREZA treatment [see Nonclinical Toxicology (13.1)].

8.4 Pediatric Use

Alveolar Soft Part Sarcoma

The safety and effectiveness of TECENTRIQ HYBREZA as monotherapy for the treatment of pediatric patients (12 years of age and older who weigh 40 kg or greater) with unresectable or metastatic alveolar soft part sarcoma (ASPS) has been established. Use of TECENTRIQ HYBREZA for this pediatric indication is supported by evidence from adequate and well controlled studies of intravenous atezolizumab in adults, and additional pharmacokinetic and safety data for intravenous atezolizumab in pediatric patients 12 years and older [see Adverse Reactions (6.1) and Clinical Studies (14)]. Atezolizumab exposures following subcutaneous administration of TECENTRIQ HYBREZA (containing 1,875 mg of atezolizumab) every 3 weeks in pediatric patients 12 years of age and older who weigh 40 kg or greater are predicted to be within the range of those observed in adults at the same dosage.

The safety and effectiveness of TECENTRIQ HYBREZA have not been established in pediatric patients <12 years of age with unresectable or metastatic ASPS.

Solid Tumors and Lymphomas

The safety and effectiveness of TECENTRIQ HYBREZA in pediatric patients have not been established for other approved indications.

8.5 Geriatric Use

TECENTRIQ HYBREZA as a Single-Agent

Of 247 adult patients treated with TECENTRIQ HYBREZA as monotherapy in IMscin001, 45% were 65 years and over and 10% were 75 years and over. No overall differences in safety or effectiveness of TECENTRIQ HYBREZA have been observed between patients aged 65 years or older and younger adult patients.

The safety of TECENTRIQ HYBREZA as monotherapy or in combination with other antineoplastic drugs for its approved indications [see Indications and Usage (1.1, 1.2, 1.3, 1.4, 1.5)] has been established in adequate and well-controlled studies of intravenous atezolizumab as a single agent and in combination with other antineoplastic drugs. Below is a description of geriatric use information from the intravenous atezolizumab studies.

Intravenous Atezolizumab as a Single-Agent

Of 2,616 adult patients with metastatic NSCLC and other tumor types treated with monotherapy intravenous atezolizumab in clinical studies, 49% were 65 years and over and 15% were 75 years and over. No overall differences in safety or effectiveness were observed between intravenous atezolizumab-treated patients aged 65 years or older and younger patients.

Intravenous Atezolizumab in Combination with Other Antineoplastic Drugs

Of 2,421 adult patients with NSCLC and EC-SCLC treated with intravenous atezolizumab in combination with other antineoplastic drugs in clinical studies, 48% were 65 years and over and 10% were 75 years and over. No overall differences in safety or effectiveness were observed between intravenous atezolizumab-treated patients aged 65 years or older and younger adult patients.

Intravenous Atezolizumab in Combination with Lurbinectedin

Of 242 adult patients with ES-SCLC treated with intravenous atezolizumab in combination with lurbinectedin in IMforte, 124 (51%) patients were 65 years of age and older, while 29 (12%) patients were 75 years of age and older. No overall differences in effectiveness were observed between older and younger patients. There was a higher incidence of Grade 3 or 4 adverse reactions (45% vs 31%) and treatment discontinuation (11% vs 0.8%) in patients ≥ 65 years of age compared to younger patients, respectively.

11 DESCRIPTION

TECENTRIQ HYBREZA is a fixed-combination drug product containing atezolizumab and hyaluronidase (human recombinant).

- Atezolizumab is a programmed cell death ligand 1 (PD-L1) blocking antibody. Atezolizumab is an Fc-engineered, humanized, non-glycosylated IgG1 kappa immunoglobulin that has a calculated molecular mass of 145 kDa.
- Hyaluronidase (human recombinant) is an endoglycosidase used to increase the dispersion and absorption of co-administered drugs administered subcutaneously. It is a glycosylated single-chain protein produced by mammalian (Chinese Hamster Ovary) cells containing a DNA plasmid encoding for a soluble fragment of human hyaluronidase (PH20). Hyaluronidase (human recombinant) has a molecular weight of approximately 61 kDa.

TECENTRIQ HYBREZA (atezolizumab and hyaluronidase-tqjs) injection for subcutaneous use is a sterile, preservative-free, clear and slightly opalescent, and colorless to slightly yellow solution in single-dose vials. Each 15 mL single-dose vial contains 1,875 mg of atezolizumab, 30,000 units of hyaluronidase, histidine (46.5 mg), methionine (22.4 mg), polysorbate 20 (9 mg), sucrose (1,232 mg), and water for injection, adjusted to pH 5.8 with acetic acid.

12 CLINICAL PHARMACOLOGY

12.1 Mechanism of Action

PD-L1 may be expressed on tumor cells and/or tumor infiltrating immune cells and can contribute to the inhibition of the anti-tumor immune response in the tumor microenvironment. Binding of PD-L1 to the PD-1 and B7.1 receptors found on T-cells and antigen presenting cells suppresses cytotoxic T-cell activity, T-cell proliferation and cytokine production.

Atezolizumab is a monoclonal antibody that binds to PD-L1 and blocks its interactions with both PD-1 and B7.1 receptors. This releases the PD-L1/PD-1 mediated inhibition of the immune response, including activation of the anti-tumor immune response without inducing antibody-dependent cellular cytotoxicity. In syngeneic mouse tumor models, blocking PD-L1 activity resulted in decreased tumor growth.

In mouse models of cancer, dual inhibition of the PD-1/PD-L1 and MAPK pathways suppresses tumor growth and improves tumor immunogenicity through increased antigen presentation and T-cell infiltration and activation compared to targeted therapy alone.

Hyaluronan is a polysaccharide found in the extracellular matrix of the subcutaneous tissue. It is depolymerized by the naturally occurring enzyme hyaluronidase. Unlike the stable structural components of the interstitial matrix, hyaluronan has a half-life of approximately 0.5 days.

Hyaluronidase increases permeability of the subcutaneous tissue by depolymerizing hyaluronan. In the doses administered, hyaluronidase in TECENTRIQ HYBREZA acts transiently and locally. The effects of hyaluronidase are reversible and permeability of the subcutaneous tissue is restored within 24 to 48 hours.

12.2 Pharmacodynamics

The exposure-response relationship and time course of pharmacodynamic response for the safety and effectiveness of atezolizumab and hyaluronidase have not been fully characterized.

12.3 Pharmacokinetics

When comparing atezolizumab exposure following subcutaneous TECENTRIQ HYBREZA to that of intravenous atezolizumab in Study IMscin001 [see Clinical Studies (14.1)], the geometric mean ratio (GMR) (90% CI) for Cycle 1 Ctrough was 1.05 (0.88, 1.24) and AUC0-21days was 0.87 (0.83, 0.92); the steady state Ctrough was 1.15 (1.05, 1.26) and AUC was 1.01 (0.94, 1.08).

Steady-state was achieved 6 to 9 weeks. The systemic accumulation ratio following administration of the approved recommended dosage of TECENTRIQ HYBREZA was 2.2.

Absorption

The mean absolute bioavailability (CV%) of atezolizumab was 72% (83%) and the median time (range) to reach maximum atezolizumab concentration (Tmax) was 4.5 (2.2, 9) days.

Distribution

The volume of distribution of atezolizumab at steady state was 6.9 L.

Elimination

The atezolizumab clearance (CV%) was 0.2 L/day (29%) and the terminal half-life was 27 days. Atezolizumab clearance decreased over time, with a mean maximal reduction (CV%) from baseline value of 17% (41%); this decrease in clearance is not considered clinically significant.

Specific Populations

No clinically significant differences in the pharmacokinetics of atezolizumab were observed based on age, body weight, sex, albumin levels, tumor burden, region, race, mild or moderate renal impairment (estimated glomerular filtration rate 30 to 89 mL/minute/1.73 m^2), mild hepatic impairment (bilirubin ≤ ULN and AST > ULN or bilirubin > 1 to 1.5 × ULN and any AST), moderate hepatic impairment (bilirubin >1.5 to 3× ULN and any AST), level of PD-L1 expression, and performance status.

Pediatric patients

Atezolizumab exposure following subcutaneous administration of atezolizumab 1875 mg and 30,000 units hyaluronidase every 3 weeks in pediatric patients aged 12 years and older who weigh 40 kg or greater is predicted to be within range of those observed in adult patients at the same dosage.

12.6 Immunogenicity

The observed incidence of anti-drug antibodies (ADA) is highly dependent on the sensitivity and specificity of the assay. Differences in assay methods preclude meaningful comparisons of the incidence of ADA in the studies described below with the incidence of ADA in other studies, including those of TECENTRIQ HYBREZA or of other atezolizumab products or hyaluronidase products.

During the first year of treatment in the Study IMscin001 [see Clinical Studies (14.1)], the incidence of ADA was 20% (43/221) and the incidence of neutralizing antibodies (NAb) in ADA-positive patients was 54% (21/39) for TECENTRIQ HYBREZA. The corresponding incidence of ADA was 14% (15/108) and NAb was 60% (9/15) for intravenous atezolizumab.

In Study IMscin001, atezolizumab clearance increased by 29% in patients who received TECENTRIQ HYBREZA and who tested positive for ADA, compared to patients who tested negative for ADA; this change in clearance is not expected to be clinically significant. Because of limited immunogenicity data the effect of ADA on the effectiveness of TECENTRIQ HYBREZA is unknown. There was no identified clinically significant effect of anti-atezolizumab antibodies on the safety of TECENTRIQ HYBREZA during the first 6 months of treatment.

In Study IMscin001, the incidence of anti-rHuPH20 antibodies was 5.4% (12/224) and the incidence of NAb was 0% (0/12). Because of the low occurrence of anti-rHuPH20 antibodies, the effect of these antibodies on the pharmacokinetics, pharmacodynamics and/or safety of hyaluronidase in TECENTRIQ HYBREZA is unknown.

Immunogenicity with Other Clinical Trials with Intravenous Atezolizumab:

During the first year of treatment with intravenous atezolizumab across clinical studies of patients with NSCLC, SCLC, HCC, and melanoma 13% to 36% of patients developed anti-atezolizumab antibodies. Across clinical studies, the NAb incidence in ADA-positive patients was 24% to 83%.

In OAK and IMbrave150, exploratory analyses showed that the subset of patients who were ADA-positive appeared to have less efficacy (effect on overall survival) as compared to patients who tested negative for ADA [see Clinical Studies (14.1, 14.3)]. In study IMpower150 and IMforte, the impact of ADA on efficacy did not appear to be clinically significant [see Clinical Studies (14.1)]. In the remaining studies, there is insufficient information to characterize the effect of ADA on efficacy.

Median atezolizumab clearance in patients who tested positive for ADA was 19% (range of 18% to 49%) higher as compared to atezolizumab clearance in patients who tested negative for ADA; this change in clearance is not expected to be clinically significant. The presence of ADA did not have a clinically significant effect on the incidence or severity of adverse reactions. The effect of NAb on atezolizumab exposure and safety did not appear to be clinically significant. The effect of NAb on key efficacy endpoints is uncertain due to small sample sizes.

13 NONCLINICAL TOXICOLOGY

13.1 Carcinogenesis, Mutagenesis, Impairment of Fertility

No studies have been performed to test the potential of atezolizumab for carcinogenicity or genotoxicity.

Animal fertility studies have not been conducted with atezolizumab; however, an assessment of the male and female reproductive organs was included in a 26-week, repeat-dose toxicity study in cynomolgus monkeys. Weekly administration of atezolizumab to female monkeys at the highest dose tested caused an irregular menstrual cycle pattern and a lack of newly formed corpora lutea in the ovaries. This effect occurred at an estimated AUC approximately 6 times the AUC in patients receiving the recommended intravenous atezolizumab dose and was reversible. There was no effect on the male monkey reproductive organs.

Hyaluronidases are found in most tissues of the body. Long-term animal studies have not been performed to assess the carcinogenic or mutagenic potential of hyaluronidase. In addition, when up to 220,000 units/kg of subcutaneous hyaluronidase (recombinant human) was administered to cynomolgus monkeys for 39 weeks, which is > 223 times higher than the human recommended dose for hyaluronidase, no evidence of toxicity to the male or female reproductive system was found through periodic monitoring of in-life parameters (e.g., semen analyses, hormone levels, menstrual cycles, and also from gross pathology, histopathology and organ weight data).

13.2 Animal Toxicology and/or Pharmacology

In animal models, inhibition of PD-L1/PD-1 signaling increased the severity of some infections and enhanced inflammatory responses. Mycobacterium tuberculosis-infected PD-1 knockout mice exhibit markedly decreased survival compared with wild-type controls, which correlated with increased bacterial proliferation and inflammatory responses in these animals. PD-L1 and PD-1 knockout mice and mice receiving PD-L1 blocking antibody have also shown decreased survival following infection with lymphocytic choriomeningitis virus.

14 CLINICAL STUDIES

14.1 Non-Small Cell Lung Cancer

NSCLC - TECENTRIQ HYBREZA

IMscin001 (NCT03735121) was an open-label, multi-center, international, randomized study conducted in adult patients with locally advanced or metastatic NSCLC who were not exposed to cancer immunotherapy and who have disease progression following platinum-based chemotherapy. Patients were excluded if they had a history of autoimmune disease; active or corticosteroid-dependent brain metastases; received a live, attenuated vaccine within 4 weeks prior to randomization; or received systemic immunostimulatory agents within 4 weeks or systemic immunosuppressive drugs within 2 weeks prior to randomization. A total of 371 patients were randomized 2:1 to receive either TECENTRIQ HYBREZA (containing 1,875 mg of atezolizumab and 30,000 units of hyaluronidase) administered subcutaneously in the thigh every 3 weeks (n = 247) or intravenous atezolizumab 1,200 mg every 3 weeks (n = 124) until disease progression or unacceptable toxicity.

The primary outcome measure was atezolizumab exposure (Ctrough and AUC0-21days) of subcutaneous TECENTRIQ HYBREZA as compared to intravenous atezolizumab [see Clinical Pharmacology (12.3)]. Additional descriptive efficacy outcome measures were overall response rate (ORR), progression-free survival (PFS) and overall survival (OS).

The median age was 64 years (range: 27 to 85); 69% were male; 67% were White, 22% were Asian, and 0.8% were Black or African American; 74% were non-Hispanic or Latino; 26% had an Eastern Cooperative Oncology Group (ECOG) performance status (PS) of 0, 74% had an ECOG PS of 1; and 70% of patients were current or previous smokers. Sixty-five percent of patients had non-squamous histology, 5% had known EGFR mutations, 1.6% had known ALK rearrangements, 36% had known PD-L1 positive tumors, 16% had asymptomatic CNS metastases at baseline. Eighty percent of patients had received only one prior therapeutic regimen for NSCLC.

At the primary analysis, the confirmed ORR was 9% (95% CI: 5, 13) in the subcutaneous TECENTRIQ HYBREZA arm and 8% (95% CI: 4, 14) in the intravenous atezolizumab arm. After further follow up, no notable differences in PFS and OS were observed between patients who received subcutaneous TECENTRIQ HYBREZA and patients who received intravenous atezolizumab.

NSCLC Trials - Intravenous Atezolizumab

The effectiveness of TECENTRIQ HYBREZA has been established for:

- adjuvant treatment (following tumor resection and platinum-based chemotherapy) in adult patients with stage II to IIIA NSCLC whose tumors have PD-L1 expression on ≥ 1% of tumor cells (IMpower010 study).
- first-line treatment of adult patients with metastatic NSCLC whose tumors have high PD-L1 expression (PD-L1 stained ≥ 50% of tumor cells [TC ≥ 50%] or PD-L1 stained tumor-infiltrating immune cells [IC] covering ≥ 10% of the tumor area [IC ≥ 10%]), with no EGFR or ALK genomic tumor aberrations (IMpower110 study).
- first-line treatment of adult patients with metastatic non-squamous NSCLC with no EGFR or ALK genomic tumor aberrations (IMpower150 study).
- first-line treatment of adult patients with metastatic non-squamous NSCLC with no EGFR or ALK genomic tumor aberrations (IMpower130 study).
- first-line treatment of adult patients with metastatic NSCLC whose tumors have high PD-L1 expression, with no EGFR or ALK genomic tumor aberrations (OAK study).

Use of TECENTRIQ HYBREZA for these NSCLC indications is supported by evidence from the adequate and well-controlled studies conducted with intravenous atezolizumab in these NSCLC populations and pharmacokinetics data that demonstrated comparable exposures to atezolizumab between TECENTRIQ HYBREZA and intravenous atezolizumab in the IMscin001 trial [see Adverse Reactions (6.1), Clinical Pharmacology (12.3), and Clinical Studies (14.1)]. Below is a description of the efficacy results of these adequate and well-controlled studies of intravenous atezolizumab in these NSCLC populations.

Adjuvant Treatment of Early-stage NSCLC

IMpower010

The efficacy of intravenous atezolizumab was evaluated in IMpower010 (NCT02486718), a multi-center, randomized, open-label trial for the adjuvant treatment of patients with NSCLC who had complete tumor resection and were eligible to receive cisplatin-based adjuvant chemotherapy. Eligible patients were required to have Stage IB (tumors ≥ 4 cm) – Stage IIIA NSCLC per the Union for International Cancer Control/American Joint Committee on Cancer staging system, 7th edition. Patients were excluded if they had a history of autoimmune disease; a history of idiopathic pulmonary fibrosis, organizing pneumonia, drug-induced pneumonitis, idiopathic pneumonitis, or evidence of active pneumonitis; administration of a live, attenuated vaccine within 28 days prior to randomization; administration of systemic immunostimulatory agents within 4 weeks or systemic immunosuppressive medications within 2 weeks prior to randomization.

A total of 1005 patients who had complete tumor resection and received cisplatin-based adjuvant chemotherapy were randomized (1:1) to receive intravenous atezolizumab 1200 mg intravenous infusion every 3 weeks for 16 cycles, unless disease recurrence or unacceptable toxicity occurred, or best supportive care (BSC). Randomization was stratified by sex, stage of disease, histology, and PD-L1 expression.

Tumor assessments were conducted at baseline of the randomization phase and every 4 months for the first year following Cycle 1, Day 1 and then every 6 months until year five, then annually thereafter.

The median age was 62 years (range: 26 to 84), and 67% of patients were male. The majority of patients were White (73%) and Asian (24%). Most patients were current or previous smokers (78%) and baseline Eastern Cooperative Oncology Group (ECOG) performance status in patients was 0 (55%) or 1 (44%). Overall, 12% of patients had Stage IB, 47% had Stage II and 41% had Stage IIIA disease. PD-L1 expression, defined as the percentage of tumor cells expressing PD-L1 as measured by the VENTANA PD-L1 (SP263) assay, was ≥ 1% in 53% of patients, < 1% in 44% and unknown in 2.6%.

The primary efficacy outcome measure was disease-free survival (DFS) as assessed by the investigator. The primary efficacy analysis population (n = 476) was patients with Stage II – IIIA NSCLC with PD-L1 expression on ≥ 1% of tumor cells (PD-L1 ≥ 1% TC). DFS was defined as the time from the date of randomization to the date of occurrence of any of the following: first documented recurrence of disease, new primary NSCLC, or death due to any cause, whichever occurred first. A key secondary efficacy outcome measure was overall survival (OS) in the intent-to-treat population.

At the time of the interim DFS analysis, the study demonstrated a statistically significant improvement in DFS in the PD-L1 ≥ 1% TC, Stage II – IIIA patient population.

Efficacy results are presented in Table 25 and Figure 1.

Table 25: Efficacy Results from IMpower010 in Patients with Stage II - IIIA NSCLC with PD-L1 expression ≥ 1% TC
 | Arm A: Intravenous Atezolizumab N = 248 | Arm B: Best Supportive Care N = 228
Disease-Free Survival
Number of events (%) | 88 (35) | 105 (46)
Median, months | NR | 35.3
(95% CI) | (36.1, NE) | (29.0, NE)
Hazard ratio [Stratified by stage, sex, and histology] (95% CI) | 0.66 (0.50, 0.88)
p-value | 0.004
CI = Confidence interval, NE = Not estimable, NR = Not reached

In a pre-specified secondary subgroup analysis of patients with PD-L1 TC ≥ 50% Stage II – IIIA NSCLC (n = 229), the median DFS was not reached (95% CI: 42.3 months, NE) for patients in the intravenous atezolizumab arm and was 35.7 months (95% CI: 29.7, NE) for patients in the best supportive care arm, with a HR of 0.43 (95% CI: 0.27, 0.68). In an exploratory subgroup analysis of patients with PD-L1 TC 1-49% Stage II – IIIA NSCLC (n = 247), the median DFS was 32.8 months (95% CI:29.4, NE) for patients in the intravenous atezolizumab arm and 31.4 months (95% CI: 24.0, NE) for patients in the best supportive care arm, with a HR of 0.87 (95% CI: 0.60, 1.26).

Figure 1: Kaplan-Meier Plot of Disease-Free Survival in IMpower010 in Patients with Stage II – IIIA NSCLC with PD-L1 expression ≥ 1% TC

At the time of the DFS interim analysis, 19% of patients in the PD-L1 ≥1% TC Stage II – IIIA patient population had died. An exploratory analysis of OS in this population resulted in a stratified HR of 0.77 (95% CI: 0.51, 1.17).

Metastatic Chemotherapy-Naïve NSCLC

IMpower110

The efficacy of intravenous atezolizumab was evaluated in IMpower110 (NCT02409342), a multicenter, international, randomized, open-label trial in patients with stage IV NSCLC whose tumors express PD-L1 (PD-L1 stained ≥ 1% of tumor cells [TC ≥ 1%] or PD-L1 stained tumor-infiltrating immune cells [IC] covering ≥ 1% of the tumor area [IC ≥ 1%]), who had received no prior chemotherapy for metastatic disease. PD-L1 tumor status was determined based on immunohistochemistry (IHC) testing using the VENTANA PD-L1 (SP142) Assay. The evaluation of efficacy is based on the subgroup of patients with high PD-L1 expression (TC ≥ 50% or IC ≥ 10%), excluding those with EGFR or ALK genomic tumor aberrations. The trial excluded patients with a history of autoimmune disease, administration of a live attenuated vaccine within 28 days prior to randomization, active or untreated CNS metastases, administration of systemic immunostimulatory agents within 4 weeks or systemic immunosuppressive medications within 2 weeks prior to randomization.

Randomization was stratified by sex, ECOG performance status, histology (non-squamous vs. squamous) and PD-L1 expression (TC ≥ 1% and any IC vs. TC < 1% and IC ≥ 1%). Patients were randomized (1:1) to receive one of the following treatment arms:

- Arm A: Intravenous atezolizumab 1200 mg every 3 weeks until disease progression or unacceptable toxicity
- Arm B: Platinum-based chemotherapy

Arm B platinum-based chemotherapy regimens for non-squamous NSCLC consisted of cisplatin (75 mg/m²) and pemetrexed (500 mg/m²) OR carboplatin (AUC 6 mg/mL/min) and pemetrexed (500 mg/m²) on Day 1 of each 21-day cycle for a maximum of 4 or 6 cycles followed by pemetrexed (500 mg/m²) until disease progression or unacceptable toxicity.

Arm B platinum-based chemotherapy regimens for squamous NSCLC consisted of cisplatin (75 mg/m²) on Day 1 with gemcitabine (1250 mg/m2) on Days 1 and 8 of each 21-day cycle OR carboplatin (AUC 5 mg/mL/min) on Day 1 with gemcitabine (1000 mg/m^2) on Days 1 and 8 of each 21-day cycle for a maximum of 4 or 6 cycles followed by best supportive care until disease progression or unacceptable toxicity.

Administration of intravenous atezolizumab was permitted beyond RECIST-defined disease progression. Tumor assessments were conducted every 6 weeks for the first 48 weeks following Cycle 1, Day 1 and then every 9 weeks thereafter. Tumor specimens were evaluated prospectively using the VENTANA PD-L1 (SP142) Assay at a central laboratory and the results were used to define subgroups for pre-specified analyses.

The major efficacy outcome measure was overall survival (OS) sequentially tested in the following subgroups of patients, excluding those with EGFR or ALK genomic tumor aberrations: TC ≥ 50% or IC ≥ 10%; TC ≥ 5% or IC ≥ 5%; and TC ≥ 1% or IC ≥ 1%.

Among the 205 chemotherapy-naïve patients with stage IV NSCLC with high PD-L1 expression (TC ≥ 50% or IC ≥ 10%) excluding those with EGFR or ALK genomic tumor aberrations, the median age was 65.0 years (range: 33 to 87), and 70% of patients were male. The majority of patients were White (82%) and Asian (17%). Baseline ECOG performance status was 0 (36%) or 1 (64%); 88% were current or previous smokers; and 76% of patients had non-squamous disease while 24% of patients had squamous disease.

The trial demonstrated a statistically significant improvement in OS for patients with high PD-L1 expression (TC ≥ 50% or IC ≥ 10%) at the time of the OS interim analysis. There was no statistically significant difference in OS for the other two PD-L1 subgroups (TC ≥ 5% or IC ≥ 5%; and TC ≥ 1% or IC ≥ 1%) at the interim or final analyses. Efficacy results for patients with NSCLC with high PD-L1 expression are presented in Table 26 and Figure 2.

Table 26: Efficacy Results from IMpower110 in Patients with NSCLC with High PD-L1 Expression (TC ≥ 50% or IC ≥ 10%) and without EGFR or ALK Genomic Tumor Aberrations
 | Arm A: Intravenous Atezolizumab | Arm B: Platinum-Based Chemotherapy
 | N = 107 | N = 98
Overall Survival [Based on OS interim analysis. The median survival follow-up time in patients was 15.7 months]
Deaths (%) | 44 (41%) | 57 (58%)
Median, months | 20.2 | 13.1
(95% CI) | (16.5, NE) | (7.4, 16.5)
Hazard ratio [Stratified by sex and ECOG performance status] (95% CI) | 0.59 (0.40, 0.89)
p-value [Based on the stratified log-rank test compared to Arm A] | 0.0106 [Compared to the allocated alpha of 0.0413 (two-sided) for this interim analysis]
CI = confidence interval; NE = not estimable

Figure 2: Kaplan-Meier Plot of Overall Survival in IMpower110 in Patients with NSCLC with High PD-L1 Expression (TC ≥ 50% or IC ≥ 10%) and without EGFR or ALK Genomic Tumor Aberrations

Investigator-assessed PFS showed an HR of 0.63 (95% CI: 0.45, 0.88), with median PFS of 8.1 months (95% CI: 6.8, 11.0) in the intravenous atezolizumab arm and 5 months (95% CI: 4.2, 5.7) in the platinum-based chemotherapy arm. The investigator-assessed confirmed ORR was 38% (95% CI: 29%, 48%) in the intravenous atezolizumab arm and 29% (95% CI: 20%, 39%) in the platinum-based chemotherapy arm.

First-Line Metastatic Non-squamous NSCLC

IMpower150

The efficacy of intravenous atezolizumab with bevacizumab, paclitaxel, and carboplatin was evaluated in IMpower150 (NCT02366143), a multicenter, international, randomized (1:1:1), open-label trial in patients with metastatic non-squamous NSCLC. Patients with stage IV non-squamous NSCLC who had received no prior chemotherapy for metastatic disease but could have received prior EGFR or ALK kinase inhibitor if appropriate, regardless of PD-L1 or T-effector gene (tGE) status and ECOG performance status 0 or 1 were eligible. The trial excluded patients with a history of autoimmune disease, administration of a live attenuated vaccine within 28 days prior to randomization, active or untreated CNS metastases, administration of systemic immunostimulatory agents within 4 weeks or systemic immunosuppressive medications within 2 weeks prior to randomization, or clear tumor infiltration into the thoracic great vessels or clear cavitation of pulmonary lesions as seen on imaging. Randomization was stratified by sex, presence of liver metastases, and PD-L1 expression status on tumor cells (TC) and tumor-infiltrating immune cells (IC) as follows: TC3 and any IC vs. TC0/1/2 and IC2/3 vs. TC0/1/2 and IC0/1. Patients were randomized to one of the following three treatment arms:

- Arm A: intravenous atezolizumab 1200 mg, paclitaxel 175 mg/m² or 200 mg/m² and carboplatin AUC 6 mg/mL/min on Day 1 of each 21-day cycle for a maximum of 4 or 6 cycles
- Arm B: intravenous atezolizumab 1200 mg, bevacizumab 15 mg/kg, paclitaxel 175 mg/m² or 200 mg/m², and carboplatin AUC 6 mg/mL/min on Day 1 of each 21-day cycle for a maximum of 4 or 6 cycles
- Arm C: bevacizumab 15 mg/kg, paclitaxel 175 mg/m² or 200 mg/m², and carboplatin AUC 6 mg/mL/min on Day 1 of each 21-day cycle for a maximum of 4 or 6 cycles

Patients who had not experienced disease progression following the completion or cessation of platinum-based chemotherapy, received:

- Arm A: intravenous atezolizumab 1200 mg intravenously on Day 1 of each 21-day cycle until disease progression or unacceptable toxicity
- Arm B: intravenous atezolizumab 1200 mg and bevacizumab 15 mg/kg intravenously on Day 1 of each 21-day cycle until disease progression or unacceptable toxicity
- Arm C: bevacizumab 15 mg/kg intravenously on Day 1 of each 21-day cycle until disease progression or unacceptable toxicity

Tumor assessments were conducted every 6 weeks for the first 48 weeks following Cycle 1, Day 1 and then every 9 weeks thereafter. Tumor specimens were evaluated prior to randomization for PD-L1 tumor expression using the VENTANA PD-L1 (SP142) assay at a central laboratory. Tumor tissue was collected at baseline for expression of tGE signature and evaluation was performed using a clinical trial assay in a central laboratory prior to the analysis of efficacy outcome measures.

Major efficacy outcome measures for comparison of Arms B and C were progression free survival (PFS) by RECIST v1.1 in the tGE-WT (patients with high expression of T-effector gene signature [tGE], excluding those with EGFR- and ALK-positive NSCLC [WT]) and in the ITT-WT subpopulations and overall survival (OS) in the ITT-WT subpopulation. Additional efficacy outcome measures for comparison of Arms B and C or Arms A and C were PFS and OS in the ITT population, OS in the tGE-WT subpopulation, and ORR/DoR in the tGE-WT and ITT-WT subpopulations.

A total of 1202 patients were enrolled across the three arms of whom 1045 were in the ITT-WT subpopulation and 447 were in the tGE-WT subpopulation. The demographic information is limited to the 800 patients enrolled in Arms B and C where efficacy has been demonstrated. The median age was 63 years (range: 31 to 90), and 60% of patients were male. The majority of patients were White (82%), 13% of patients were Asian, 10% were Hispanic, and 2% of patients were Black. Clinical sites in Asia (enrolling 13% of the study population) received paclitaxel at a dose of 175 mg/m2 while the remaining 87% received paclitaxel at a dose of 200 mg/m2. Approximately 14% of patients had liver metastases at baseline, and most patients were current or previous smokers (80%). Baseline ECOG performance status was 0 (43%) or 1 (57%). PD-L1 was TC3 and any IC in 12%, TC0/1/2 and IC2/3 in 13%, and TC0/1/2 and IC0/1 in 75%. The demographics for the 696 patients in the ITT-WT subpopulation were similar to the ITT population except for the absence of patients with EGFR- or ALK-positive NSCLC.

The trial demonstrated a statistically significant improvement in PFS between Arms B and C in both the tGE-WT and ITT-WT subpopulations, but did not demonstrate a significant difference for either subpopulation between Arms A and C based on the final PFS analyses. In the interim analysis of OS, a statistically significant improvement was observed for Arm B compared to Arm C, but not for Arm A compared to Arm C. Efficacy results for the ITT-WT subpopulation are presented in Table 27 and Figure 3.

Table 27: Efficacy Results in ITT-WT Population in IMpower150
 | Arm C: Bevacizumab, Paclitaxel and Carboplatin | Arm B: Intravenous Atezolizumab with Bevacizumab, Paclitaxel, and Carboplatin | Arm A: Intravenous Atezolizumab with Paclitaxel, and Carboplatin
 | N = 337 | N = 359 | N = 349
Overall Survival [Based on OS interim analysis]
Deaths (%) | 197 (59%) | 179 (50%) | 179 (51%)
Median, months | 14.7 | 19.2 | 19.4
(95% CI) | (13.3, 16.9) | (17.0, 23.8) | (15.7, 21.3)
Hazard ratio [Stratified by sex, presence of liver metastases, and PD-L1 expression status on TC and IC] (95% CI) | --- | 0.78 (0.64, 0.96) | 0.84 (0.72, 1.08)
p-value [Based on the stratified log-rank test compared to Arm C] | --- | 0.016 [Compared to the allocated α=0.0174 (two sided) for this interim analysis] | 0.204 [Compared to the allocated α=0.0128 (two sided) for this interim analysis]
Progression-Free Survival [As determined by independent review facility (IRF) per RECIST v1.1 (Response Evaluation Criteria in Solid Tumors v1.1)]
Number of events (%) | 247 (73%) | 247 (69%) | 245 (70%)
Median, months | 7.0 | 8.5 | 6.7
(95% CI) | (6.3, 7.9) | (7.3, 9.7) | (5.6, 6.9)
Hazard ratio (95% CI) | --- | 0.71 (0.59, 0.85) | 0.94 (0.79, 1.13)
p-value | --- | 0.0002 [Compared to the allocated α=0.006 (two sided) for the final PFS analysis] | 0.5219
Objective Response Rate
Number of responders (%) | 142 (42%) | 196 (55%) | 150 (43%)
(95% CI) | (37, 48) | (49, 60) | (38, 48)
Complete Response | 3 (1%) | 14 (4%) | 9 (3%)
Partial Response | 139 (41%) | 182 (51%) | 141 (40%)
Duration of Response | n = 142 | n = 196 | n = 150
Median, months | 6.5 | 10.8 | 9.5
(95% CI) | (5.6, 7.6) | (8.4, 13.9) | (7.0, 13.0)
CI = confidence interval

Figure 3: Kaplan-Meier Curves for Overall Survival in ITT-WT Population in IMpower150

Exploratory analyses showed that the subset of patients in the four drug regimen arm who were ADA positive by week 4 (30%) appeared to have similar efficacy (effect on overall survival) as compared to patients who tested negative for treatment-emergent ADA by week 4 (70%) [see, Clinical Pharmacology (12.6)]. In an exploratory analysis, propensity score matching was conducted to compare ADA positive patients in the intravenous atezolizumab, bevacizumab, paclitaxel, and carboplatin arm with a matched population in the bevacizumab, paclitaxel, and carboplatin arm. Similarly, ADA negative patients in the intravenous atezolizumab, bevacizumab, paclitaxel, and carboplatin arm were compared with a matched population in the bevacizumab, paclitaxel, and carboplatin arm. Propensity score matching factors were: baseline sum of longest tumor size (BSLD), baseline ECOG, baseline albumin, baseline LDH, sex, tobacco history, metastatic site, TC level, and IC level. The hazard ratio comparing the ADA-positive subgroup with its matched control was 0.69 (95% CI: 0.44, 1.07). The hazard ratio comparing the ADA-negative subgroup with its matched control was 0.64 (95% CI: 0.46, 0.90).

IMpower130

The efficacy of intravenous atezolizumab with paclitaxel protein-bound and carboplatin was evaluated in IMpower130 (NCT02367781), a multicenter, randomized (2:1), open-label trial in patients with stage IV non-squamous NSCLC. Patients with Stage IV non-squamous NSCLC who had received no prior chemotherapy for metastatic disease, but could have received prior EGFR or ALK kinase inhibitor, if appropriate, were eligible. The trial excluded patients with history of autoimmune disease, administration of live attenuated vaccine within 28 days prior to randomization, administration of immunostimulatory agents within 4 weeks or systemic immunosuppressive medications within 2 weeks prior to randomization, and active or untreated CNS metastases. Randomization was stratified by sex, presence of liver metastases, and PD-L1 tumor expression according to the VENTANA PD-L1 (SP142) assay as follows: TC3 and any IC vs. TC0/1/2 and IC2/3 vs. TC0/1/2 and IC0/1. Patients were randomized to one of the following treatment regimens:

- Intravenous atezolizumab 1200 mg on Day 1, paclitaxel protein-bound 100 mg/m² on Days 1, 8, and 15, and carboplatin AUC 6 mg/mL/min on Day 1 of each 21-day cycle for a maximum of 4 or 6 cycles followed by intravenous atezolizumab 1200 mg once every 3 weeks until disease progression or unacceptable toxicity, or
- Paclitaxel protein-bound 100 mg/m² on Days 1, 8 and 15 and carboplatin AUC 6 mg/mL/min on Day 1 of each 21-day cycle for a maximum of 4 or 6 cycles followed by best supportive care or pemetrexed.

Tumor assessments were conducted every 6 weeks for the first 48 weeks, then every 9 weeks thereafter. Major efficacy outcome measures were PFS by RECIST v1.1 and OS in the subpopulation of patients evaluated for and documented to have no EGFR or ALK genomic tumor aberrations (ITT-WT).

A total of 724 patients were enrolled; of these, 681 (94%) were in the ITT-WT population. The median age was 64 years (range: 18 to 86) and 59% were male. The majority of patients were White (90%), 2% of patients were Asian, 5% were Hispanic, and 4% were Black. Baseline ECOG performance status was 0 (41%) or 1 (58%). Most patients were current or previous smokers (90%). PD-L1 tumor expression was TC0/1/2 and IC0/1 in 73%; TC3 and any IC in 14%; and TC0/1/2 and IC2/3 in 13%.

Efficacy results for the ITT-WT population are presented in Table 28 and Figure 4.

Table 28: Efficacy Results from IMpower130
 | Intravenous Atezolizumab with Paclitaxel Protein-Bound and Carboplatin | Paclitaxel Protein-Bound and Carboplatin
Overall Survival [Based on OS interim analysis] | n = 453 | n = 228
Deaths (%) | 228 (50%) | 131 (57%)
Median, months | 18.6 | 13.9
(95% CI) | (15.7, 21.1) | (12.0, 18.7)
Hazard ratio [Stratified by sex and PD-L1 tumor expression on tumor cells (TC) and tumor infiltrating cells (IC)] (95% CI) | 0.80 (0.64, 0.99)
p-value [Based on the stratified log-rank test] | 0.0384 [Compared to the allocated α=0.0428 (two sided) for this interim analysis]
Progression-Free Survival [As determined by independent review facility (IRF) per RECIST v1.1 (Response Evaluation Criteria in Solid Tumors v1.1)] | n = 453 | n = 228
Number of events (%) | 330 (73%) | 177 (78%)
Median, months | 7.2 | 6.5
(95% CI) | (6.7, 8.3) | (5.6, 7.4)
Hazard ratio (95% CI) | 0.75 (0.63, 0.91)
p-value | 0.0024 [Compared to the allocated α=0.006 (two sided) for the final PFS analysis]
Overall Response Rate, [Confirmed response] | n = 453 | n = 228
Number of responders (%) | 207 (46%) | 74 (32%)
(95% CI) | (41, 50) | (26, 39)
Complete Response | 22 (5%) | 2 (1%)
Partial Response | 185 (41%) | 72 (32%)
Duration of Response, | n = 207 | n = 74
Median, months | 10.8 | 7.8
(95% CI) | (9.0, 14.4) | (6.8, 10.9)
CI = confidence interval

Figure 4: Kaplan-Meier Curves for Overall Survival in IMpower130

Previously Treated Metastatic NSCLC

OAK

The efficacy of intravenous atezolizumab was evaluated in a multicenter, international, randomized (1:1), open-label study (OAK; NCT02008227) conducted in patients with locally advanced or metastatic NSCLC whose disease progressed during or following a platinum-containing regimen. Patients with a history of autoimmune disease, symptomatic or corticosteroid-dependent brain metastases, or requiring systemic immunosuppression within 2 weeks prior to enrollment were ineligible. Randomization was stratified by PD-L1 expression tumor-infiltrating immune cells (IC), the number of prior chemotherapy regimens (1 vs. 2), and histology (squamous vs. non-squamous).

Patients were randomized to receive intravenous atezolizumab 1200 mg intravenously every 3 weeks until unacceptable toxicity, radiographic progression, or clinical progression or docetaxel 75 mg/m^2 intravenously every 3 weeks until unacceptable toxicity or disease progression. Tumor assessments were conducted every 6 weeks for the first 36 weeks and every 9 weeks thereafter. Major efficacy outcome measure was overall survival (OS) in the first 850 randomized patients and OS in the subgroup of patients with PD-L1-expressing tumors (defined as ≥ 1% PD-L1 expression on tumor cells [TC] or immune cells [IC]). Additional efficacy outcome measures were OS in all randomized patients (n = 1225), OS in subgroups based on PD-L1 expression, overall response rate (ORR), and progression free survival as assessed by the investigator per RECIST v.1.1.

Among the first 850 randomized patients, the median age was 64 years (33 to 85 years) and 47% were ≥ 65 years old; 61% were male; 70% were White and 21% were Asian; 15% were current smokers and 67% were former smokers; and 37% had baseline ECOG PS of 0 and 63% had a baseline ECOG PS of 1. Nearly all (94%) had metastatic disease, 74% had non-squamous histology, 75% had received only one prior platinum-based chemotherapy regimen, and 55% of patients had PD-L1-expressing tumors.

Efficacy results are presented in Table 29 and Figure 5

Table 29: Efficacy Results in OAK
 | Intravenous Atezolizumab | Docetaxel
Overall Survival in first 850 patients
Number of patients | N = 425 | N = 425
Deaths (%) | 271 (64%) | 298 (70%)
Median, months | 13.8 | 9.6
(95% CI) | (11.8, 15.7) | (8.6, 11.2)
Hazard ratio [Stratified by PD-L1 expression in tumor infiltrating immune cells, the number of prior chemotherapy regimens, and histology] (95% CI) | 0.74 (0.63, 0.87)
p-value [Based on the stratified log-rank test] | 0.0004 [Compared to the pre-specified allocated α of 0.03 for this analysis]
Progression-Free Survival
Number of Patients | N = 425 | N = 425
Events (%) | 380 (89%) | 375 (88%)
Progression (%) | 332 (78%) | 290 (68%)
Deaths (%) | 48 (11%) | 85 (20%)
Median, months | 2.8 | 4.0
(95% CI) | (2.6, 3.0) | (3.3, 4.2)
Hazard ratio (95% CI) | 0.95 (0.82, 1.10)
Overall Response Rate [Per RECIST v1.1 (Response Evaluation Criteria in Solid Tumors v1.1)]
Number of Patients | N = 425 | N = 425
ORR, n (%) | 58 (14%) | 57 (13%)
(95% CI) | (11%, 17%) | (10%, 17%)
Complete Response | 6 (1%) | 1 (0.2%)
Partial Response | 52 (12%) | 56 (13%)
Duration of Response | N = 58 | N = 57
Median, months | 16.3 | 6.2
(95% CI) | (10.0, NE) | (4.9, 7.6)
Overall Survival in all 1225 patients
Number of patients | N = 613 | N = 612
Deaths (%) | 384 (63%) | 409 (67%)
Median, months | 13.3 | 9.8
(95% CI) | (11.3, 14.9) | (8.9, 11.3)
Hazard ratio (95% CI) | 0.79 (0.69, 0.91)
p-value | 0.0013 [Compared to the allocated α of 0.0177 for this interim analysis based on 86% information using O'Brien-Fleming boundary]
CI = confidence interval; NE = not estimable

Figure 5: Kaplan-Meier Curves of Overall Survival in the First 850 Patients Randomized in OAK

Tumor specimens were evaluated prospectively using the VENTANA PD-L1 (SP142) Assay at a central laboratory and the results were used to define the PD-L1 expression subgroups for pre-specified analyses. Of the 850 patients, 16% were classified as having high PD-L1 expression, defined as having PD-L1 expression on ≥ 50% of TC or ≥ 10% of IC. In an exploratory efficacy subgroup analysis of OS based on PD-L1 expression, the hazard ratio was 0.41 (95% CI: 0.27, 0.64) in the high PD-L1 expression subgroup and 0.82 (95% CI: 0.68, 0.98) in patients who did not have high PD-L1 expression.

Exploratory analyses showed that the subset of patients who were ADA positive by week 4 (21%) appeared to have less efficacy (effect on overall survival) as compared to patients who tested negative for treatment-emergent ADA by week 4 (79%) [see Clinical Pharmacology (12.6)]. ADA positive patients by week 4 appeared to have similar OS compared to docetaxel-treated patients. In an exploratory analysis, propensity score matching was conducted to compare ADA positive patients in the intravenous atezolizumab arm with a matched population in the docetaxel arm and ADA negative patients in the intravenous atezolizumab arm with a matched population in the docetaxel arm. Propensity score matching factors were: baseline sum of longest tumor size (BSLD), baseline ECOG, histology (squamous vs. non-squamous), baseline albumin, baseline LDH, gender, tobacco history, metastases status (advanced or local), metastatic site, TC level, and IC level. The hazard ratio comparing the ADA positive subgroup with its matched control was 0.89 (95% CI: 0.61, 1.3). The hazard ratio comparing the ADA negative subgroup with its matched control was 0.68 (95% CI: 0.55, 0.83).

14.2 Small Cell Lung Cancer

The efficacy of TECENTRIQ HYBREZA in combination with chemotherapy for the first-line treatment of adult patients with extensive-stage small cell lung cancer (ES-SCLC) has been established in adequate and well-controlled studies of intravenous atezolizumab. Below is a description of the efficacy results of these adequate and well-controlled studies of intravenous atezolizumab in combination with chemotherapy in ES-SCLC (IMpower133 and IMforte studies).

Small Cell Lung Cancer (SCLC)

IMpower133

The efficacy of intravenous atezolizumab with carboplatin and etoposide was investigated in IMpower133 (NCT02763579), a randomized (1:1), multicenter, double-blind, placebo-controlled trial in 403 patients with ES-SCLC. IMpower133 enrolled patients with ES-SCLC who had received no prior chemotherapy for extensive stage disease and ECOG performance status 0 or 1. The trial excluded patients with active or untreated CNS metastases, history of autoimmune disease, administration of a live, attenuated vaccine within 4 weeks prior to randomization, or administration of systemic immunosuppressive medications within 1 week prior to randomization. Randomization was stratified by sex, ECOG performance status, and presence of brain metastases. Patients were randomized to receive one of the following two treatment arms:

- intravenous atezolizumab 1200 mg and carboplatin AUC 5 mg/mL/min on Day 1 and etoposide 100 mg/m^2 intravenously on Days 1, 2 and 3 of each 21-day cycle for a maximum of 4 cycles followed by intravenous atezolizumab 1200 mg once every 3 weeks until disease progression or unacceptable toxicity, or
- placebo and carboplatin AUC 5 mg/mL/min on Day 1 and etoposide 100 mg/m^2 intravenously on Days 1, 2, and 3 of each 21-day cycle for a maximum of 4 cycles followed by placebo once every 3 weeks until disease progression or unacceptable toxicity.

Administration of intravenous atezolizumab was permitted beyond RECIST-defined disease progression. Tumor assessments were conducted every 6 weeks for the first 48 weeks following Cycle 1, Day 1 and then every 9 weeks thereafter. Patients treated beyond disease progression had tumor assessment conducted every 6 weeks until treatment discontinuation.

Major efficacy outcome measures were OS and PFS as assessed by investigator per RECIST v1.1 in the intent-to-treat population. Additional efficacy outcome measures included ORR and DoR as assessed by investigator per RECIST v1.1.

A total of 403 patients were randomized, including 201 to the intravenous atezolizumab arm and 202 to the chemotherapy alone arm. The median age was 64 years (range: 26 to 90) and 65% were male. The majority of patients were White (80%); 17% were Asian, 4% were Hispanic and 1% were Black. Baseline ECOG performance status was 0 (35%) or 1 (65%); 9% of patients had a history of brain metastases, and 97% were current or previous smokers. Efficacy results are presented in Table 30 and Figure 6.

Table 30: Efficacy Results from IMpower133
 | Intravenous Atezolizumab with Carboplatin and Etoposide | Placebo with Carboplatin and Etoposide
Overall Survival | N = 201 | N = 202
Deaths (%) | 104 (52%) | 134 (66%)
Median, months | 12.3 | 10.3
(95% CI) | (10.8, 15.9) | (9.3, 11.3)
Hazard ratio [Stratified by sex and ECOG performance status] (95% CI) | 0.70 (0.54, 0.91)
p-value [Based on the stratified log-rank test] , [Compared to the allocated α of 0.0193 for this interim analysis based on 78% information using O'Brien-Fleming boundary] | 0.0069
Progression-Free Survival [As determined by investigator assessment] , [per RECIST v1.1 (Response Evaluation Criteria in Solid Tumors v1.1)] | N = 201 | N = 202
Number of events (%) | 171 (85%) | 189 (94%)
Median, months | 5.2 | 4.3
(95% CI) | (4.4, 5.6) | (4.2, 4.5)
Hazard ratio (95% CI) | 0.77 (0.62, 0.96)
p-value, [Compared to the allocated α of 0.05 for this analysis] | 0.0170
Objective Response Rate,, [Confirmed response] | N = 201 | N = 202
Number of responders (%) | 121 (60%) | 130 (64%)
(95% CI) | (53, 67) | (57, 71)
Complete Response (%) | 5 (2%) | 2 (1%)
Partial Response (%) | 116 (58%) | 128 (63%)
Duration of Response,, | N = 121 | N = 130
Median, months | 4.2 | 3.9
(95% CI) | (4.1, 4.5) | (3.1, 4.2)
CI = confidence interval

Figure 6: Kaplan-Meier Plot of Overall Survival in IMpower133

IMforte

The efficacy of intravenous atezolizumab in combination with lurbinectedin as maintenance treatment was evaluated in IMforte (NCT05091567), a randomized, multicenter, open-label study in patients with ES-SCLC. Patients were eligible if their disease had not progressed after completion of four cycles of intravenous atezolizumab, carboplatin and etoposide (induction treatment) and they had an ECOG performance status of 0 or 1. The trial excluded patients with CNS metastases, history of autoimmune disease, or administration of systemic immunosuppressive medications within 1 week prior to enrollment. Unless contraindicated, primary prophylaxis with granulocyte colony-stimulating factor (G-CSF) was mandated for patients assigned to the intravenous atezolizumab with lurbinectedin arm.

The trial randomized 483 patients who had not experienced disease progression following the completion of four cycles of intravenous atezolizumab with carboplatin and etoposide to one of the following two treatment arms:

- Intravenous atezolizumab 1200 mg IV in combination with lurbinectedin 3.2 mg/m^2 IV once every 3 weeks until disease progression or unacceptable toxicity, or
- Intravenous atezolizumab 1200 mg IV once every 3 weeks until disease progression or unacceptable toxicity

Randomization was stratified by ECOG performance status prior to randomization (0 vs. 1), lactate dehydrogenase (LDH) (≤ ULN vs. > ULN) prior to randomization, presence of liver metastases prior to initial study enrollment (yes vs. no), and prior receipt of prophylactic cranial irradiation (yes vs. no).

The major efficacy outcome measures were OS and PFS by Independent Review Facility per RECIST v1.1.

A total of 483 patients were randomized, including 242 to the intravenous atezolizumab with lurbinectedin arm and 241 to the intravenous atezolizumab arm. The median age was 66 years (range 35 to 85 years); 63% male; 82% White; 13% Asian; 0.8% were Black or African American; 7% were of Hispanic or Latino ethnicity and 98% were current or previous smokers. Baseline ECOG performance status was 0 (43%) or 1 (57%).

Efficacy results are presented in Table 31 and Figures 7 and 8.

Table 31: Efficacy Results from IMforte
 | Intravenous Atezolizumab with Lurbinectedin N=242 | Intravenous Atezolizumab N=241
Overall Survival [Measured from the time of randomization]
Deaths (%) | 113 (47%) | 136 (56%)
Median, months | 13.2 | 10.6
(95% CI) | (11.9, 16.4) | (9.5, 12.2)
Hazard ratio [Stratified by ECOG performance status, LDH level, presence of liver metastases and prior receipt of prophylactic cranial irradiation] (95% CI) | 0.73 (0.57, 0.95)
p-value [Based on the stratified log-rank test] , [Compared to the allocated alpha of 0.0313 (two-sided) for this interim OS analysis.] | 0.0174
Progression-Free Survival , [As determined by an IRF] , [per RECIST v1.1 (Response Evaluation Criteria in Solid Tumors v1.1)]
Number of events (%) | 174 (72%) | 202 (84%)
Median, months | 5.4 | 2.1
(95% CI) | (4.2, 5.8) | (1.6, 2.7)
Hazard ratio (95% CI) | 0.54 (0.43, 0.67)
p-value, [Compared to the allocated alpha of 0.001 (two- sided) for this final PFS analysis.] | <0.0001
CI=confidence interval

Figure 7: Kaplan-Meier Plot of IRF-assessed Progression-Free Survival in IMforte

Figure 8: Kaplan-Meier Plot of Overall Survival in IMforte

14.3 Hepatocellular Carcinoma

The efficacy of TECENTRIQ HYBREZA in combination with bevacizumab for the treatment of adult patients with unresectable or metastatic hepatocellular carcinoma (HCC) who have not received prior systemic therapy has been established in adequate and well-controlled studies of intravenous atezolizumab in combination with bevacizumab for HCC. Below is a description of the efficacy results of intravenous atezolizumab in combination with bevacizumab in this adequate and well-controlled HCC trial.

Hepatocellular Carcinoma

IMbrave150

The efficacy of intravenous atezolizumab in combination with bevacizumab was investigated in IMbrave150 (NCT03434379), a multicenter, international, open-label, randomized trial in patients with locally advanced unresectable and/or metastatic hepatocellular carcinoma who have not received prior systemic therapy. Randomization was stratified by geographic region (Asia excluding Japan vs. rest of world), macrovascular invasion and/or extrahepatic spread (presence vs. absence), baseline AFP (< 400 vs. ≥ 400 ng/mL), and by ECOG performance status (0 vs. 1).

A total of 501 patients were randomized (2:1) to receive either intravenous atezolizumab as an intravenous infusion of 1200 mg, followed by 15 mg/kg bevacizumab, on the same day every 3 weeks or sorafenib 400 mg given orally twice daily, until disease progression or unacceptable toxicity. Patients could discontinue either intravenous atezolizumab or bevacizumab (e.g., due to adverse events) and continue on monotherapy until disease progression or unacceptable toxicity associated with the monotherapy.

The study enrolled patients who were ECOG performance score 0 or 1 and who had not received prior systemic treatment. Patients were required to be evaluated for the presence of varices within 6 months prior to treatment, and were excluded if they had variceal bleeding within 6 months prior to treatment, untreated or incompletely treated varices with bleeding, or high risk of bleeding. Patients with Child-Pugh B or C cirrhosis, moderate or severe ascites; history of hepatic encephalopathy; a history of autoimmune disease; administration of a live, attenuated vaccine within 4 weeks prior to randomization; administration of systemic immunostimulatory agents within 4 weeks or systemic immunosuppressive medications within 2 weeks prior to randomization; or untreated or corticosteroid-dependent brain metastases were excluded. Tumor assessments were performed every 6 weeks for the first 54 weeks and every 9 weeks thereafter.

The demographics and baseline disease characteristics of the study population were balanced between the treatment arms. The median age was 65 years (range: 26 to 88) and 83% of patients were male. The majority of patients were Asian (57%) or White (35%); 40% were from Asia (excluding Japan). Approximately 75% of patients presented with macrovascular invasion and/or extrahepatic spread and 37% had a baseline AFP ≥ 400 ng/mL. Baseline ECOG performance status was 0 (62%) or 1 (38%). HCC risk factors were Hepatitis B in 48% of patients, Hepatitis C in 22%, and 31% of patients had non-viral liver disease. The majority of patients had BCLC stage C (82%) disease at baseline, while 16% had stage B, and 3% had stage A.

The major efficacy outcome measures were overall survival (OS) and independent review facility (IRF)-assessed progression free survival (PFS) per RECIST v1.1. Additional efficacy outcome measures were IRF-assessed overall response rate (ORR) per RECIST and mRECIST.

Efficacy results are presented in Table 32 and Figure 9.

Table 32: Efficacy Results from IMbrave150
 | Intravenous Atezolizumab in combination with Bevacizumab (N= 336) | Sorafenib (N=165)
Overall Survival
Number of deaths (%) | 96 (29) | 65 (39)
Median OS in months | NE | 13.2
(95% CI) | (NE, NE) | (10.4, NE)
Hazard ratio [Stratified by geographic region (Asia excluding Japan vs. rest of world), macrovascular invasion and/or extrahepatic spread (presence vs. absence), and baseline AFP (< 400 vs. ≥ 400 ng/mL)] (95% CI) | 0.58 (0.42, 0.79)
p-value [Based on two-sided stratified log-rank test; as compared to significance level 0.004 (2-sided) based on 161/312=52% information using the OBF method] | 0.0006
Progression-Free Survival [Per independent radiology review]
Number of events (%) | 197 (59) | 109 (66)
Median PFS in months (95% CI) | 6.8 (5.8, 8.3) | 4.3 (4.0, 5.6)
Hazard ratio (95% CI) | 0.59 (0.47, 0.76)
p-value | < 0.0001
Overall Response Rate, [Confirmed responses] (ORR), RECIST 1.1
Number of responders (%) | 93 (28) | 19 (12)
(95% CI) | (23, 33) | (7,17)
p-value [Based on two-sided Cochran-Mantel-Haesnszel test] | < 0.0001
Complete responses, n (%) | 22 (7) | 0
Partial responses, n (%) | 71 (21) | 19 (12)
Duration of Response, (DOR) RECIST 1.1
 | (n=93) | (n=19)
Median DOR in months | NE | 6.3
(95% CI) | (NE, NE) | (4.7, NE)
Range (months) | (1.3+, 13.4+) | (1.4+, 9.1+)
Overall Response Rate, (ORR), HCC mRECIST
Number of responders (%) | 112 (33) | 21 (13)
(95% CI) | (28, 39) | (8, 19)
p-value | < 0.0001
Complete responses, n (%) | 37 (11) | 3 (1.8)
Partial responses, n (%) | 75 (22) | 18 (11)
Duration of Response, (DOR) HCC mRECIST
 | (n=112) | (n=21)
Median DOR in months | NE | 6.3
(95% CI) | (NE, NE) | (4.9, NE)
Range (months) | (1.3+, 13.4+) | (1.4+, 9.1+)
+ Denotes a censored value
CI = confidence interval; HCC mRECIST = Modified RECIST Assessment for Hepatocellular Carcinoma;
NE = not estimable; RECIST 1.1 = Response Evaluation Criteria in Solid Tumors v1.1

Figure 9: Kaplan-Meier Plot of Overall Survival in IMbrave150

Exploratory analyses showed that the subset of patients (20%) who were ADA-positive by week 6 appeared to have reduced efficacy (effect on OS) as compared to patients (80%) who tested negative for treatment-emergent ADA by week 6 [see Clinical Pharmacology (12.6)]. ADA-positive patients by week 6 appeared to have similar overall survival compared to sorafenib-treated patients. In an exploratory analysis, inverse probability weighting was conducted to compare ADA-positive patients and ADA-negative patients in the intravenous atezolizumab and bevacizumab arm to the sorafenib arm. Inverse probability weighting factors were: baseline sum of longest tumor size (BSLD), baseline ECOG, baseline albumin, baseline LDH, sex, age, race, geographic region, weight, neutrophil-to-lymphocyte ratio, AFP (< 400 ng/mL vs ≥ 400 ng/mL), number of metastatic sites, MVI and/or EHS present at study entry, etiology (HBV vs. HCV vs. non-viral) and Child-Pugh Score (A5 vs. A6). The OS hazard ratio comparing the ADA-positive subgroup of the intravenous atezolizumab and bevacizumab arm to sorafenib was 0.93 (95% CI: 0.57, 1.53). The OS hazard ratio comparing the ADA-negative subgroup to sorafenib was 0.39 (95% CI: 0.26, 0.60).

14.4 Melanoma

The efficacy of TECENTRIQ HYBREZA in combination with cobimetinib and vemurafenib for the treatment of adult patients with BRAF V600 mutation-positive unresectable or metastatic melanoma has been established in adequate and well-controlled studies of intravenous atezolizumab in combination with bevacizumab for BRAF V600 mutation-positive unresectable or metastatic melanoma. Below is a description of the efficacy results of intravenous atezolizumab in combination with cobimetinib and vemurafenib in this adequate and well-controlled melanoma trial.

Metastatic Melanoma

IMspire150

The efficacy of intravenous atezolizumab in combination with cobimetinib and vemurafenib was evaluated in a double-blind, randomized (1:1), placebo-controlled, multicenter trial (IMspire150; NCT02908672) conducted in 514 patients. Randomization was stratified by geographic location (North America vs. Europe vs. Australia, New Zealand, and others) and baseline lactate dehydrogenase (LDH) [less than or equal to upper limit of normal (ULN) vs. greater than ULN].

Eligible patients were required to have previously untreated unresectable or metastatic BRAF V600 mutation-positive melanoma as detected by a locally available test and centrally confirmed with the FoundationOne™ assay. Patients were excluded if they had history of autoimmune disease; administration of a live, attenuated vaccine within 28 days prior to randomization; administration of systemic immunostimulatory agents within 4 weeks or systemic immunosuppressive medications within 2 weeks prior to randomization; and active or untreated CNS metastases.

Intravenous atezolizumab was initiated after patients received a 28-day treatment cycle of cobimetinib 60 mg orally once daily (21 days on/7 days off) and vemurafenib 960 mg orally twice daily Days 1-21 and 720 mg orally twice daily Days 22-28. Patients received intravenous atezolizumab 840 mg intravenous infusion over 60 minutes every 2 weeks in combination with cobimetinib 60 mg orally once daily and vemurafenib 720 mg orally twice daily, or placebo in combination with cobimetinib 60 mg orally once daily and vemurafenib 960 mg orally twice daily. Treatment continued until disease progression or unacceptable toxicity. There was no crossover at the time of disease progression. Tumor assessments were performed every 8 weeks (± 1 week) for the first 24 months and every 12 weeks (± 1 week) thereafter.

The major efficacy outcome measure was investigator-assessed progression-free survival (PFS) per RECIST v1.1. Additional efficacy outcomes included PFS assessed by an independent central review, investigator-assessed ORR, OS, and DOR.

The median age of the study population was 54 years (range: 22–88), 58% of patients were male, 95% were White, a baseline ECOG performance status of 0 (77%) or 1 (23%), 33% had elevated LDH, 94% had metastatic disease, 60% were Stage IV (M1C), 56% had less than three metastatic sites at baseline, 3% had prior treatment for brain metastases, 30% had liver metastases at baseline, and 14% had received prior adjuvant systemic therapy. Based on central testing, 74% were identified as having a V600E mutation, 11% as having V600K mutation, and 1% as having V600D or V600R mutations.

Efficacy results are summarized in Table 33 and Figure 10. Patients had a median survival follow up time of 18.9 months.

Table 33: Efficacy Results from IMspire150
 | Intravenous Atezolizumab + Cobimetinib + Vemurafenib N = 256 | Placebo + Cobimetinib + Vemurafenib N = 258
Progression-Free Survival [As determined by investigator assessment with Response Evaluation Criteria in Solid Tumors v1.1.; CI = confidence interval]
Number of events (%) | 148 (58) | 179 (69)
Median, months | 15.1 | 10.6
(95% CI) | (11.4, 18.4) | (9.3, 12.7)
Hazard ratio [Stratified by baseline LDH] (95% CI) | 0.78 (0.63, 0.97)
p-value [Based on the stratified log-rank test] | 0.0249
Overall Response Rate, [Confirmed responses]
Number of responders (%) | 170 (66) | 168 (65)
(95% CI) | (60, 72) | (59, 71)
Complete responses, n (%) | 41 (16) | 46 (18)
Partial response, n (%) | 129 (50) | 122 (47)
Duration of Response, | n = 170 | n = 168
Median, months | 20.4 | 12.5
(95% CI) | (15.1, NE) | (10.7, 16.6)

Figure 10: Kaplan-Meier Plot for Progression-Free Survival in IMspire150

At a pre-specified analysis at the time of the primary analysis of PFS, the OS data were not mature. The median OS was 28.8 months with 93 (36%) deaths in the intravenous atezolizumab plus cobimetinib and vemurafenib arm, and 25.1 months with 112 (43%) deaths in the placebo plus cobimetinib and vemurafenib arm. The hazard ratio for OS was 0.85 (95% CI: 0.64, 1.11) and the p-value was 0.2310.

14.5 Alveolar Soft Part Sarcoma

The efficacy of TECENTRIQ HYBREZA as monotherapy for the treatment of adult patients and pediatric patients 12 years of age or older with unresectable or metastatic alveolar soft part sarcoma (ASPS) has been established in adequate and well-controlled studies of intravenous atezolizumab for ASPS. Below is a description of the efficacy results of intravenous atezolizumab in this adequate and well-controlled ASPS trial.

The efficacy of intravenous atezolizumab was evaluated in study ML39345 (NCT03141684), an open-label, single-arm study, in 49 adult and pediatric patients aged 2 years and older with unresectable or metastatic ASPS. Eligible patients were required to have histologically or cytologically confirmed ASPS that was not curable by surgery, and an ECOG performance status of ≤ 2.

Patients were excluded if they had known primary central nervous system (CNS) malignancy or symptomatic CNS metastases, known clinically significant liver disease, or history of idiopathic pulmonary fibrosis, pneumonitis, organizing pneumonia, or evidence of active pneumonitis on screening chest computed tomography (CT) scan.

Adult patients received 1200 mg intravenously and pediatric patients received 15 mg/kg (up to a maximum of 1200 mg) intravenously once every 21 days until disease progression or unacceptable toxicity.

The major efficacy outcomes were Overall Response Rate (ORR) and Duration of Response (DOR) by Independent Review Committee according to Response Evaluation Criteria in Solid Tumors (RECIST) v1.1.

A total of 49 patients were enrolled. The median age of patients was 31 years (range: 12–70); 2% of adult patients (n = 47) were ≥ 65 years of age and the pediatric patients (n = 2) were ≥ 12 years of age; 51% of patients were female, 55% White, 29% Black or African American, 10% Asian; 53% had an ECOG performance status of 0 and 45% had an ECOG performance status of 1. All patients had prior surgery for ASPS and 55% received at least one prior line of treatment for ASPS; 55% received radiotherapy and 53% received chemotherapy. Of the patients who reported staging at initial diagnosis, all were Stage IV.

Efficacy results of this study are summarized in Table 34.

Table 34: Efficacy Results from Study ML39345
Endpoint | All Patients (N=49)
Overall Response Rate (95% CI) [95% CI based on Clopper-Pearson exact method.] | 24% (13, 39)
Complete responses, n | 0
Partial responses, n (%) | 12 (24)
Duration of Response
Median, month | NE
(95% CI) | (17.0, NE)
Range | 1+, 41+
Durability of response
≥ 6 months, n (%) | 8 (67%)
≥ 12 months, n (%) | 5 (42%)
CI: confidence interval; N: number of patients; +: Censored

14.6 Patient Experience

The IMscin002 study (NCT03735121) was a randomized, multi-center, open-label cross-over trial conducted in 179 patients with either PD-L1-positive early-stage NSCLC receiving adjuvant treatment or were chemotherapy-naïve with high PD-L1 stage IV NSCLC. Patients were randomized (1:1) to receive 3 cycles of TECENTRIQ HYBREZA followed by 3 cycles of intravenous atezolizumab (Arm A) or 3 cycles of intravenous atezolizumab followed by 3 cycles of TECENTRIQ HYBREZA (Arm B).

Of the 126 eligible patients, 123 (98%) completed the patient preference questionnaire at the beginning of cycle 6 or after at least two consecutive cycles of each treatment method was administered in case of treatment discontinuation prior to cycle 6. Eighty-seven of 123 patients (71%) reported preferring subcutaneous administration of TECENTRIQ HYBREZA over intravenous atezolizumab and the most common reason was that administration required less time in the clinic; 26 out of 123 patients (21%) reported preferring intravenous atezolizumab over TECENTRIQ HYBREZA and the most common reason was that it felt more comfortable during administration; and 10 out of 123 patients (8%) had no preference for the route of administration.

Patients in both arms could continue to receive treatment after the crossover period for up to 16 cycles (patients with early-stage NSCLC) or until disease progression or unacceptable toxicity (patients with stage IV NSCLC). Of the 107 patients who reached the treatment continuation period, 85 (79%) patients (42 from IV/SC and 43 from SC/IV) chose to continue treatment with the SC route of administration.

16 HOW SUPPLIED/STORAGE AND HANDLING

TECENTRIQ HYBREZA (atezolizumab and hyaluronidase-tqjs) injection for subcutaneous use is a sterile, preservative-free, clear to slightly opalescent, and colorless to slightly yellow solution. It is supplied in a carton containing:

1,875 mg and 30,000 units/15 mL (125 mg and 2,000 units/mL) in a single-dose vial (NDC 50242-933-01).

STORAGE AND HANDLING

Store vials under refrigeration at 2°C to 8°C (36°F to 46°F) in the original carton to protect from light. Do not freeze. Do not shake.

17 PATIENT COUNSELING INFORMATION

Advise the patient to read the FDA-approved patient labeling (Medication Guide).

Immune-Mediated Adverse Reactions

Inform patients of the risk of immune-mediated adverse reactions that may require corticosteroid treatment and interruption or discontinuation of TECENTRIQ HYBREZA, including:

- Pneumonitis: Advise patients to contact their healthcare provider immediately for any new or worsening cough, chest pain, or shortness of breath [see Warnings and Precautions (5.1)].
- Colitis: Advise patients to contact their healthcare provider immediately for diarrhea, blood or mucus in stools, or severe abdominal pain [see Warnings and Precautions (5.1)].
- Hepatitis: Advise patients to contact their healthcare provider immediately for jaundice, severe nausea or vomiting, pain on the right side of abdomen, lethargy, or easy bruising or bleeding [see Warnings and Precautions (5.1)].
- Endocrinopathies: Advise patients to contact their healthcare provider immediately for signs or symptoms of hypophysitis, hyperthyroidism, hypothyroidism, adrenal insufficiency, or type 1 diabetes mellitus, including diabetic ketoacidosis [see Warnings and Precautions (5.1)].
- Nephritis: Advise patients to contact their healthcare provider immediately for pelvic pain, frequent urination, or unusual swelling [see Warnings and Precautions (5.1)].
- Dermatologic Adverse Reactions: Advise patients to contact their healthcare provider immediately for generalized rash, skin eruption, or painful skin and mucous membrane lesions [see Warnings and Precautions (5.1)].
- Other Immune-Mediated Adverse Reactions: Advise patients to contact their healthcare provider immediately for signs or symptoms of other potential immune-mediated adverse reactions [see Warnings and Precautions (5.1)].

Infusion-Related Reactions

Advise patients to contact their healthcare provider immediately for signs or symptoms of infusion-related reactions [see Warnings and Precautions (5.2)].

Complications of Allogeneic HSCT after PD-1/PD-L1 Inhibitors

Follow patients closely for evidence of transplant-related complications and intervene promptly. Consider the benefits versus risks of treatment with a PD-1/PD-L1 blocking antibody prior to or after an allogeneic HSCT [see Warnings and Precautions (5.3)].

Embryo-Fetal Toxicity

Advise females of reproductive potential that TECENTRIQ HYBREZA can cause harm to a fetus and to inform their healthcare provider of a known or suspected pregnancy [see Warnings and Precautions (5.4), Use in Specific Populations (8.1, 8.3)].

Advise females of reproductive potential to use effective contraception during treatment and for 5 months after the last dose of TECENTRIQ HYBREZA [see Use in Specific Populations (8.3)].

Lactation

Advise female patients not to breastfeed while taking TECENTRIQ HYBREZA and for 5 months after the last dose [see Use in Specific Populations (8.2)].

TECENTRIQ HYBREZA® (atezolizumab and hyaluronidase-tqjs)

Manufactured by:
Genentech, Inc.
A Member of the Roche Group
1 DNA Way
South San Francisco, CA 94080-4990
U.S. License No.: 1048

TECENTRIQ HYBREZA is a registered trademark
of Genentech, Inc.
©2025 Genentech, Inc.

MEDICATION GUIDE
TECENTRIQ HYBREZA® (te-SEN-trik hye-BREEZE-uh)
(atezolizumab and hyaluronidase-tqjs)
injection, for subcutaneous use

What is the most important information I should know about TECENTRIQ HYBREZA?

TECENTRIQ HYBREZA is a medicine that may treat certain cancers by working with your immune system.
TECENTRIQ HYBREZA can cause your immune system to attack normal organs and tissues in any area of your body and can affect the way they work. These problems can sometimes become severe or life-threatening and can lead to death. You can have more than one of these problems at the same time. These problems may happen anytime during your treatment or even after your treatment has ended.

Call or see your healthcare provider right away if you develop any new or worse signs or symptoms, including:

Lung problems.

- cough

- shortness of breath

- chest pain

Intestinal problems.

- diarrhea (loose stools) or more frequent bowel movements than usual
- stools that are black, tarry, sticky, or have blood or mucus
- severe stomach-area (abdomen) pain or tenderness

Liver problems.

- yellowing of your skin or the whites of your eyes
- severe nausea or vomiting
- pain on the right side of your stomach area (abdomen)

- dark urine (tea colored)
- bleeding or bruising more easily than normal

Hormone gland problems.

- headaches that will not go away or unusual headaches
- eye sensitivity to light
- eye problems
- rapid heartbeat
- increased sweating
- extreme tiredness
- weight gain or weight loss
- feeling more hungry or thirsty than usual

- urinating more often than usual
- hair loss
- feeling cold
- constipation
- your voice gets deeper
- dizziness or fainting
- changes in mood or behavior, such as decreased sex drive, irritability, or forgetfulness

Kidney problems.

- decrease in your amount of urine
- blood in your urine

- swelling of your ankles
- loss of appetite

Skin problems.

- rash
- itching
- skin blistering or peeling

- painful sores or ulcers in mouth or nose, throat, or genital area
- fever or flu-like symptoms
- swollen lymph nodes

Problems can also happen in other organs. These are not all of the signs and symptoms of immune system problems that can happen with TECENTRIQ HYBREZA. Call or see your healthcare provider right away for any new or worse signs or symptoms, including:

- chest pain, irregular heartbeat, shortness of breath, or swelling of ankles
- confusion, sleepiness, memory problems, changes in mood or behavior, stiff neck, balance problems, tingling or numbness of the arms or legs
- double vision, blurry vision, sensitivity to light, eye pain, changes in eyesight
- persistent or severe muscle pain or weakness, muscle cramps
- low red blood cells, bruising

Infusion reactions that can sometimes be severe or life-threatening. Signs and symptoms of infusion reactions may include:

- chills or shaking
- itching or rash
- flushing
- shortness of breath or wheezing

- dizziness
- feeling like passing out
- fever
- back or neck pain

Complications, including graft-versus-host disease (GVHD), in people who have received a bone marrow (stem cell) transplant that uses donor stem cells (allogeneic). These complications can be serious and can lead to death. These complications may happen if you underwent transplantation either before or after being treated with TECENTRIQ HYBREZA. Your healthcare provider will monitor you for these complications.

Getting medical treatment right away may help keep these problems from becoming more serious.

Your healthcare provider will check you for these problems during your treatment with TECENTRIQ HYBREZA. Your healthcare provider may treat you with corticosteroid or hormone replacement medicines. Your healthcare provider may also need to delay or completely stop treatment with TECENTRIQ HYBREZA if you have severe side effects.

What is TECENTRIQ HYBREZA?

TECENTRIQ HYBREZA is a prescription medicine used to treat:

- adults with a type of lung cancer called non-small cell lung cancer (NSCLC).
  - TECENTRIQ HYBREZA may be used alone as a treatment for your lung cancer:
    - to help prevent your lung cancer from coming back after your tumor(s) has been removed by surgery and you have received platinum-based chemotherapy, and
    - you have stage 2 to stage 3A NSCLC (talk to your healthcare provider about what these stages mean), and
    - your cancer tests positive for "PD-L1."
  - TECENTRIQ HYBREZA may be used alone as your first treatment when your lung cancer:
    - has spread or grown, and
    - your cancer tests positive for "high PD-L1," and
    - your tumor does not have an abnormal "EGFR" or "ALK" gene.
  - TECENTRIQ HYBREZA may be used with the medicines bevacizumab, paclitaxel, and carboplatin as your first treatment when your lung cancer:
    - has spread or grown, and
    - is a type called "non-squamous NSCLC," and
    - your tumor does not have an abnormal "EGFR" or "ALK" gene.
  - TECENTRIQ HYBREZA may be used with the medicines paclitaxel protein-bound and carboplatin as your first treatment when your lung cancer:
    - has spread or grown, and
    - is a type called "non-squamous NSCLC," and
    - your tumor does not have an abnormal "EGFR" or "ALK" gene.
  - TECENTRIQ HYBREZA may also be used alone when your lung cancer:
    - has spread or grown, and
    - you have tried chemotherapy that contains platinum, and it did not work or is no longer working.
    - if your tumor has an abnormal "EGFR" or "ALK" gene, you should have also tried an FDA-approved therapy for tumors with these abnormal genes, and it did not work or is no longer working.
- adults with a type of lung cancer called "extensive-stage small cell lung cancer (SCLC)" which is SCLC that has spread and grown.
  - TECENTRIQ HYBREZA may be used with the chemotherapy medicines carboplatin and etoposide as your first treatment.
  - TECENTRIQ HYBREZA may be used with the medicine lurbinectedin as maintenance treatment when your lung cancer:
    - has not progressed after first treatment with TECENTRIQ HYBREZA or intravenous atezolizumab and the chemotherapy medicines carboplatin and etoposide.
- adults with a type of liver cancer called hepatocellular carcinoma (HCC). TECENTRIQ HYBREZA may be used with the medicine bevacizumab when your liver cancer:
  - has spread or cannot be removed by surgery, and
  - you have not received other medicines by mouth or injection through your vein (IV) to treat your cancer.
- adults with a type of skin cancer called melanoma. TECENTRIQ HYBREZA may be used with the medicines cobimetinib and vemurafenib when your melanoma:
  - has spread to other parts of the body or cannot be removed by surgery, and
  - has a certain type of abnormal "BRAF" gene. Your healthcare provider will perform a test to make sure this TECENTRIQ HYBREZA combination is right for you.
- adults and children (12 years of age and older and who weigh 88 pounds (40 kg) or more), with a type of soft tissue tumor (cancer) called alveolar soft part sarcoma (ASPS). TECENTRIQ HYBREZA may be used alone when your sarcoma has spread to other parts of the body or cannot be removed by surgery.

It is not known if TECENTRIQ HYBREZA is safe and effective when used in children:

- younger than 12 years of age or who weigh less than 88 pounds (40 kg) for the treatment of ASPS.
- for the treatment of NSCLC, SCLC, HCC, or melanoma.

Do not receive TECENTRIQ HYBREZA if you are allergic to hyaluronidase or any of the ingredients in TECENTRIQ HYBREZA. See the end of this Medication Guide for a complete list of ingredients in TECENTRIQ HYBREZA.

Before receiving TECENTRIQ HYBREZA, tell your healthcare provider about all of your medical conditions, including if you:

- have immune system problems such as Crohn's disease, ulcerative colitis, or lupus
- have received an organ transplant
- have received or plan to receive a stem cell transplant that uses donor stem cells (allogeneic)
- have received radiation treatment to your chest area
- have a condition that affects your nervous system, such as myasthenia gravis or Guillain-Barré syndrome
- are pregnant or plan to become pregnant. TECENTRIQ HYBREZA can harm your unborn baby. Tell your healthcare provider right away if you become pregnant or think you may be pregnant during treatment with TECENTRIQ HYBREZA.
  Females who are able to become pregnant:
  - Your healthcare provider should do a pregnancy test before you start treatment with TECENTRIQ HYBREZA.
  - You should use an effective method of birth control during your treatment and for 5 months after the last dose of TECENTRIQ HYBREZA.
- are breastfeeding or plan to breastfeed. It is not known if TECENTRIQ HYBREZA passes into your breast milk. Do not breastfeed during treatment and for 5 months after the last dose of TECENTRIQ HYBREZA.
- Tell your healthcare provider about all the medicines you take, including prescription and over-the-counter medicines, vitamins, and herbal supplements.

How will I receive TECENTRIQ HYBREZA?

- Your healthcare provider will give you TECENTRIQ HYBREZA as an injection under the skin in the thigh over about 7 minutes.
- TECENTRIQ HYBREZA is given every 3 weeks.
- Your healthcare provider will decide how many treatments you need.
- Your healthcare provider will test your blood to check you for certain side effects.
- For treatment of a type of skin cancer called melanoma, your healthcare provider will also prescribe you cobimetinib and vemurafenib. Take cobimetinib and vemurafenib exactly as your healthcare provider tells you.
- If you miss any appointments, call your healthcare provider as soon as possible to reschedule your appointment.

What are the possible side effects of TECENTRIQ HYBREZA?

TECENTRIQ HYBREZA can cause serious side effects, including:

- See "What is the most important information I should know about TECENTRIQ HYBREZA?"

The most common side effects of TECENTRIQ HYBREZA when used alone in NSCLC include:

- feeling tired or weak
- muscle or bone pain

- cough
- shortness of breath

- decreased appetite

The most common side effects observed with intravenous TECENTRIQ, which may be experienced with TECENTRIQ HYBREZA are shown below.
The most common side effects of TECENTRIQ when used alone as the first treatment for NSCLC include:

- feeling tired or weak

The most common side effects of TECENTRIQ when used alone in NSCLC that has spread or grown include:

- feeling tired or weak
- cough
- decreased appetite

- shortness of breath
- muscle or bone pain

The most common side effects of TECENTRIQ when used alone in ASPS include:

- muscle or bone pain
- feeling tired
- rash
- cough
- headache
- nausea
- high blood pressure

- vomiting
- constipation
- shortness of breath
- dizziness
- bleeding
- diarrhea
- trouble sleeping

- stomach-area (abdominal) pain
- low thyroid hormone levels
- fever
- anxiety
- irregular heartbeat (arrhythmia)
- decreased appetite

The most common side effects of TECENTRIQ when used in NSCLC with bevacizumab, paclitaxel, and carboplatin include:

- numbness, pain, tingling, or burning in your hands or feet
- feeling tired or weak
- hair loss
- muscle or bone pain

- nausea
- diarrhea
- constipation
- decreased appetite

- joint pain
- high blood pressure
- rash
- cough

The most common side effects of TECENTRIQ when used in non-squamous NSCLC with paclitaxel protein-bound and carboplatin include:

- feeling tired or weak
- nausea
- diarrhea
- muscle or bone pain
- constipation

- numbness, pain, tingling, or burning in your hands or feet
- hair loss
- shortness of breath

- decreased appetite
- cough
- vomiting
- rash

The most common side effects of TECENTRIQ when used in SCLC with carboplatin and etoposide include:

- feeling tired or weak
- nausea

- hair loss
- decreased appetite

- constipation
- vomiting

The most common side effects of TECENTRIQ when used in SCLC with lurbinectedin include:

- low white and red blood cell counts
- nausea
- feeling tired or weak
- increased liver function blood tests

- decreased sodium and calcium
- increased kidney function blood test (creatinine)
- muscle and joint (musculoskeletal) pain

- decreased appetite
- diarrhea
- vomiting
- constipation
- cough
- shortness of breath

The most common side effects of TECENTRIQ when used in HCC with bevacizumab include:

- high blood pressure

- feeling tired or weak

- too much protein in the urine

The most common side effects of TECENTRIQ when used in melanoma with cobimetinib and vemurafenib include:

- skin rash
- joint, muscle or bone pain
- feeling tired or weak
- liver injury

- fever
- nausea
- itching
- swelling of legs or arms

- mouth swelling (sometimes with sores)
- low thyroid hormone levels
- sunburn or sun sensitivity

TECENTRIQ HYBREZA may cause fertility problems in females, which may affect the ability to have children. Talk to your healthcare provider if you have concerns about fertility.

These are not all the possible side effects of TECENTRIQ HYBREZA.

Call your doctor for medical advice about side effects. You may report side effects to FDA at 1-800-FDA-1088.

General information about the safe and effective use of TECENTRIQ HYBREZA.

Medicines are sometimes prescribed for purposes other than those listed in a Medication Guide. You can ask your pharmacist or healthcare provider for information about TECENTRIQ HYBREZA that is written for health professionals.

What are the ingredients in TECENTRIQ HYBREZA?

Active ingredients: atezolizumab and hyaluronidase-tqjs

Inactive ingredients: acetic acid, histidine, methionine, polysorbate 20, sucrose, water for injection.
Manufactured by: Genentech, Inc., A Member of the Roche Group, 1 DNA Way, South San Francisco, CA 94080-4990 USA
U.S. License No.: 1048 TECENTRIQ HYBREZA is a registered trademark of Genentech, Inc.
For more information, call 1-877-436-3683 or go to www.TECENTRIQHYBREZA.com.

This Medication Guide has been approved by the U.S. Food and Drug Administration.

Revised: 11/2025

PRINCIPAL DISPLAY PANEL - 15 mL Vial Box

NDC 50242-933-01

Tecentriq Hybreza™
(atezolizumab and
hyaluronidase-tqjs)
Injection

1,875 mg and 30,000 units/15 mL
(125 mg and 2,000 units/mL)

For subcutaneous use only

Single-Dose Vial
Discard Unused Portion

Attention Pharmacist: Dispense the
accompanying Medication Guide to
each patient.

1 vial

Rx only
Genentech

11001667